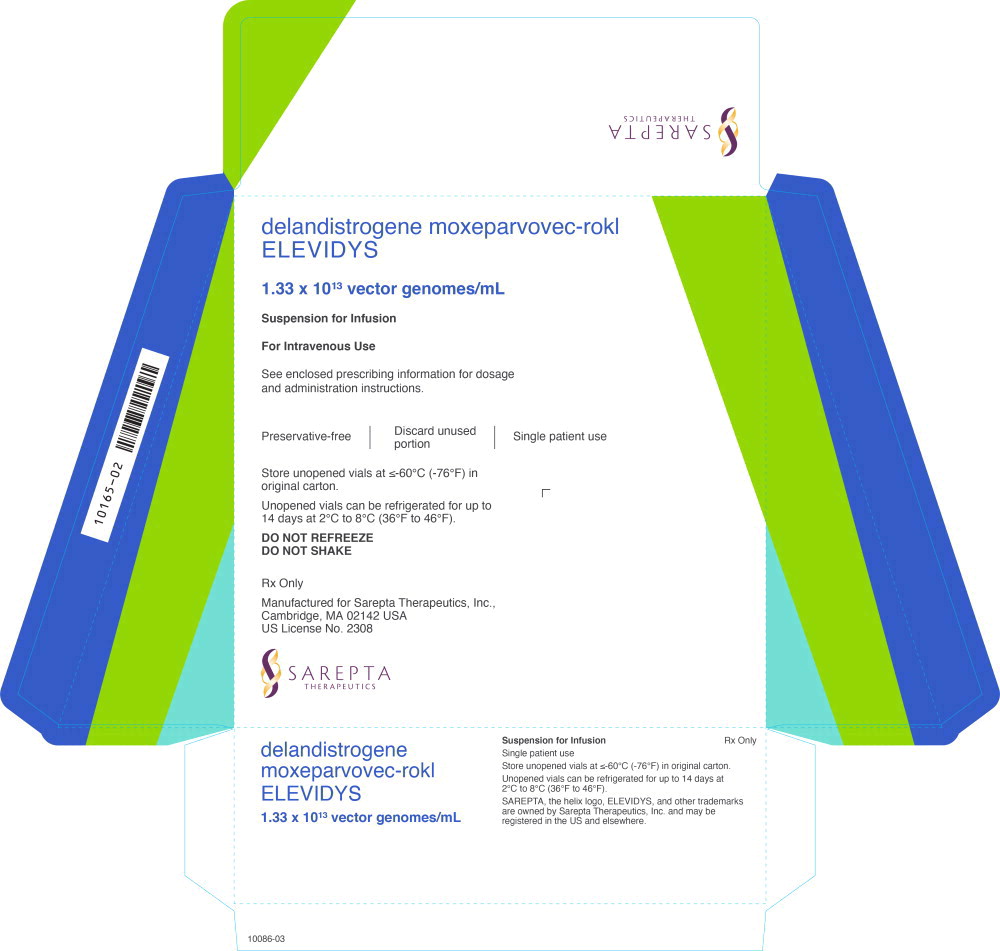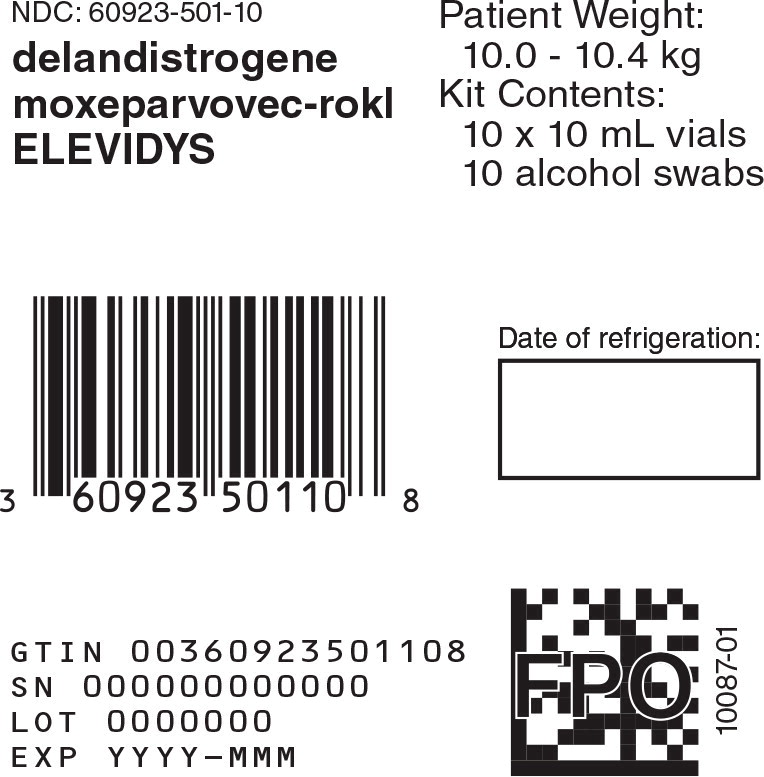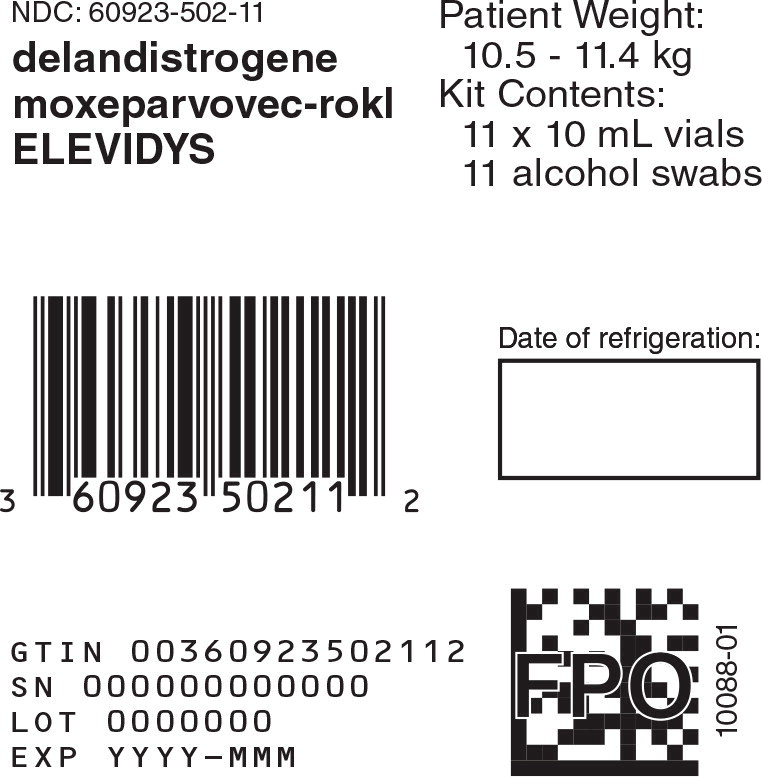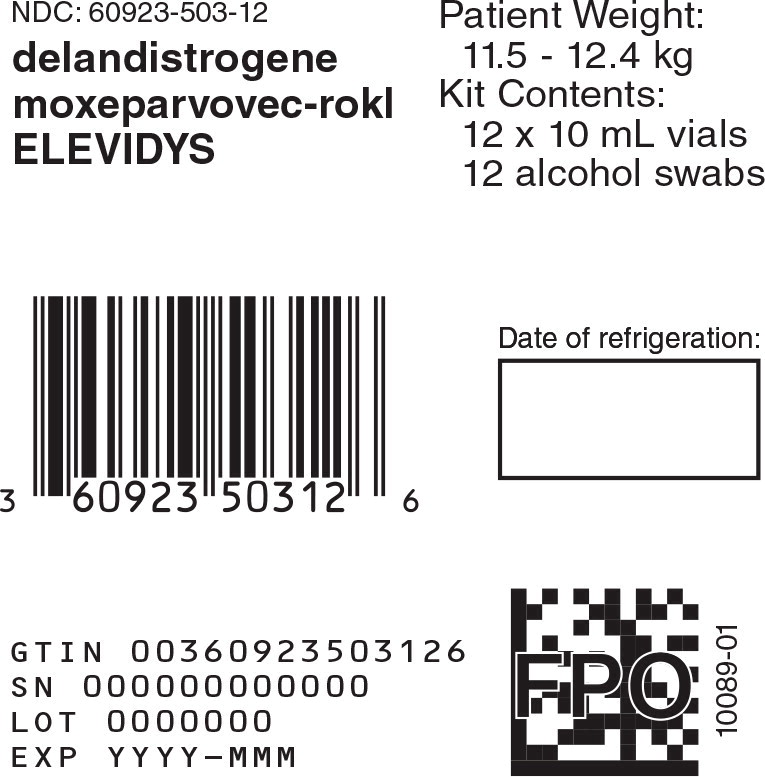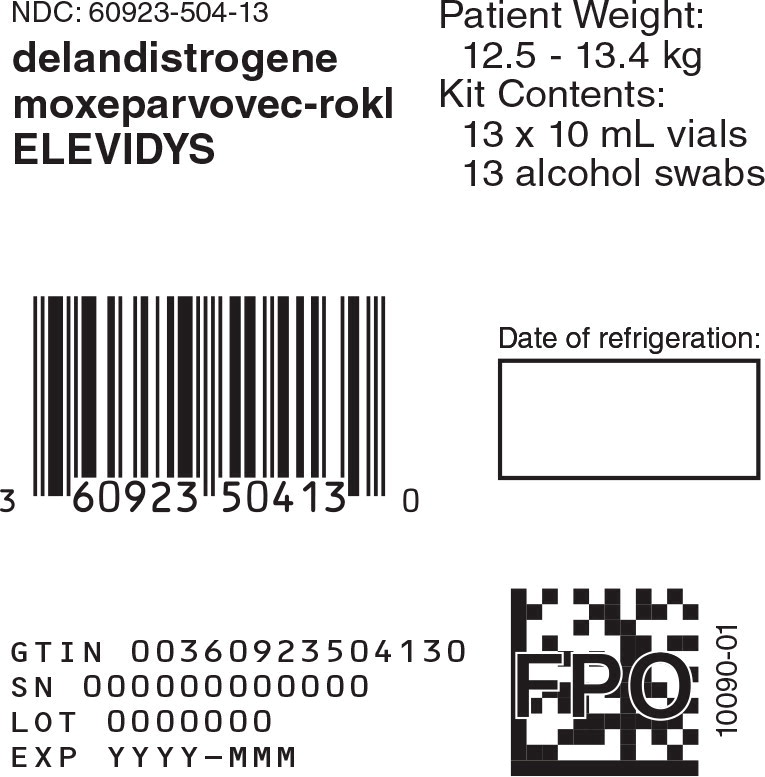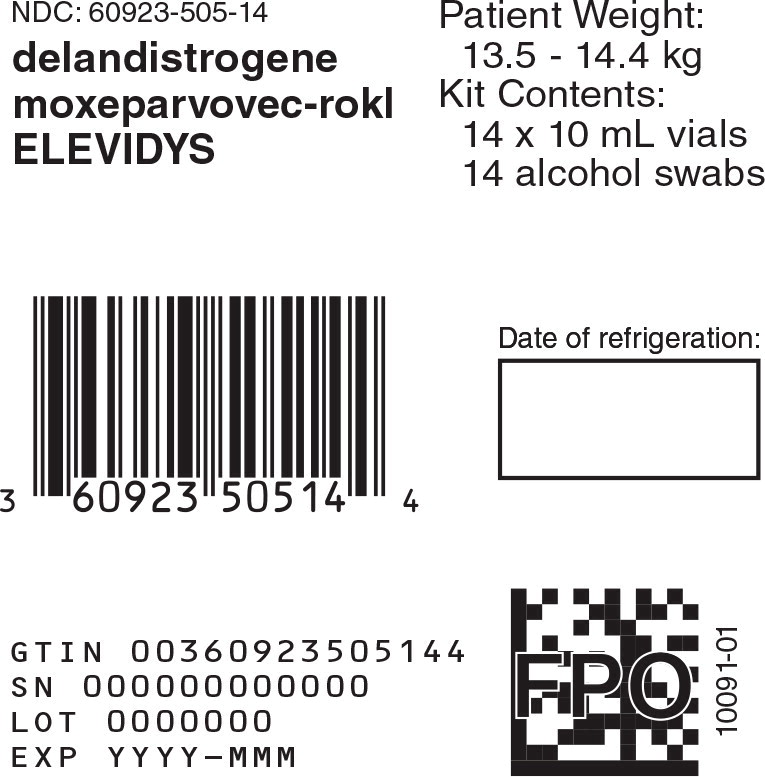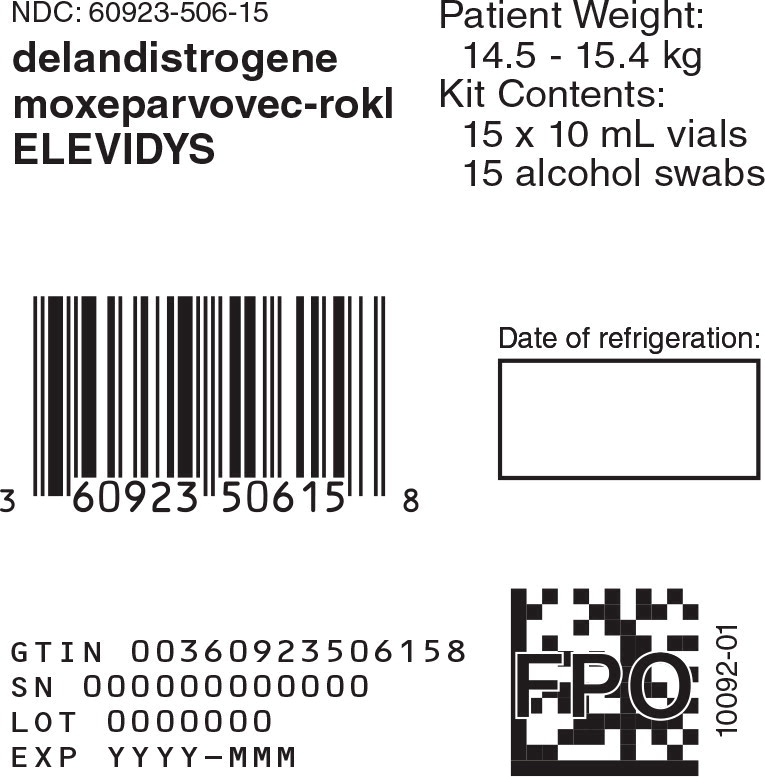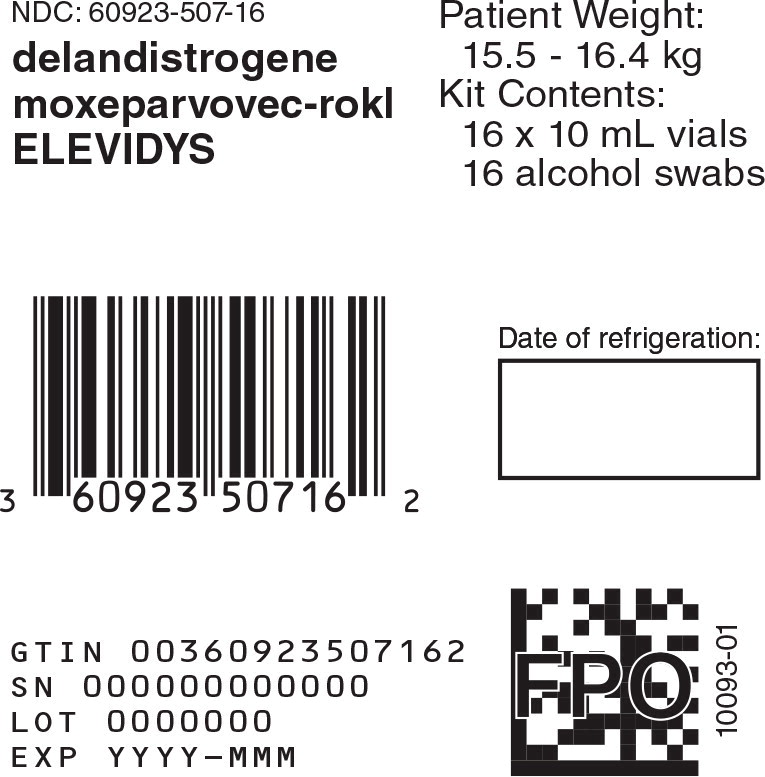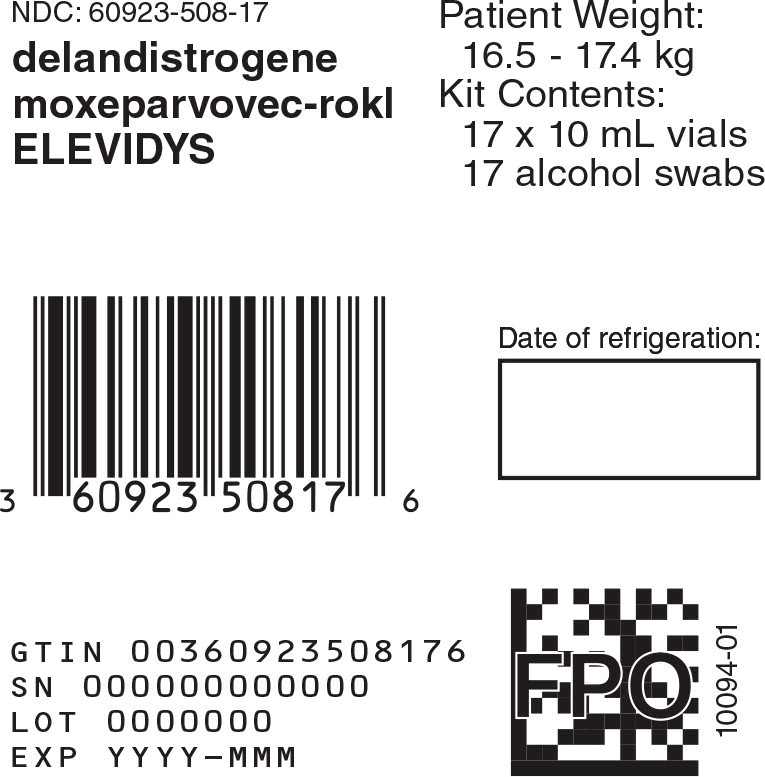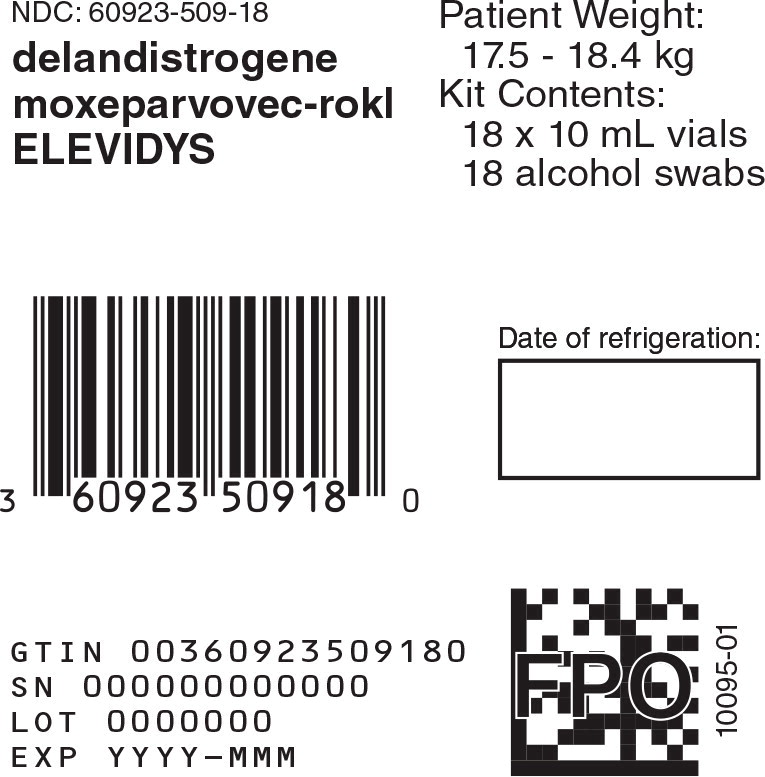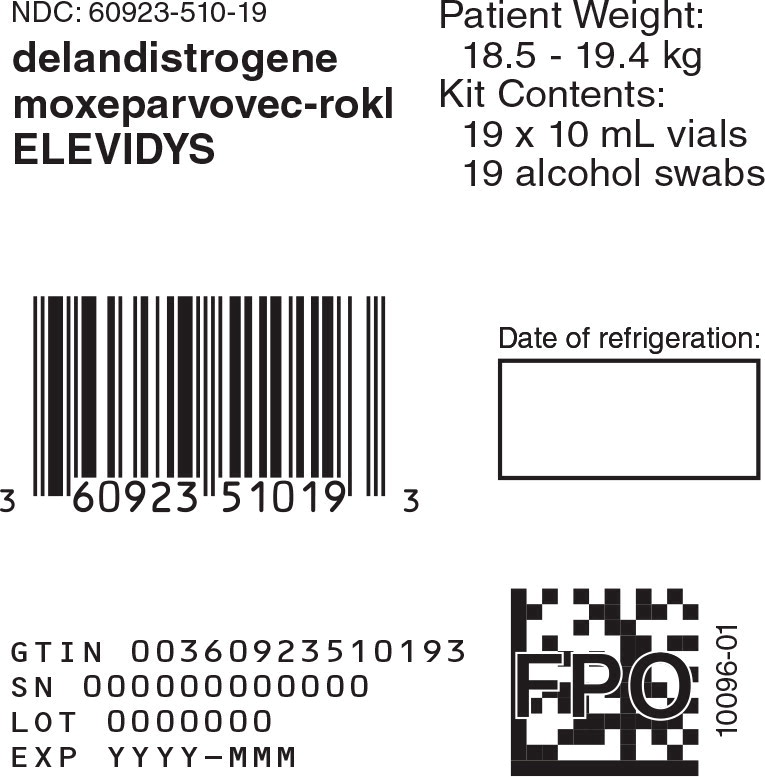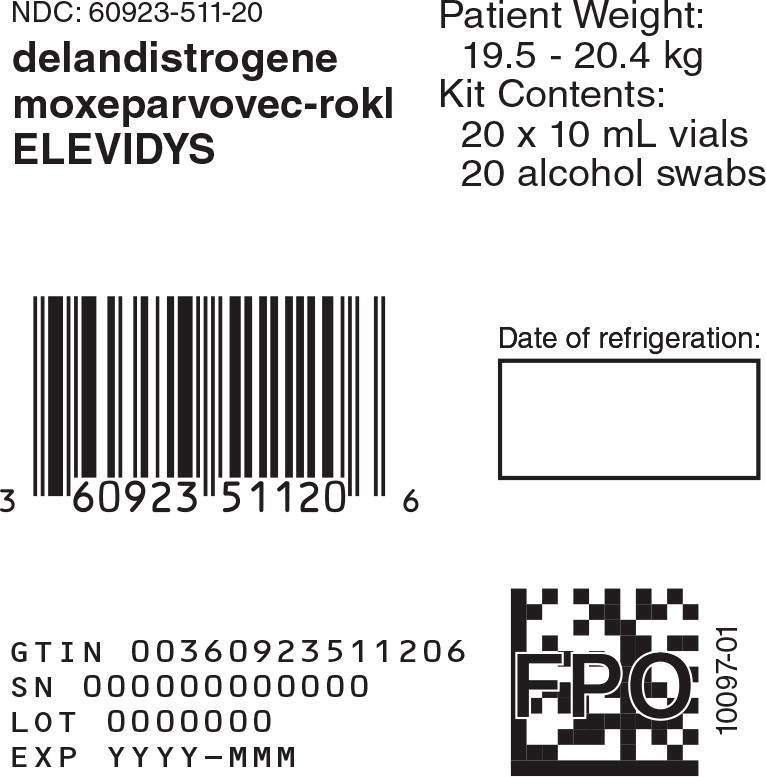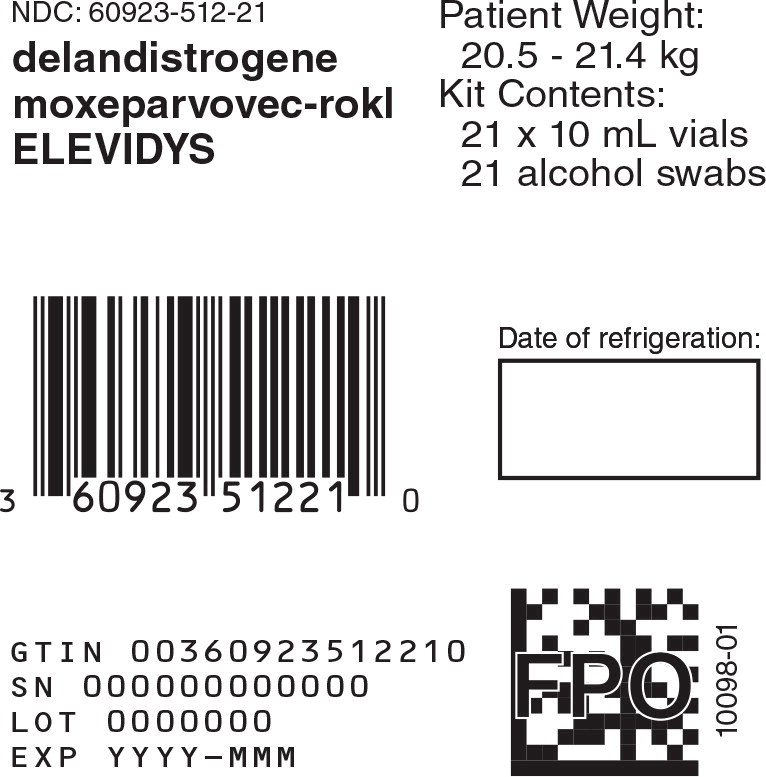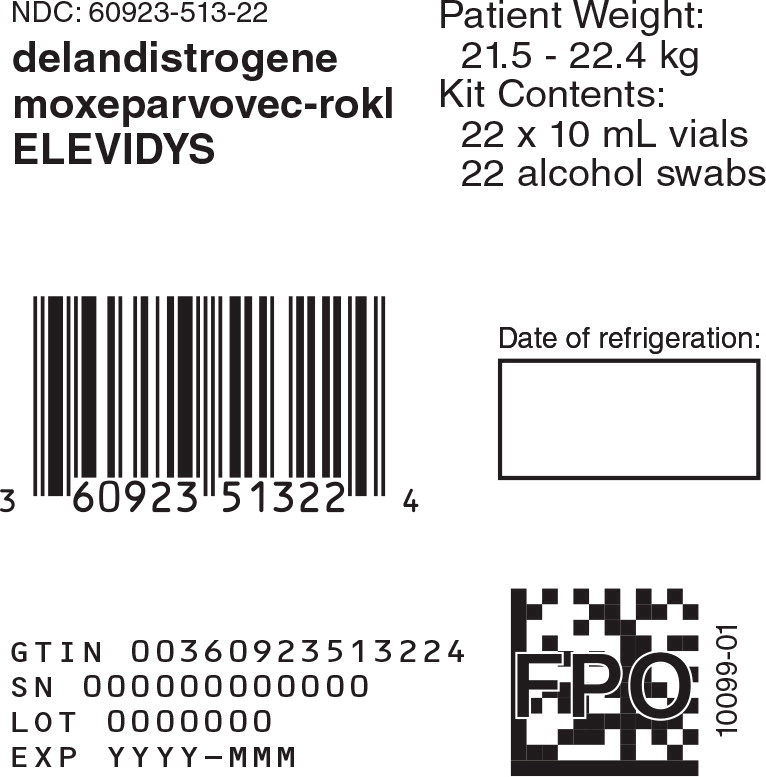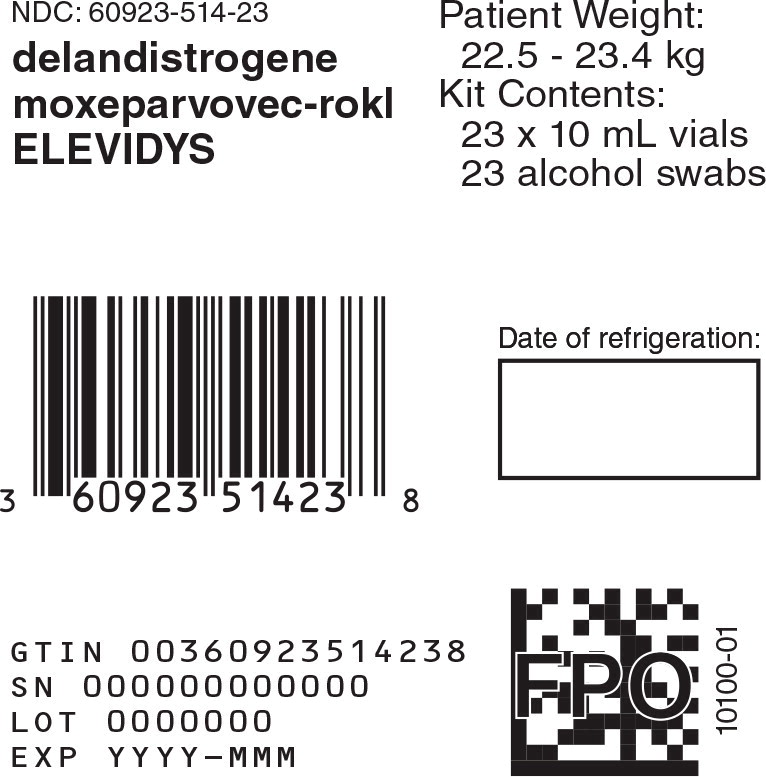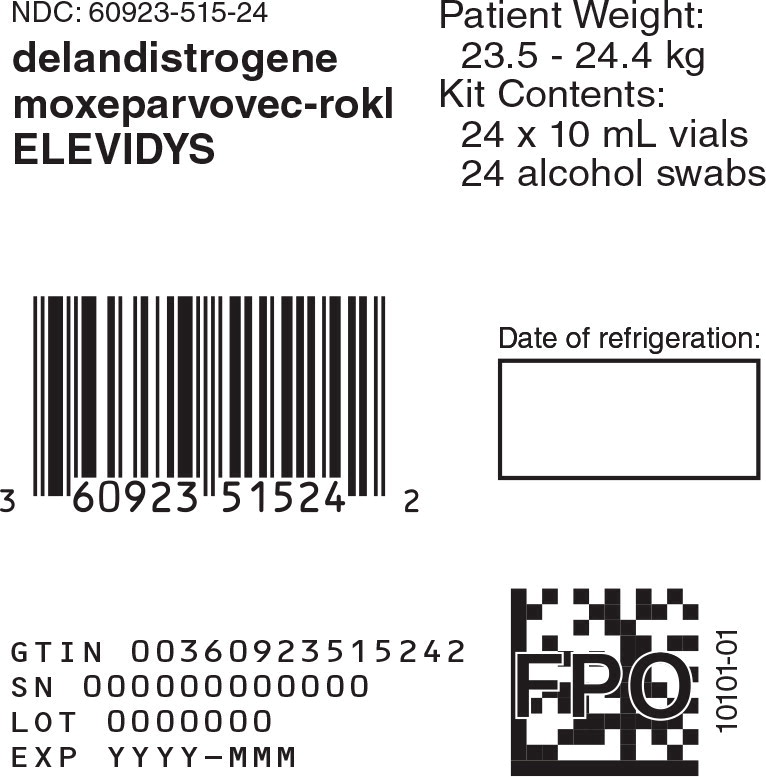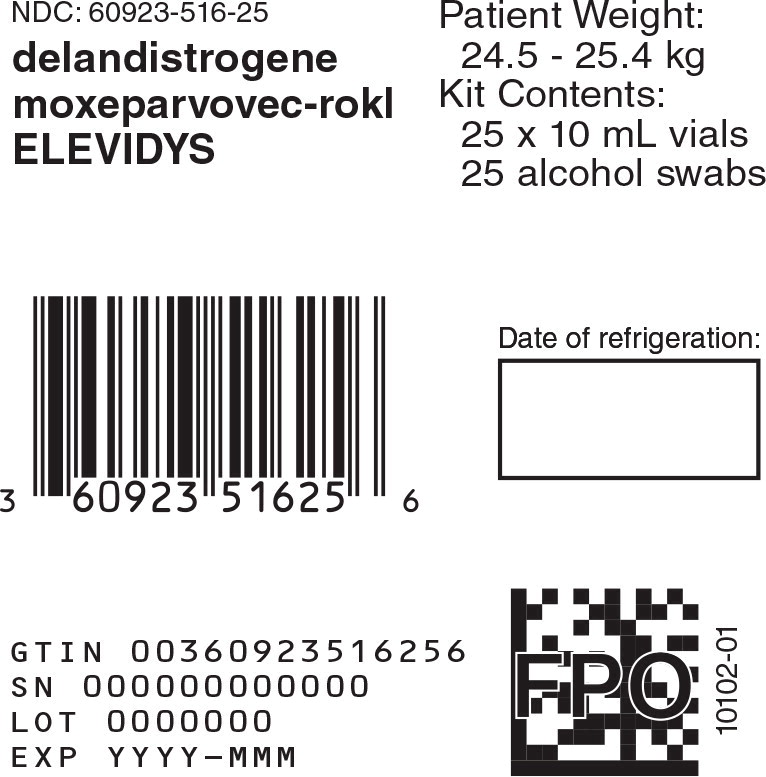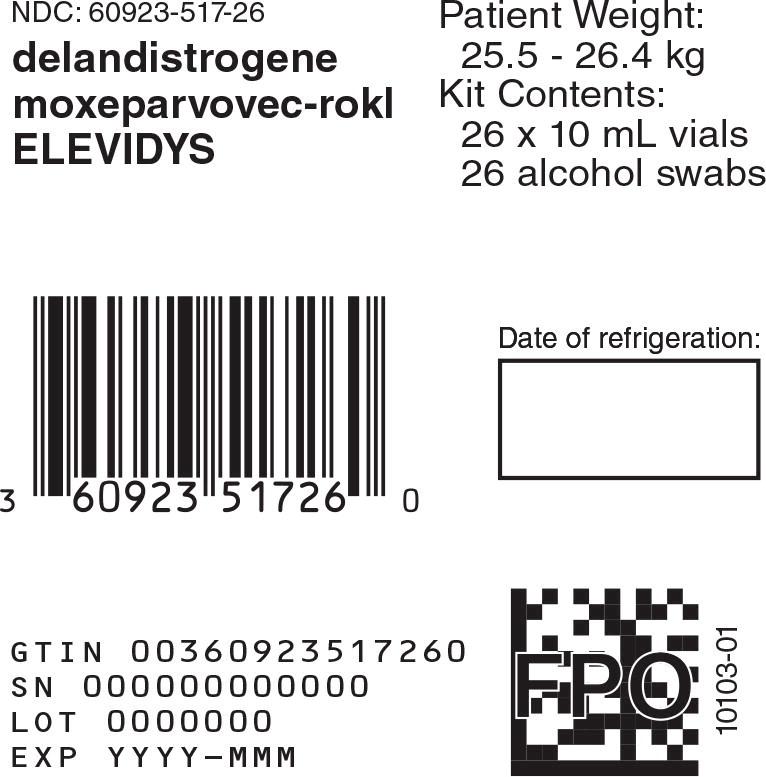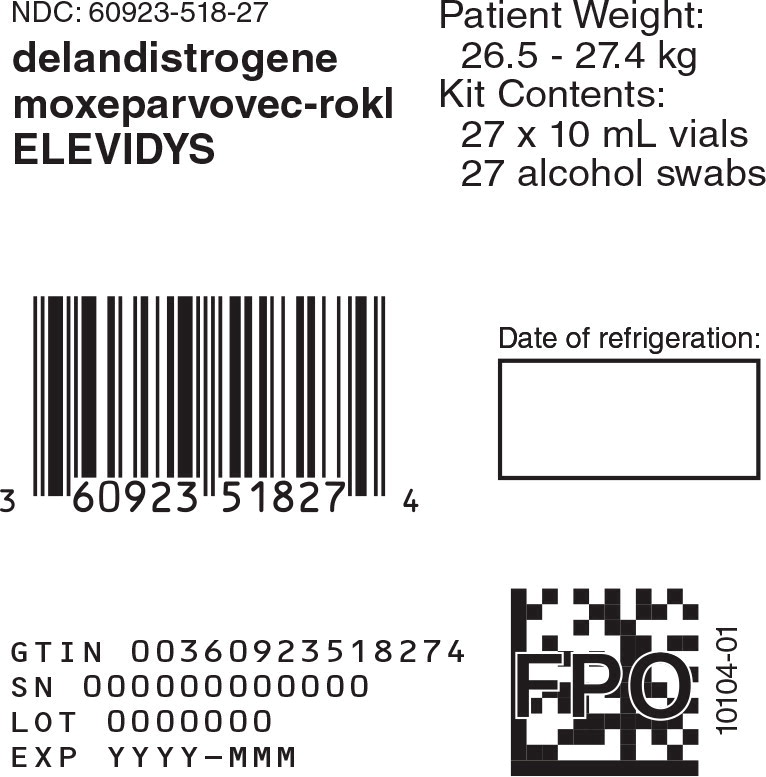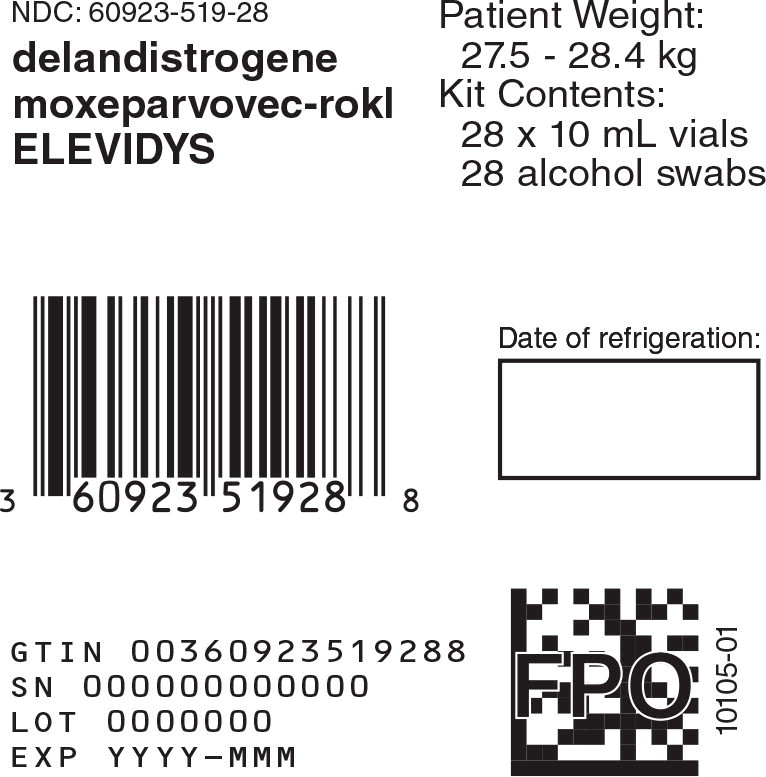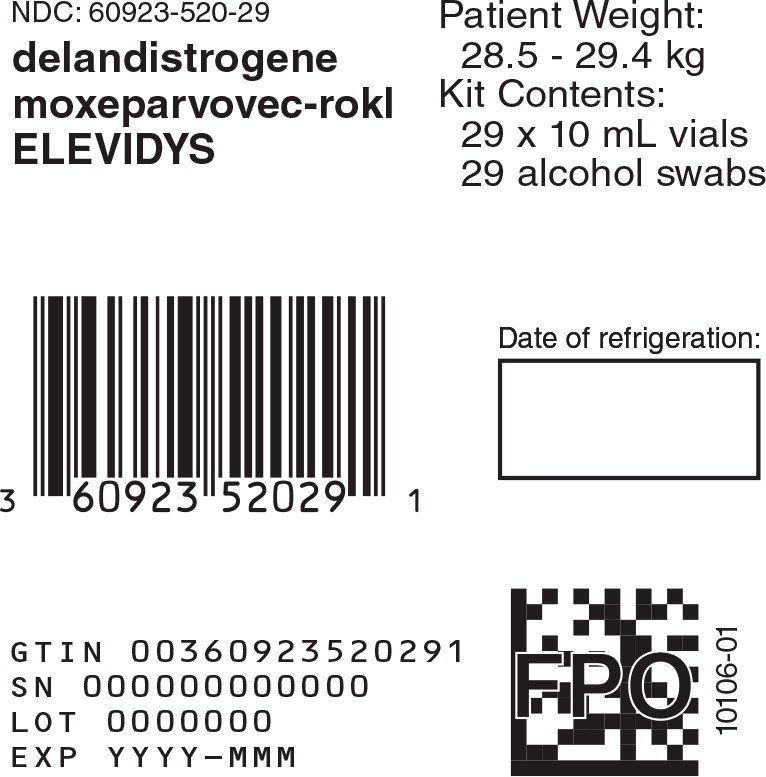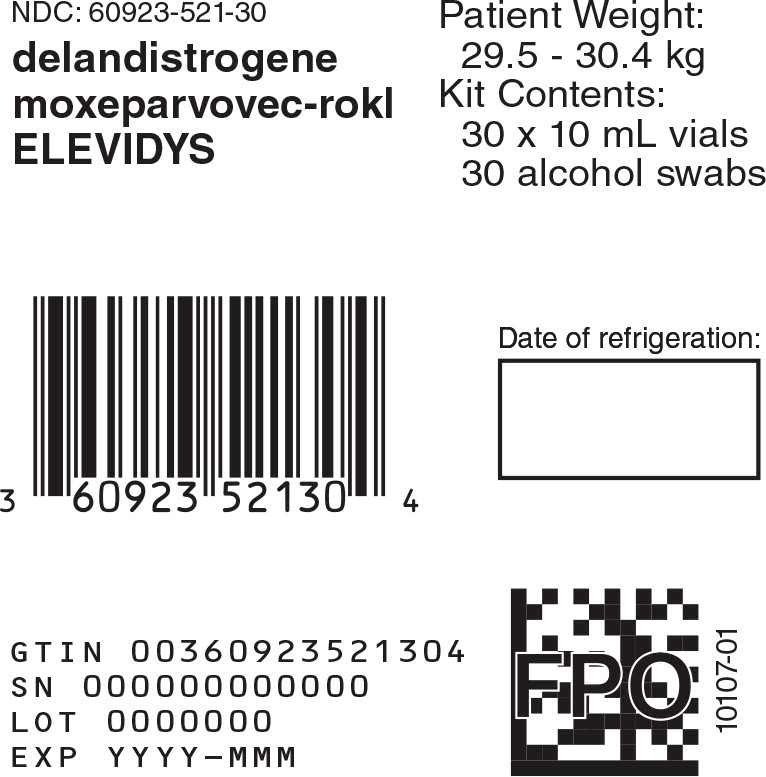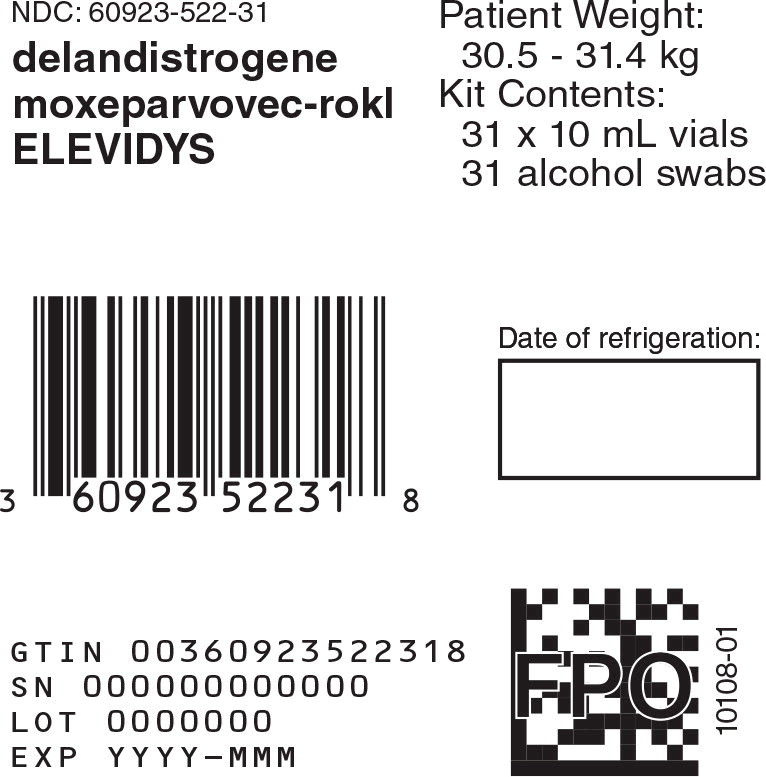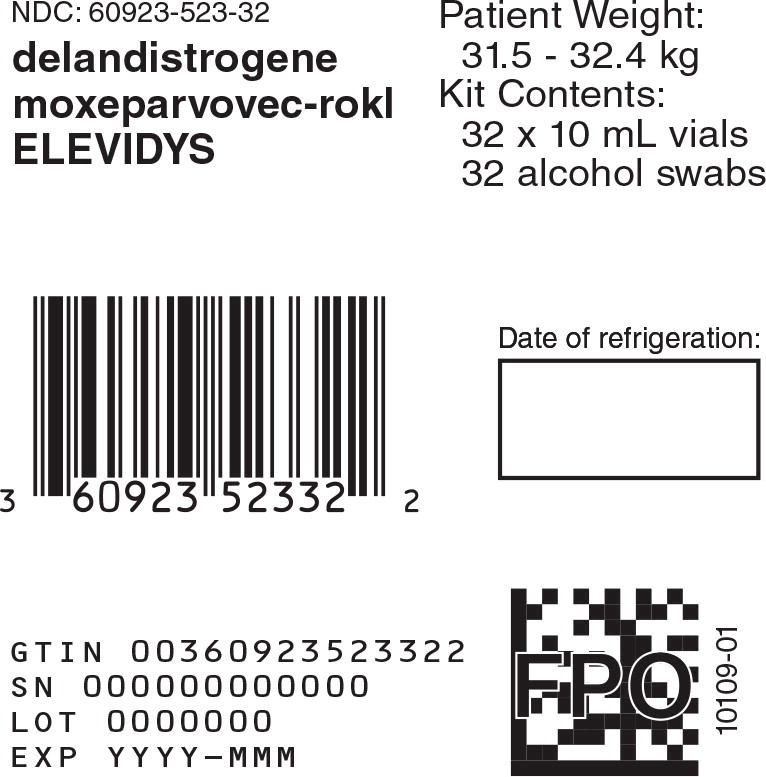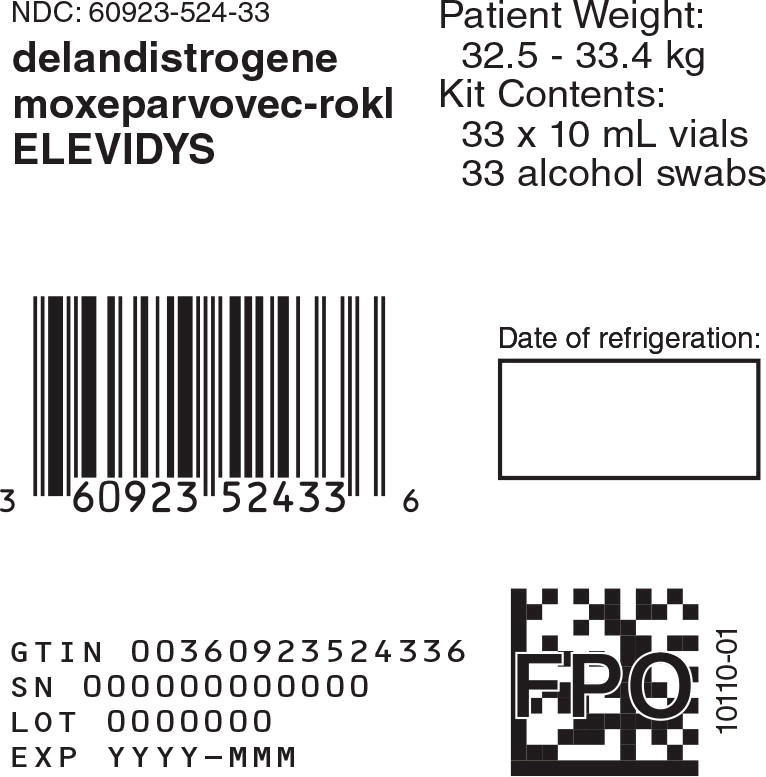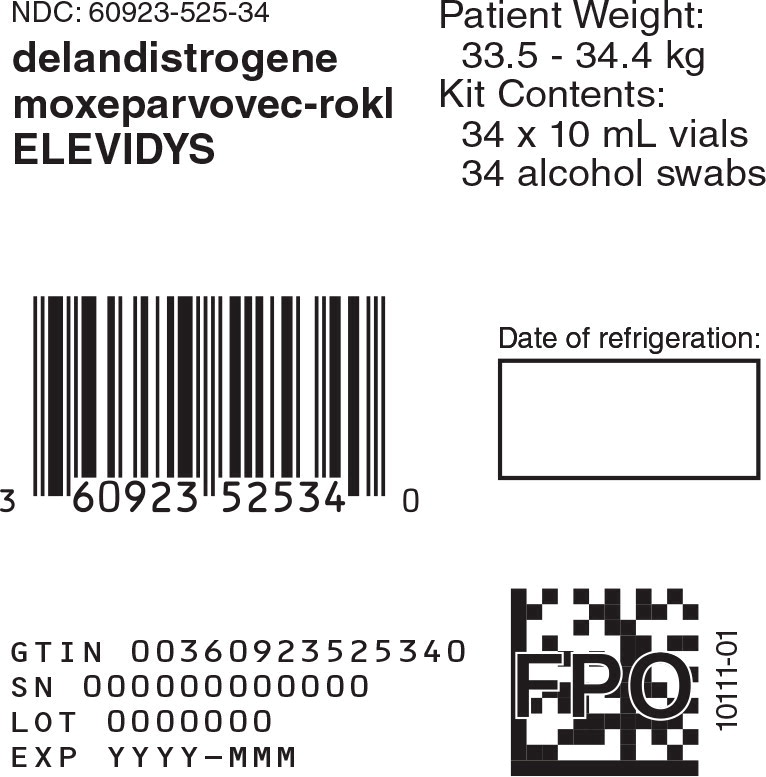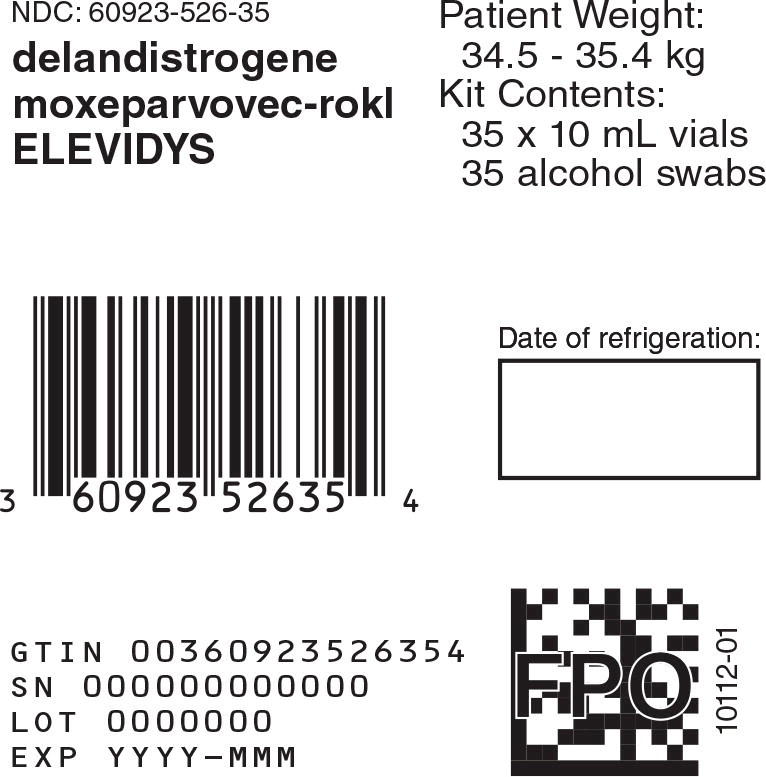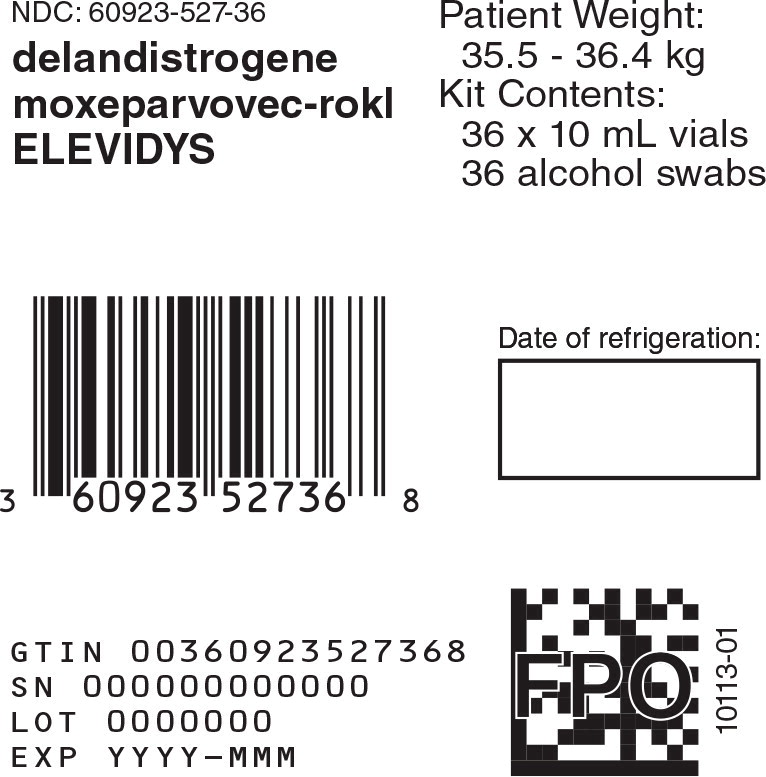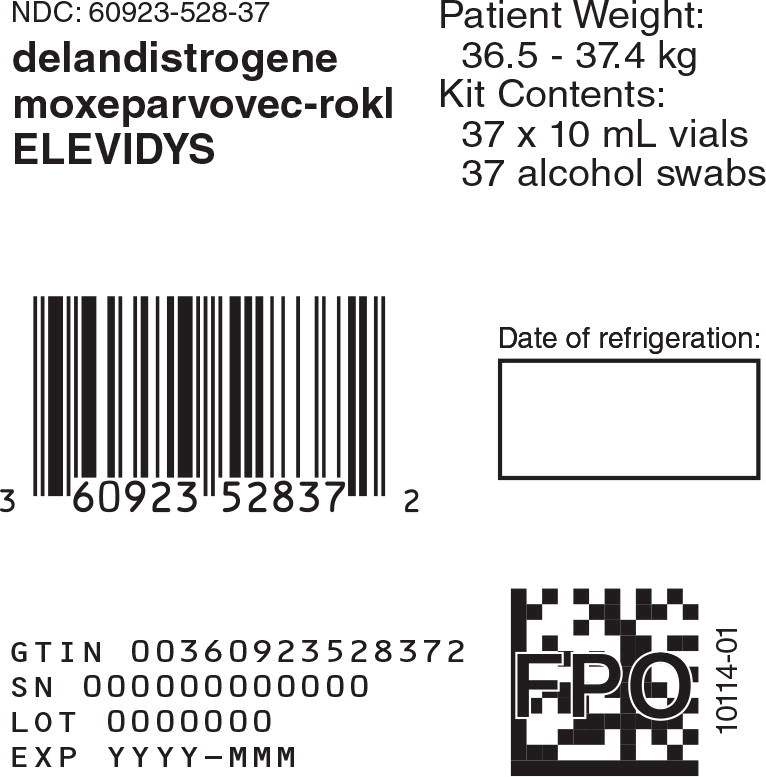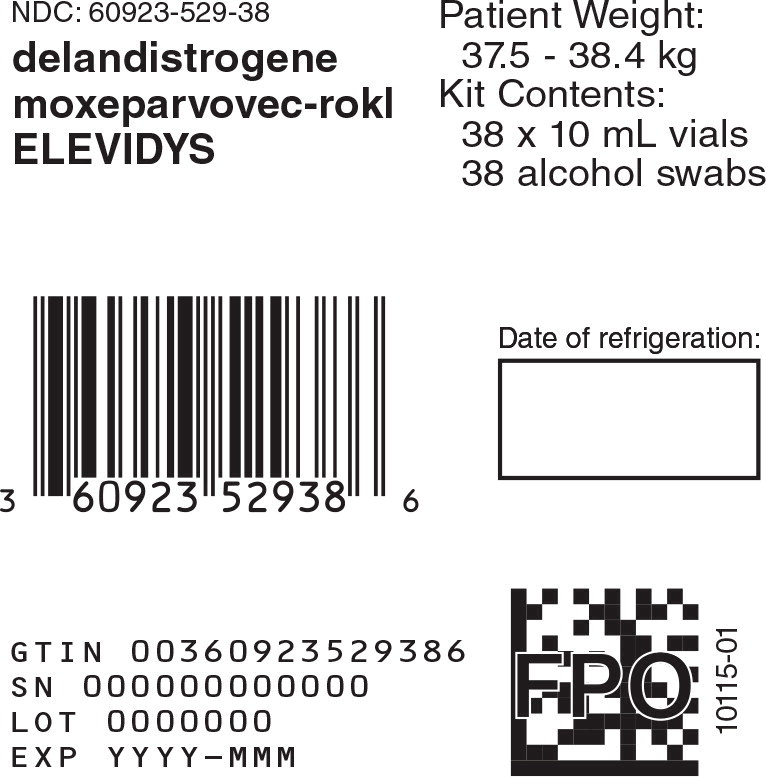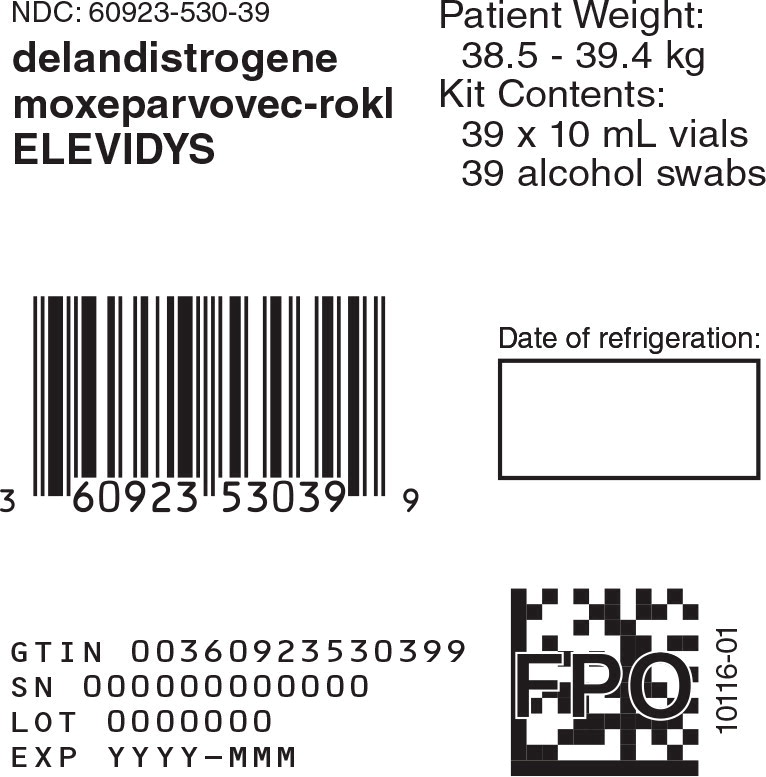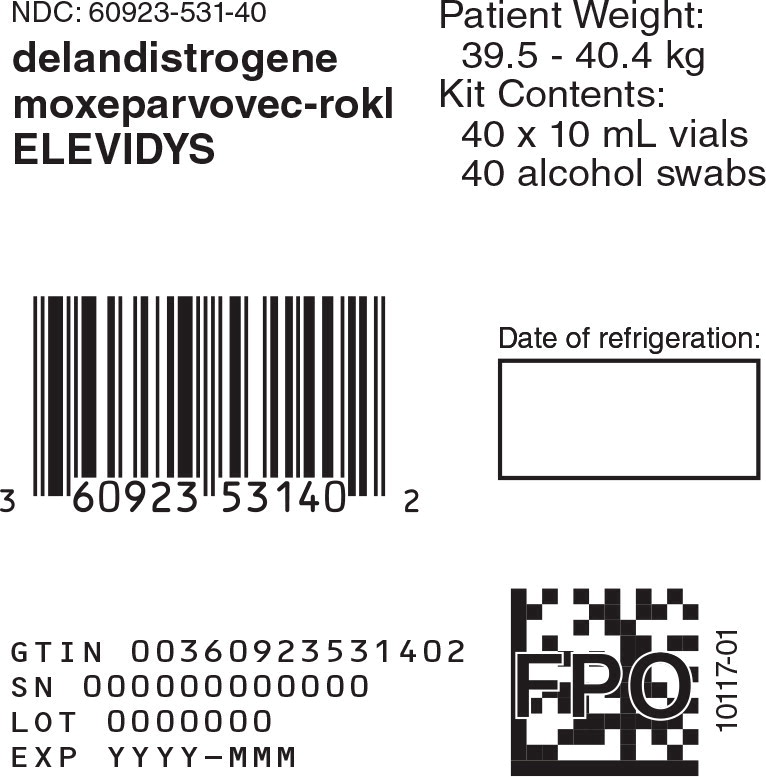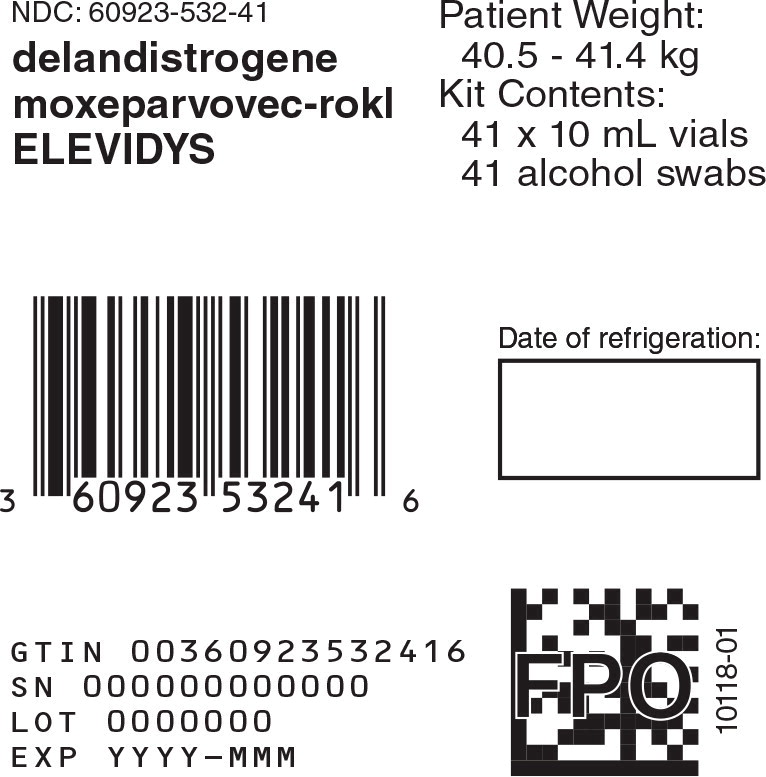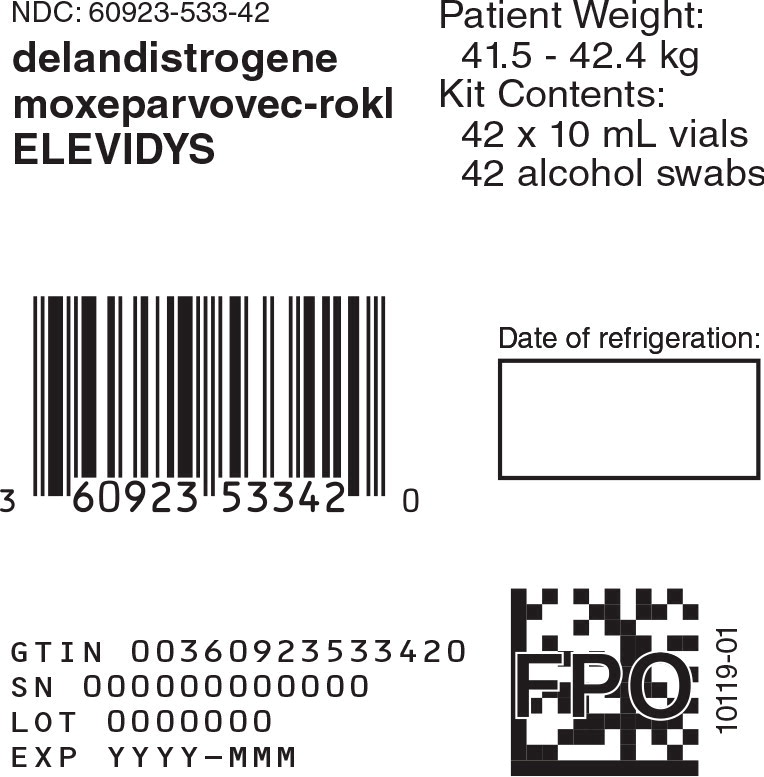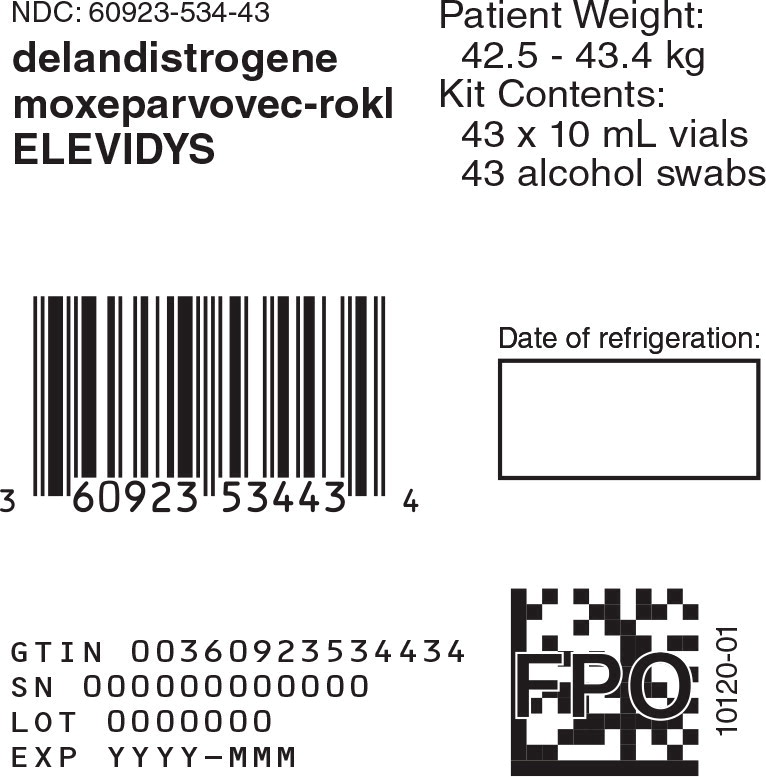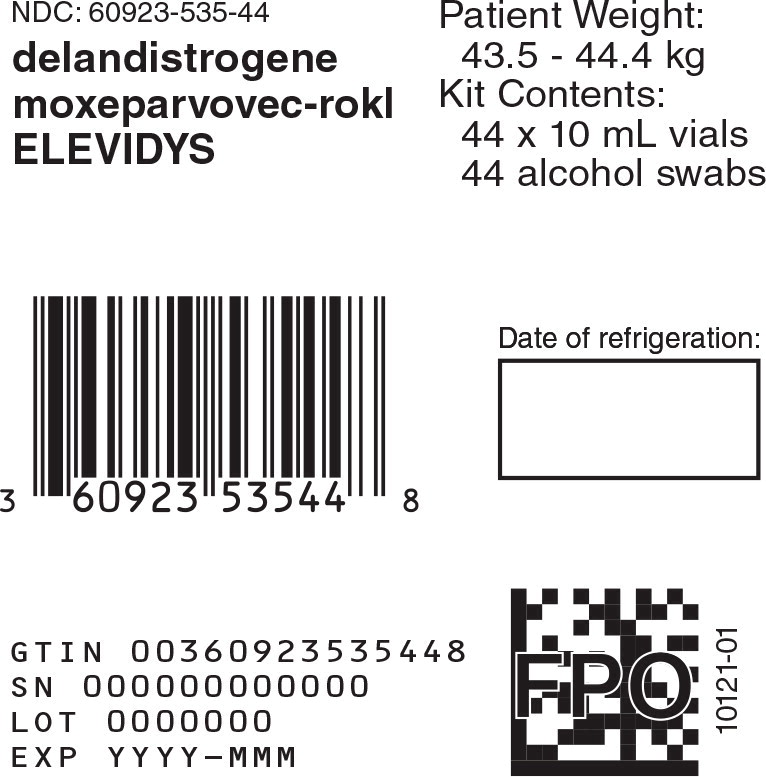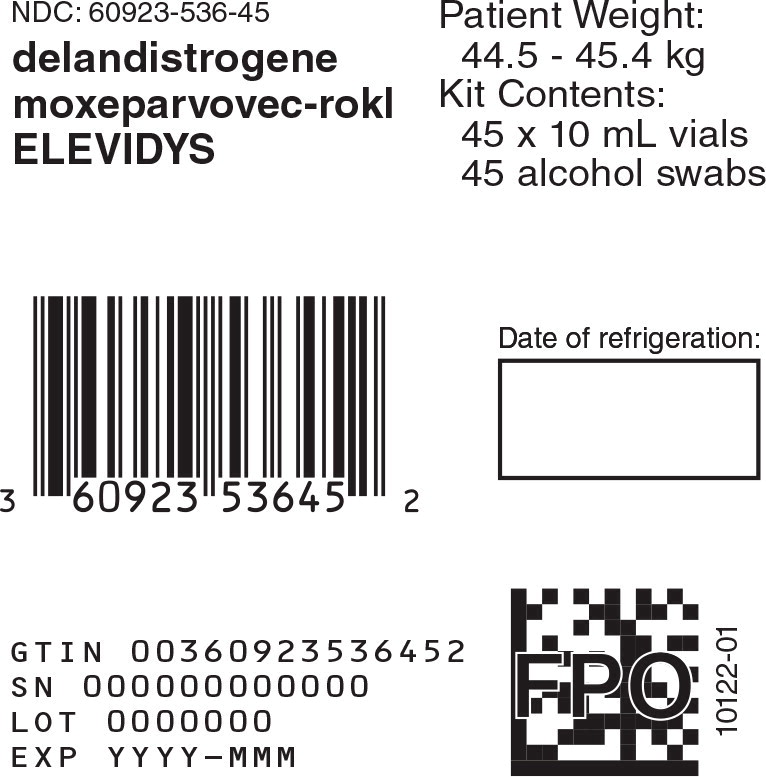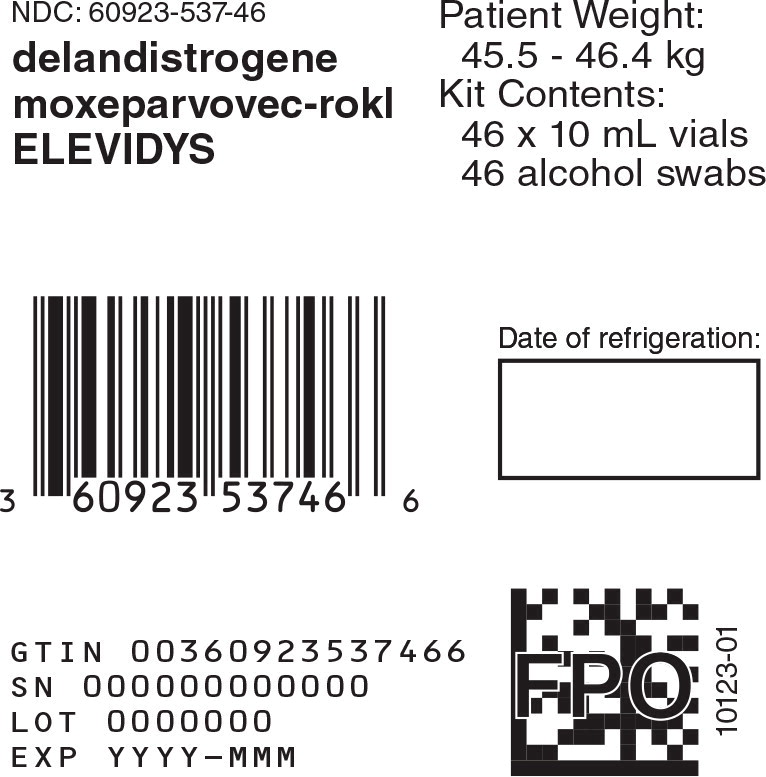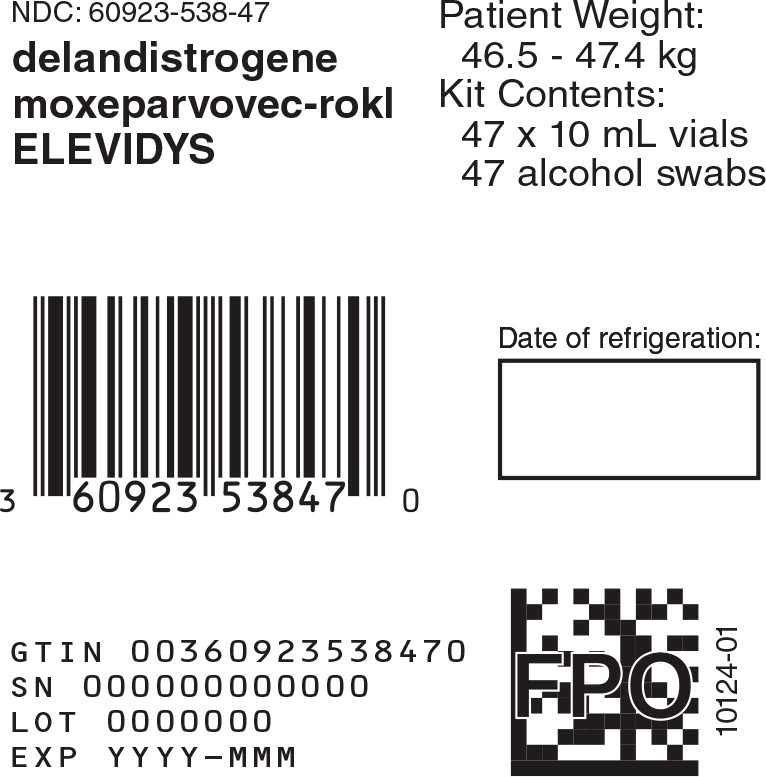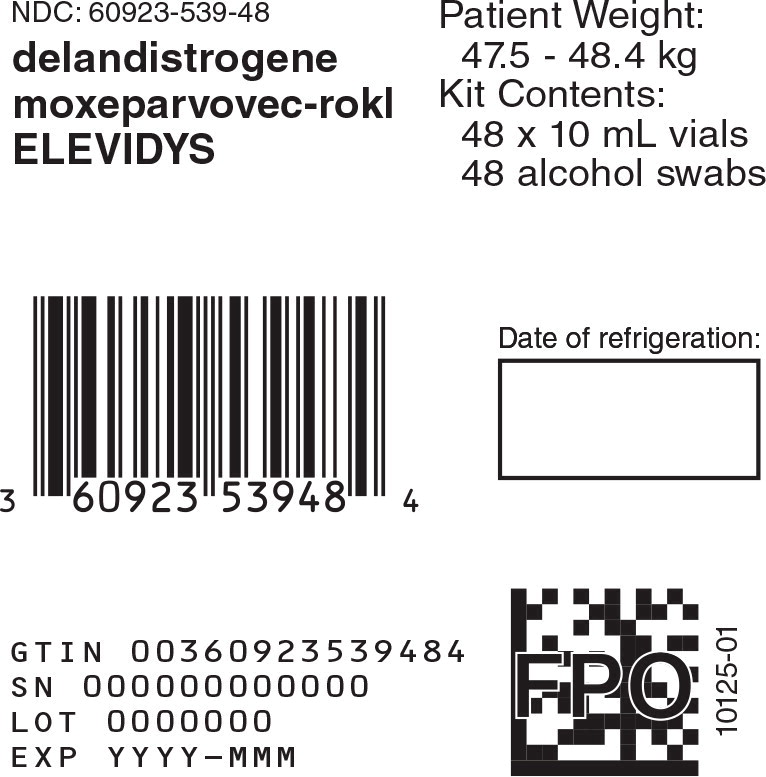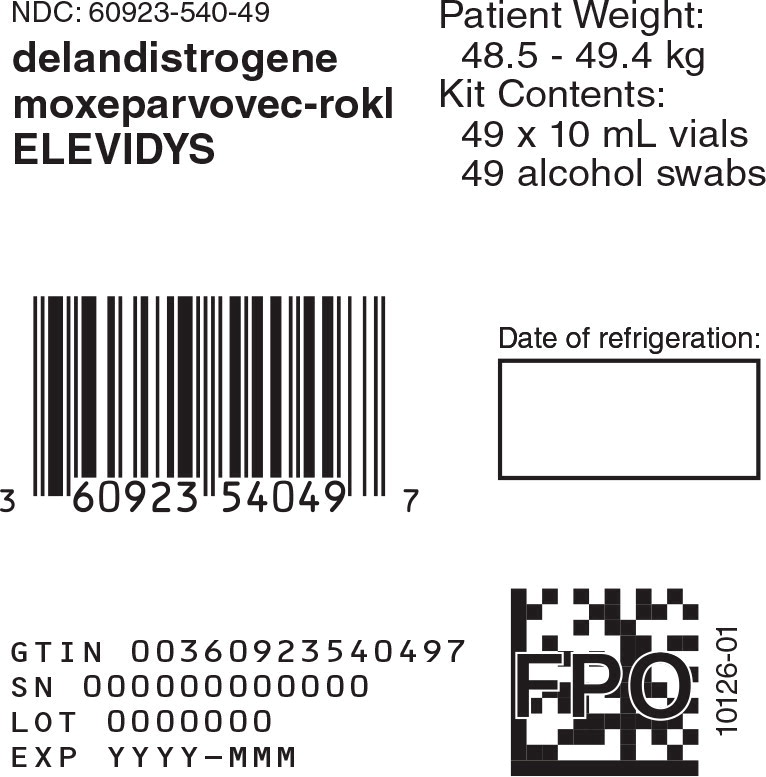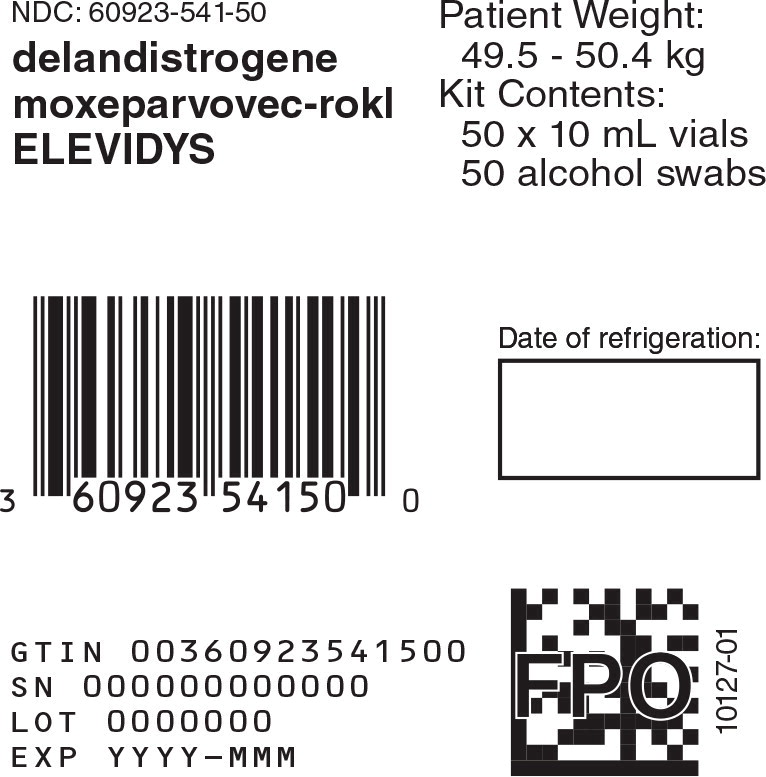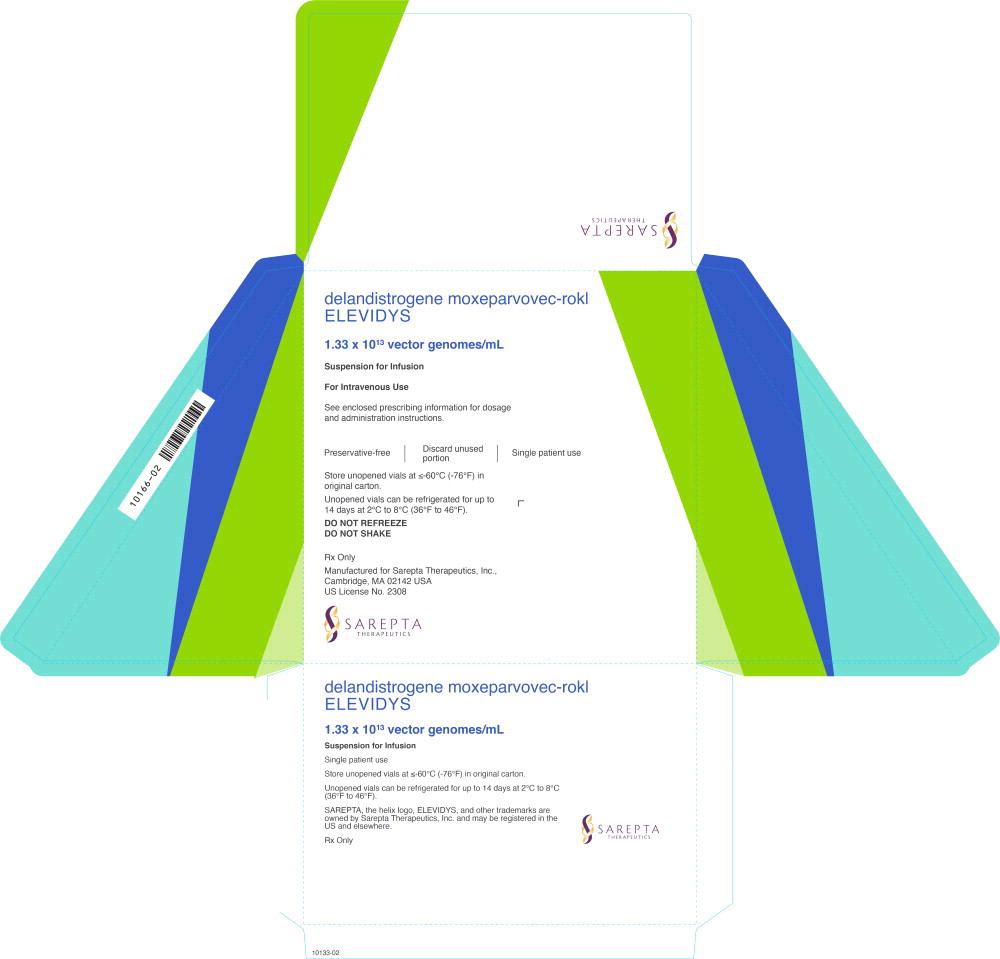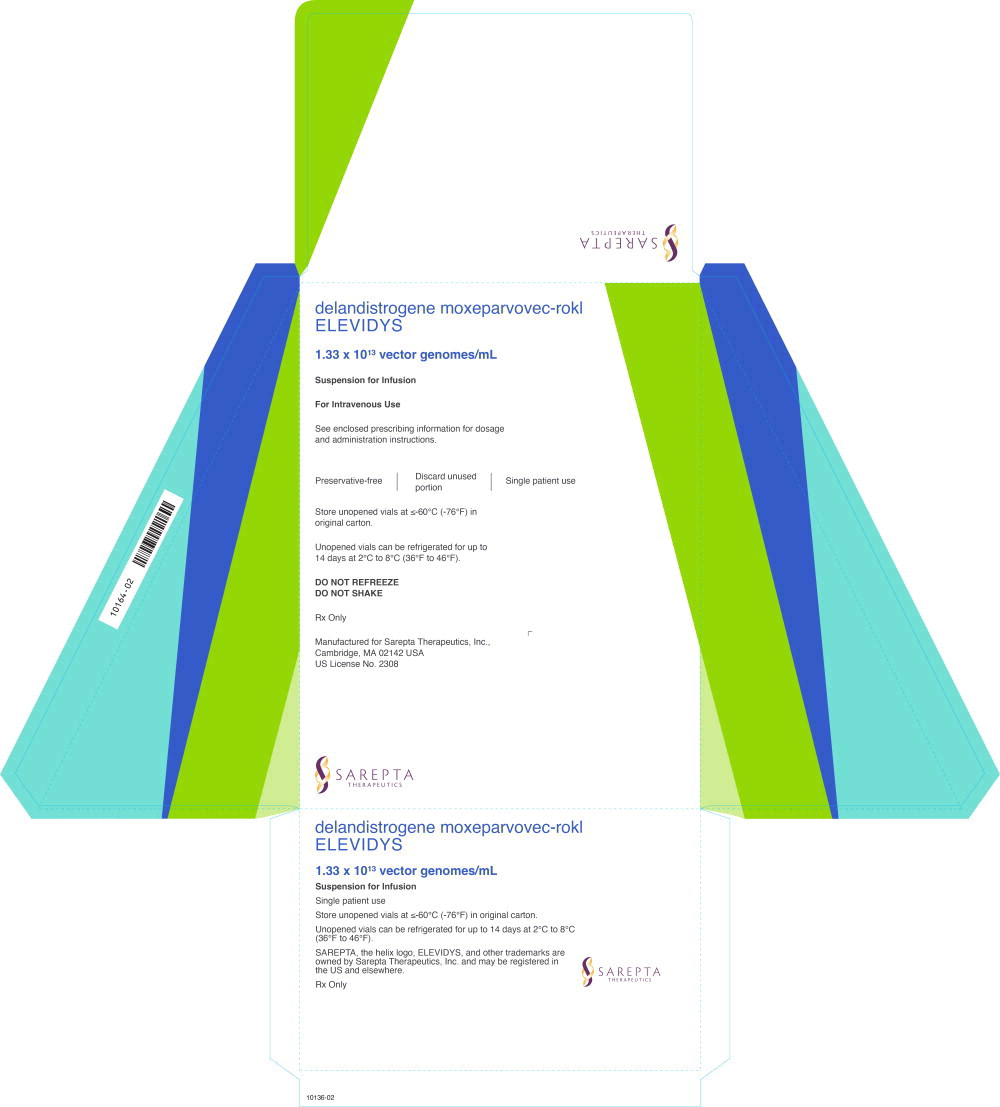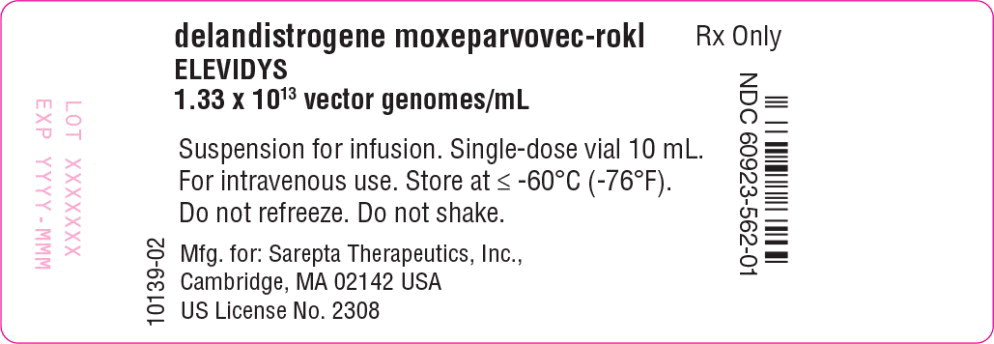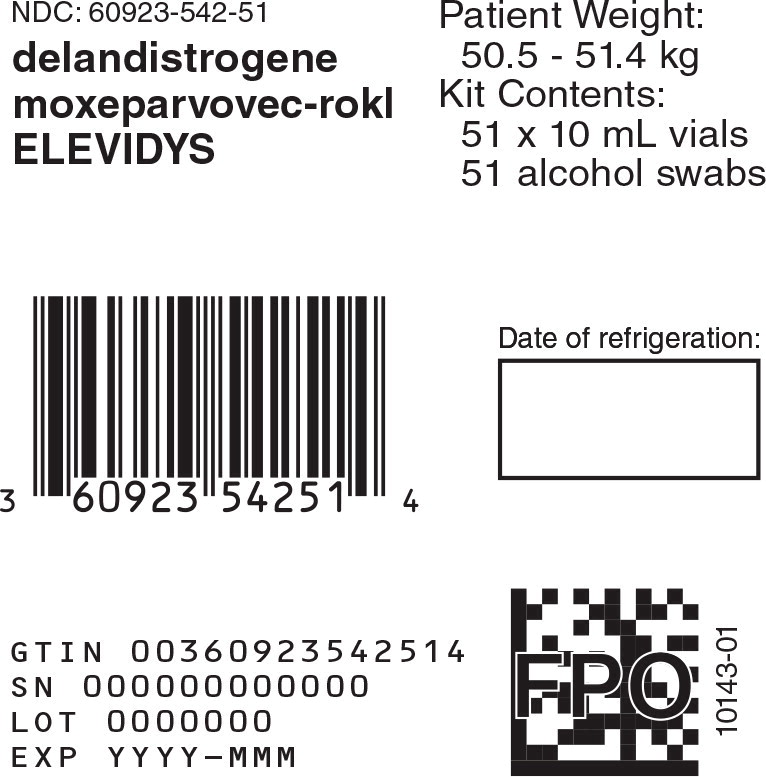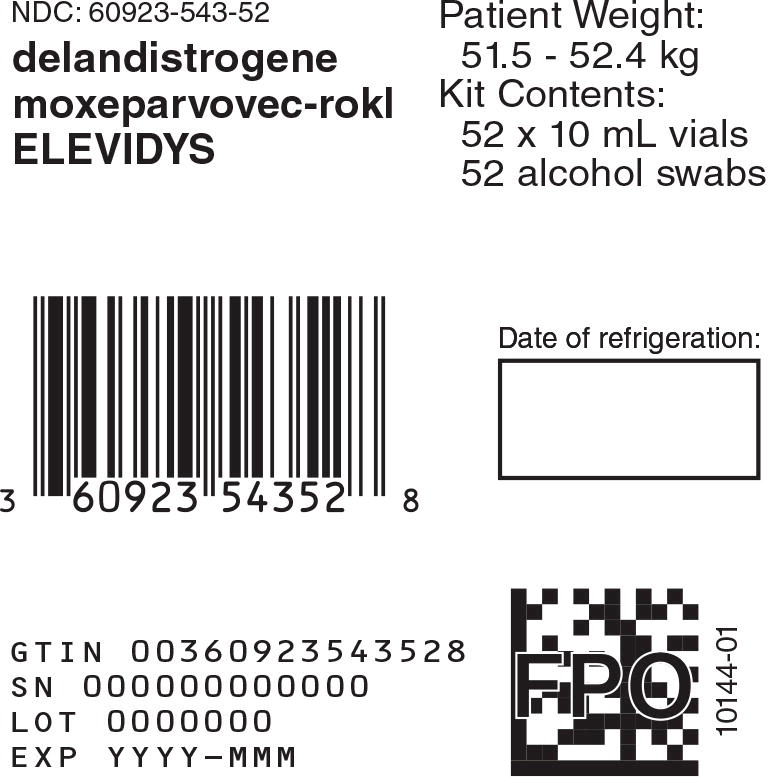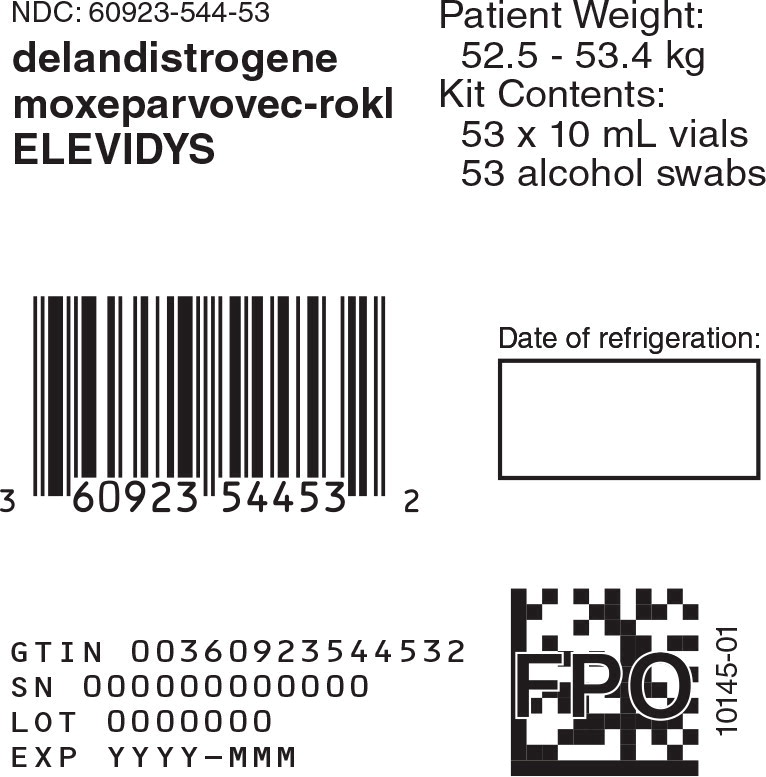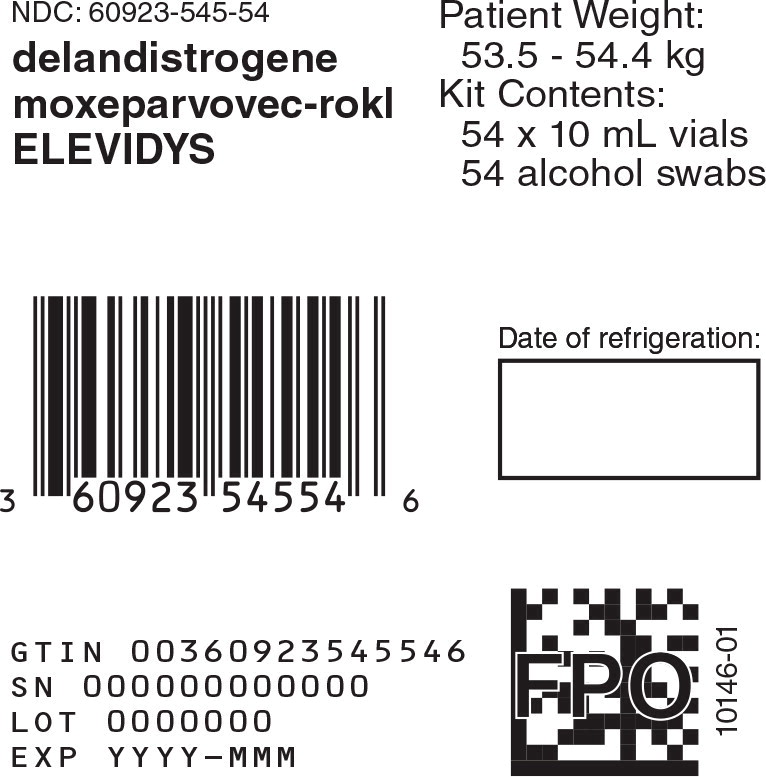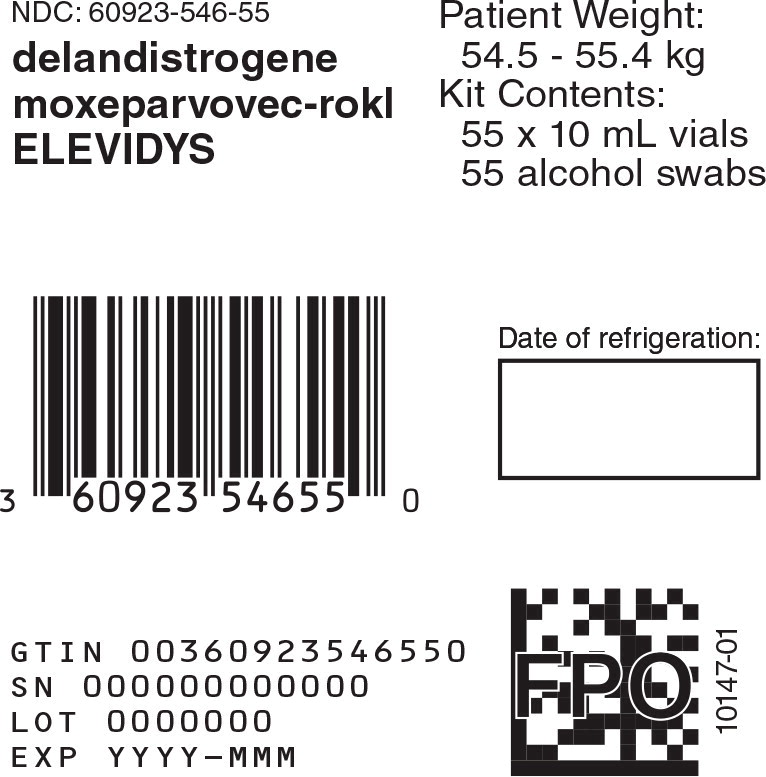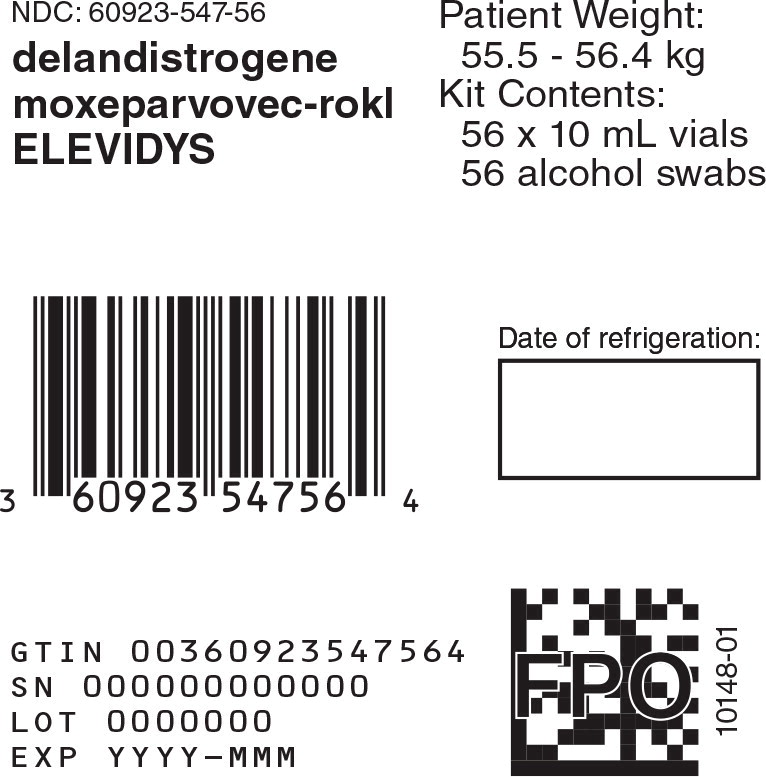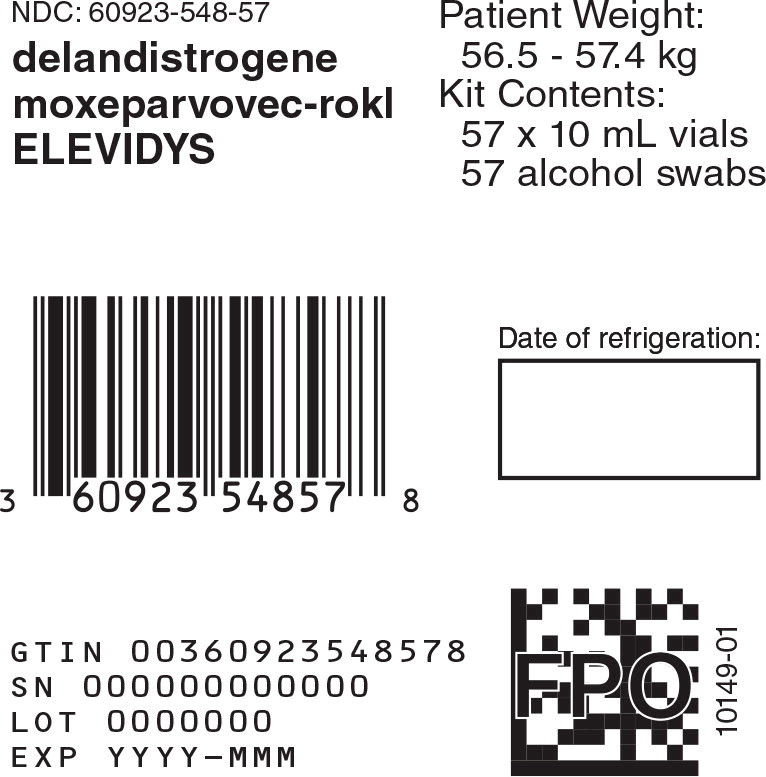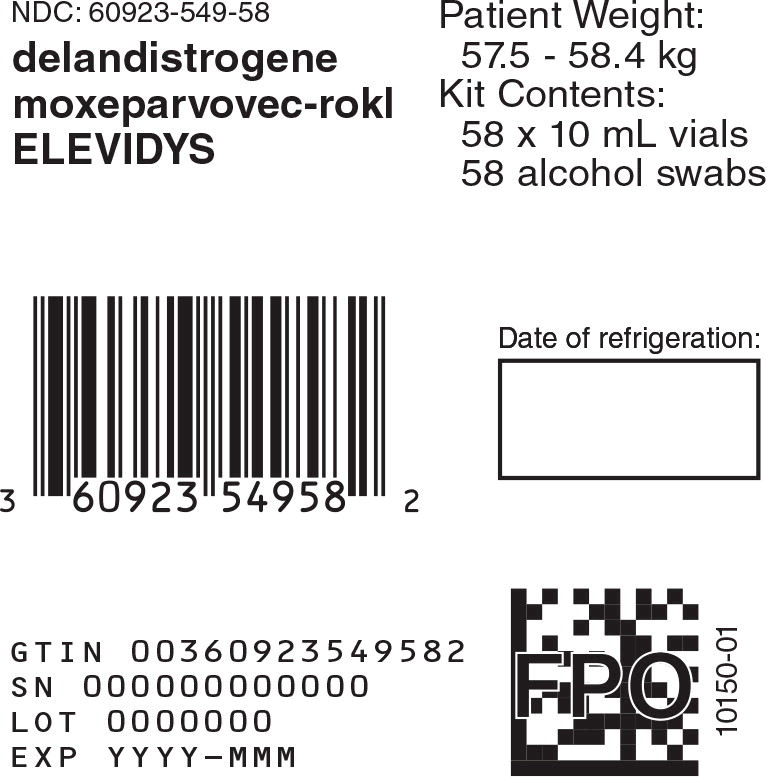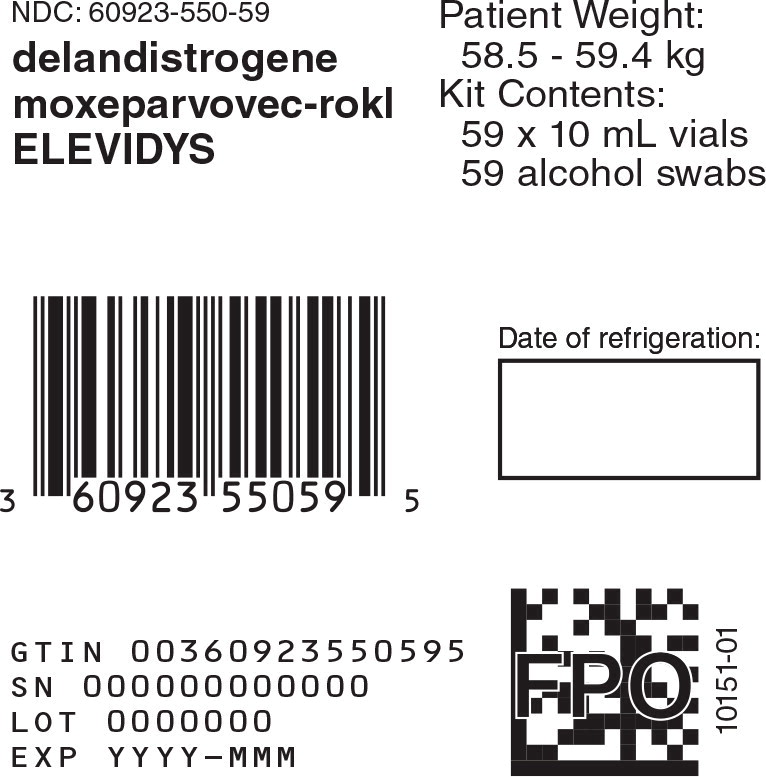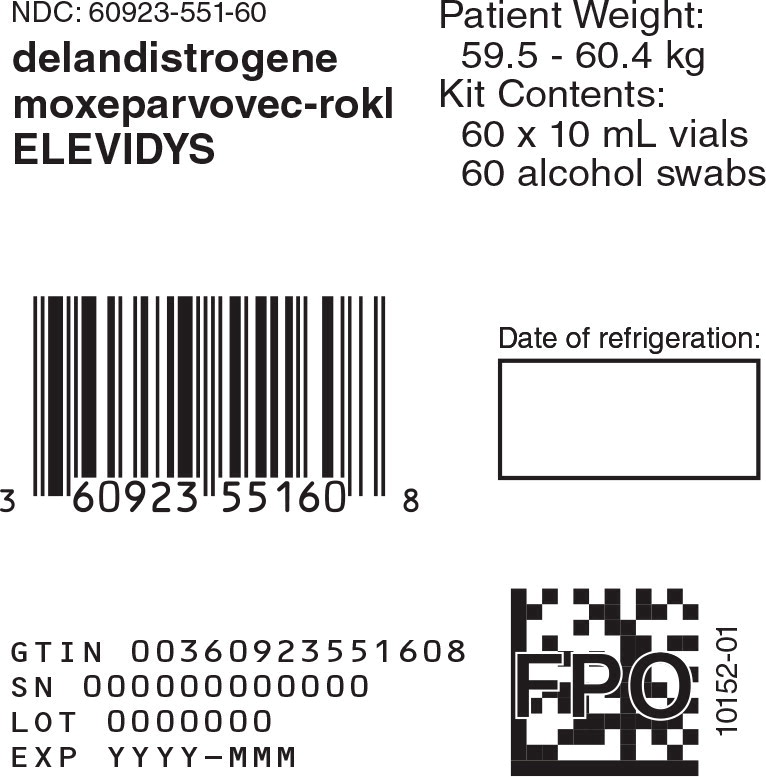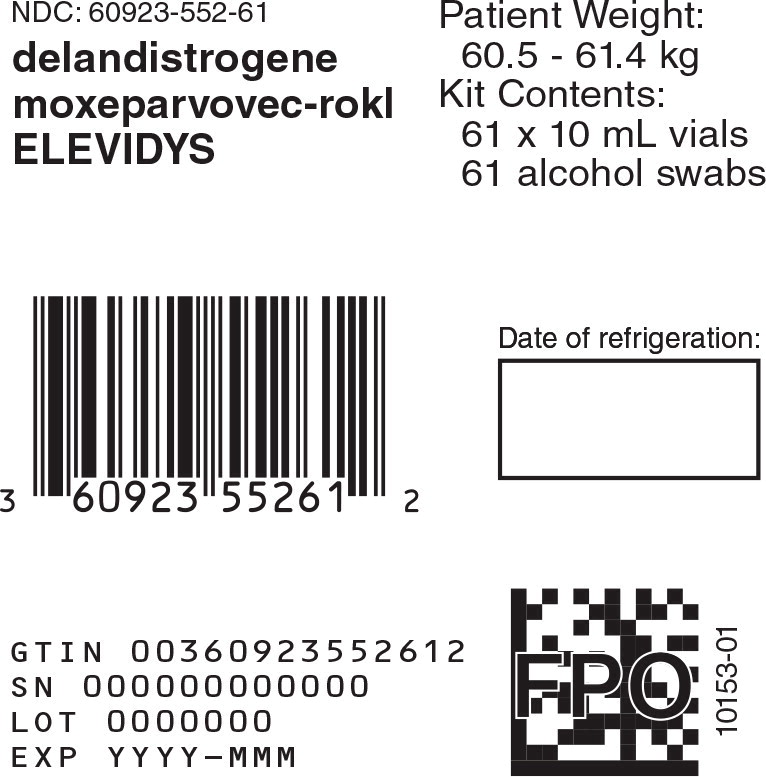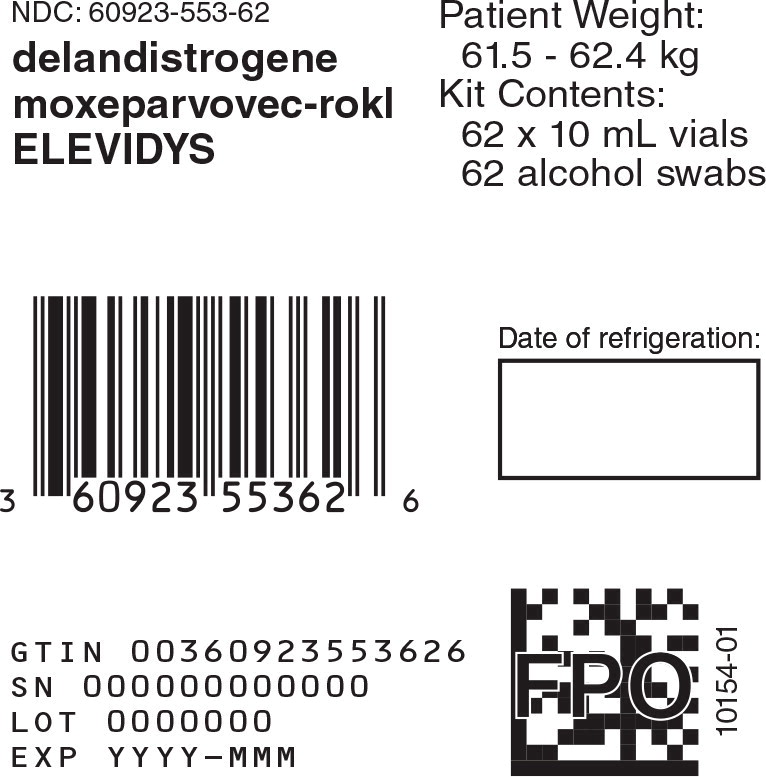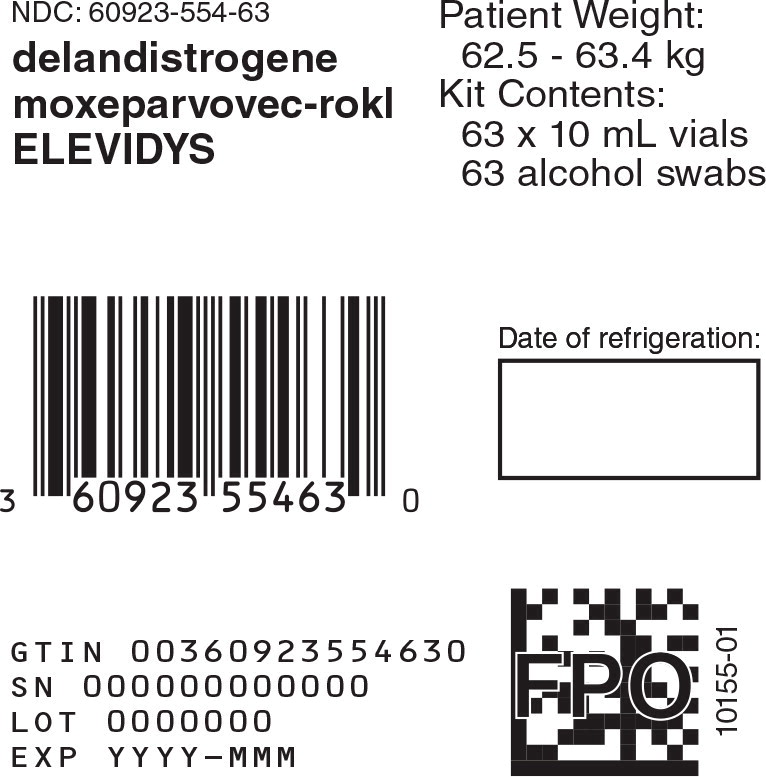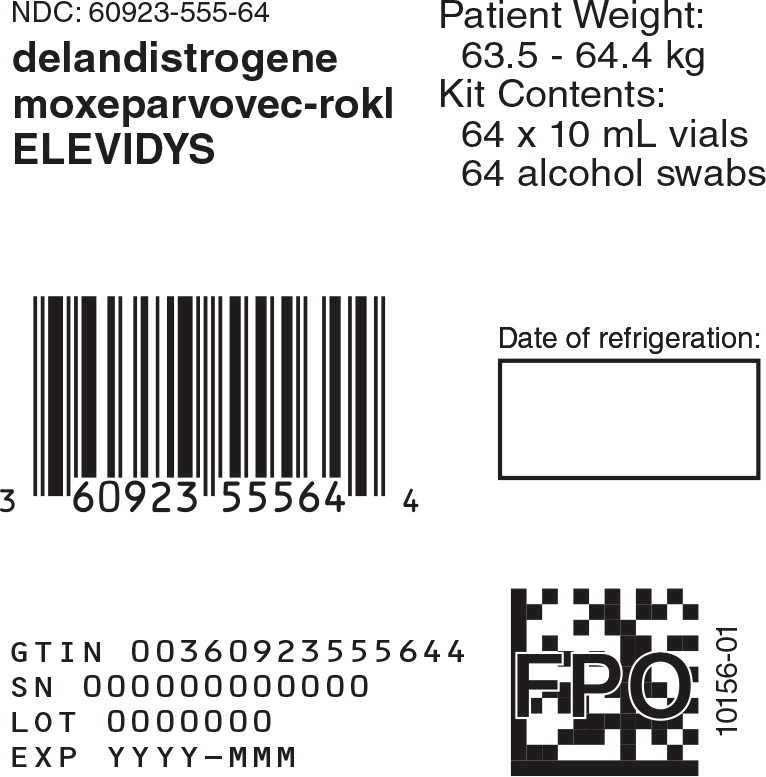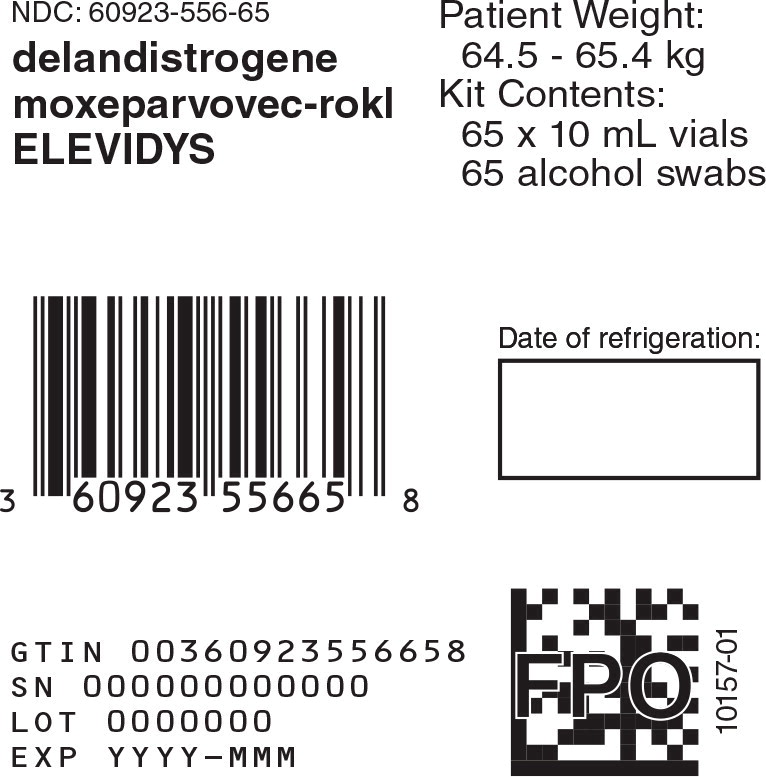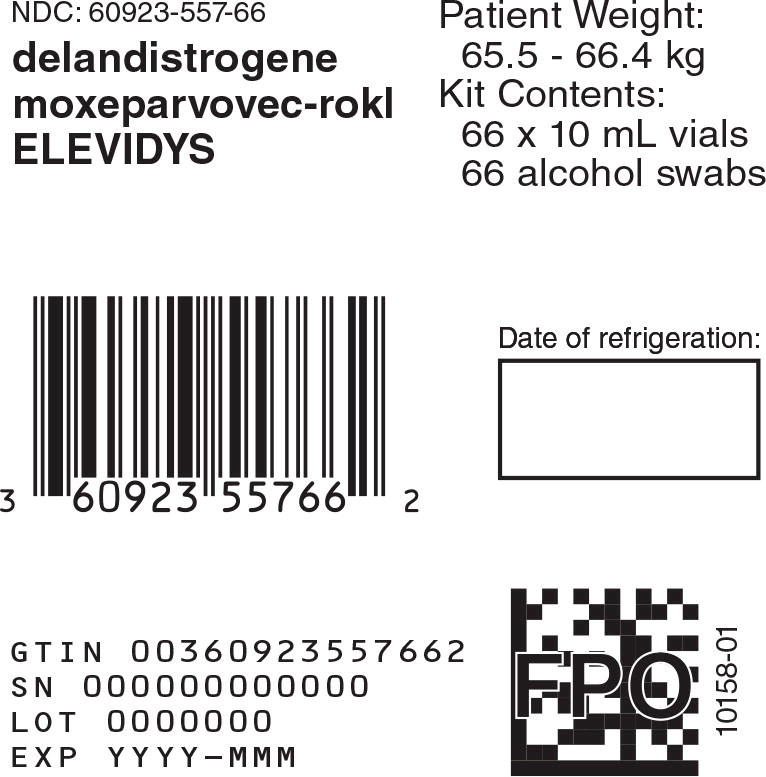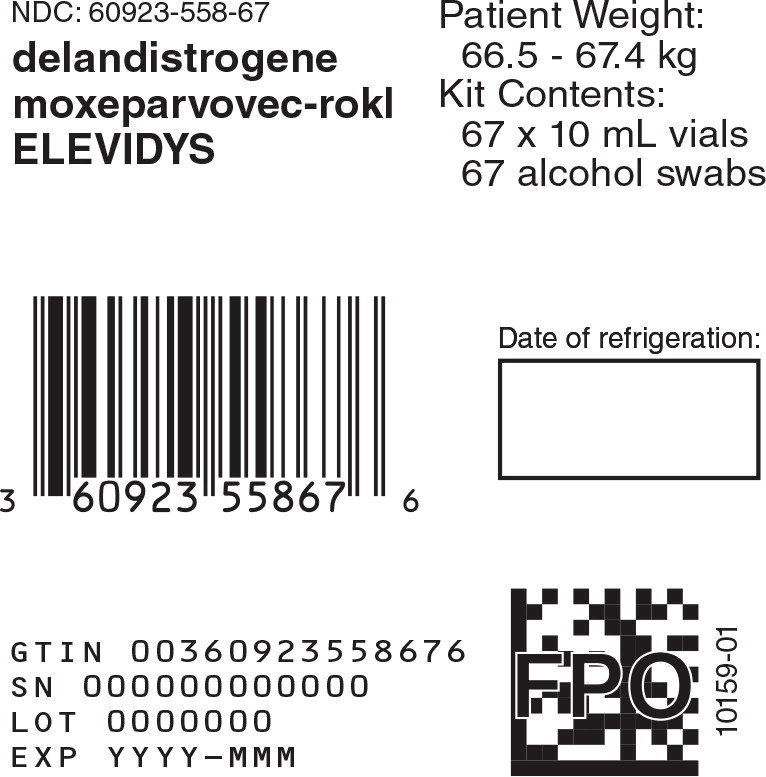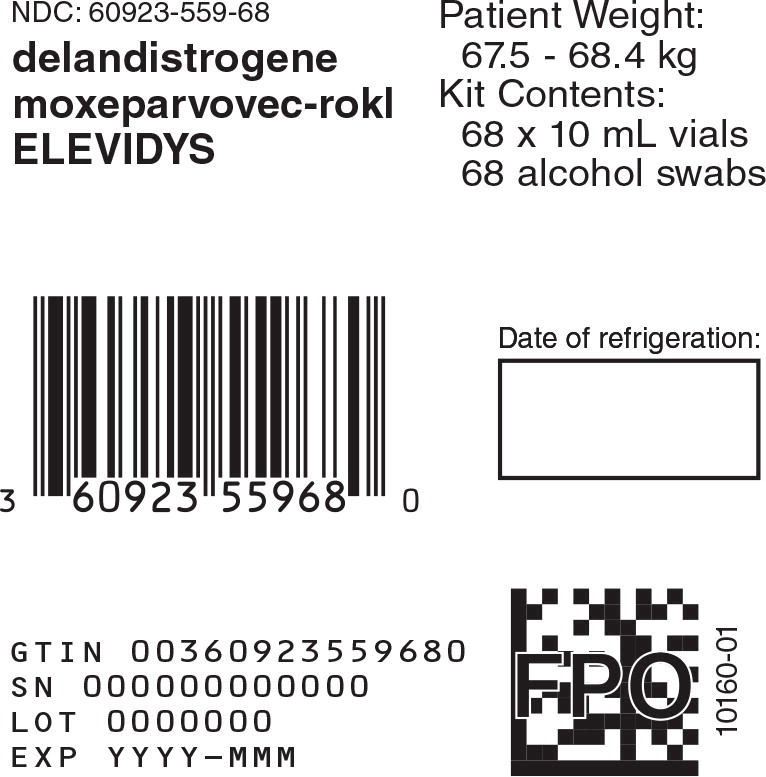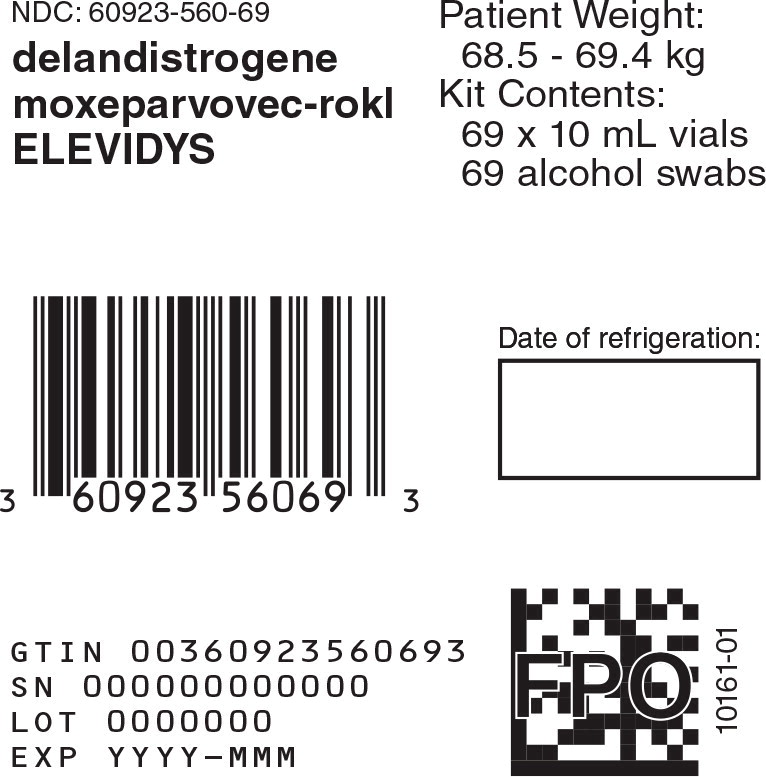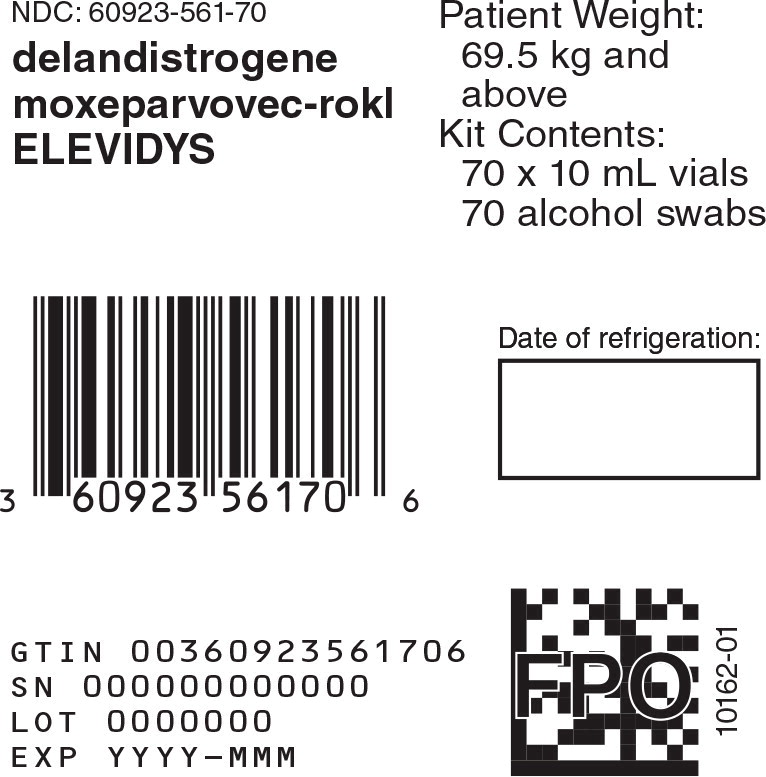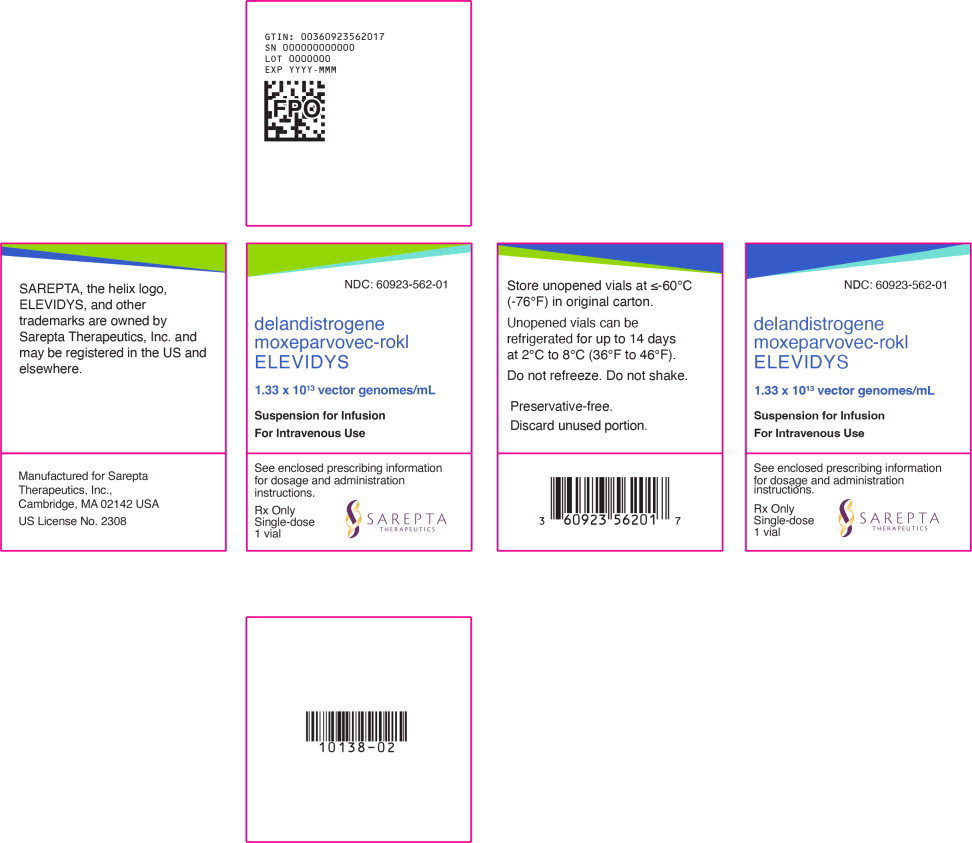 DRUG LABEL: ELEVIDYS
NDC: 60923-501 | Form: KIT | Route: INTRAVENOUS
Manufacturer: Sarepta Therapeutics, Inc.
Category: prescription | Type: HUMAN PRESCRIPTION DRUG LABEL
Date: 20251121

ACTIVE INGREDIENTS: delandistrogene moxeparvovec 13300000000000 {GC}/1 mL; Isopropyl Alcohol 0.75 g/1 1
INACTIVE INGREDIENTS: Sodium chloride; Tromethamine Hydrochloride; Tromethamine; Magnesium chloride; Poloxamer 188; Water

HIGHLIGHTS OF PRESCRIBING INFORMATION

These highlights do not include all the information needed to use ELEVIDYS® safely and effectively. See full prescribing information for ELEVIDYS.
ELEVIDYS (delandistrogene moxeparvovec-rokl) suspension, for intravenous infusion
Initial U.S. Approval: 2023

RECENT MAJOR CHANGES

Boxed Warning | 11/2025
Indication and Usage (1) | 11/2025
Dosage and Administration (2) | 11/2025
Contraindications (4) | 11/2025
Warnings and Precautions (5) | 11/2025

WARNING: ACUTE SERIOUS LIVER INJURY AND ACUTE LIVER FAILURE

See full prescribing information for complete boxed warning.

- Acute serious liver injury, including life-threatening and fatal acute liver failure, has occurred with ELEVIDYS. (5.1)
- Patients with preexisting liver impairment may be at higher risk. (5.1)
- Prior to infusion, assess liver function by clinical examination and laboratory testing. Administer systemic corticosteroids before and after ELEVIDYS infusion. Continue to monitor liver function weekly for the first 3 months after infusion and continue until results are unremarkable. (2.1, 2.2, 2.4)
- Instruct patients to maintain proximity to an appropriate healthcare facility, as determined by the healthcare provider, for at least 2 months following ELEVIDYS infusion. (2.1)
- Obtain prompt consultation with a specialist (e.g., gastroenterologist or hepatologist) if acute serious liver injury or impending acute liver failure is suspected. (2.2, 5.1)

1 INDICATIONS AND USAGE

ELEVIDYS is an adeno-associated virus vector-based gene therapy indicated for the treatment of patients 4 years of age and older with Duchenne muscular dystrophy (DMD) who are ambulatory and have a confirmed mutation in the DMD gene. (1,12.2,14)

Limitations of Use:

ELEVIDYS is not recommended in patients with:

- Preexisting liver impairment (defined as gamma-glutamyl transferase [GGT] > 2 x upper limit of normal or total bilirubin > the upper limit of normal not due to Gilbert's syndrome) or active hepatic viral infection due to the high risk of acute serious liver injury and acute liver failure.
- Recent vaccination (within 4 weeks of treatment) due to immunogenicity and potential safety concerns.
- Active or recent (within 4 weeks) infections due to safety concerns.

2 DOSAGE AND ADMINISTRATION

ELEVIDYS is for single-dose intravenous infusion only.

- Select patients for treatment with ELEVIDYS with anti-AAVrh74 total binding antibody titers <1:400. (2.1)
- Postpone in patients with active or recent (within 4 weeks) infections. (2.1)
- Assess liver function, platelet counts and troponin-I before ELEVIDYS infusion. (2.1)
- Recommended dosage: 10 to 70 kg: 1.33 × 10^14 vector genomes (vg) per kg of body weight; 70 kg or greater: 9.31 × 10^15 vg. (2.2)
- One day prior to infusion, initiate a corticosteroid regimen for a minimum of 60 days. Recommend modifying corticosteroid dose for patients with liver function abnormalities. (2.2)
- Administer as an intravenous infusion over 1-2 hours. Infuse at a rate of less than 10 mL/kg/hour. (2.4)

3 DOSAGE FORMS AND STRENGTHS

- ELEVIDYS is a suspension for intravenous infusion with a nominal concentration of 1.33 × 10^13 vg/mL. (3)
- ELEVIDYS is provided in a customized kit containing ten to seventy 10 mL single-dose vials, with each kit constituting a dosage unit based on the patient's body weight. (3)

4 CONTRAINDICATIONS

- ELEVIDYS is contraindicated in patients with any deletion in exon 8 and/or exon 9, including a deletion of any portion or the entirety of these exons, in the DMD gene. (4)

5 WARNINGS AND PRECAUTIONS

- Serious Infections: Serious infections with fatal outcomes may occur due to concomitant administration of corticosteroids, additional immunosuppressants, and ELEVIDYS. Monitor patients for signs and symptoms of infection; treat appropriately. (5.2)
- Myocarditis: Acute, serious, life-threatening myocarditis and troponin-I elevations have been observed. Monitor troponin-I before ELEVIDYS infusion, and weekly for the first month after ELEVIDYS infusion. (5.3)
- Infusion-related Reactions: Infusion-related reactions, including hypersensitivity reactions and anaphylaxis, have occurred. Monitor during administration and for at least 3 hours after end of infusion. If symptoms occur, slow or stop the infusion and give appropriate treatment. Once symptoms resolve, restart infusion at a slower infusion rate. Discontinue infusion for anaphylaxis. (2.4, 5.4)
- Immune-mediated Myositis: Severe to life-threatening immune-mediated myositis has been reported with ELEVIDYS in patients with deletions including portions of exons 1 to 17 and /or exons 59 to 71 of the DMD gene. Consider additional immunomodulatory treatment if symptoms of myositis occur (e.g., unexplained increased muscle pain, tenderness, or weakness). (5.5)
- Pre-existing Immunity against AAVrh74: Perform baseline testing for presence of anti-AAVrh74 total binding antibodies prior to ELEVIDYS administration. (5.6)

6 ADVERSE REACTIONS

Most common adverse reactions (incidence ≥5%) were vomiting and nausea, liver injury, pyrexia, thrombocytopenia, and troponin-I increased. (6.1)

To report SUSPECTED ADVERSE REACTIONS, contact Sarepta Therapeutics, Inc., at 1-888-SAREPTA (1-888-727-3782) or FDA at 1-800-FDA-1088 or www.fda.gov/medwatch.

FULL PRESCRIBING INFORMATION

WARNING: ACUTE SERIOUS LIVER INJURY AND ACUTE LIVER FAILURE

- Acute serious liver injury, including life-threatening and fatal acute liver failure, has occurred with ELEVIDYS [see Warnings and Precautions (5.1)].
- Patients with preexisting liver impairment may be at higher risk [see Warnings and Precautions (5.1)].
- Prior to infusion, assess liver function by clinical examination and laboratory testing. Administer systemic corticosteroids before and after ELEVIDYS infusion. Continue to monitor liver function weekly for the first 3 months after infusion and continue until results are unremarkable [see Dosage and Administration (2.1, 2.2, 2.4)].
- Instruct patients to maintain proximity to an appropriate healthcare facility, as determined by the healthcare provider, for at least 2 months following ELEVIDYS infusion [see Dosage and Administration (2.1)].
- Obtain prompt consultation with a specialist (e.g., gastroenterologist or hepatologist) if acute serious liver injury or impending acute liver failure is suspected [see Dosage and Administration (2.2), Warnings and Precautions (5.1)].

1 INDICATIONS AND USAGE

ELEVIDYS is indicated for the treatment of patients 4 years of age and older with Duchenne muscular dystrophy (DMD), who are ambulatory and have a confirmed mutation in the DMD gene [see Clinical Pharmacology (12.2), Clinical Studies (14)].

Limitations of Use:

ELEVIDYS is not recommended in patients with:

- Preexisting liver impairment (defined as gamma-glutamyl transferase [GGT] > 2 x upper limit of normal or total bilirubin > the upper limit of normal not due to Gilbert's syndrome) or active hepatic viral infection due to the high risk of acute serious liver injury and acute liver failure.
- Recent vaccination (within 4 weeks of treatment) due to immunogenicity and potential safety concerns.
- Active or recent (within 4 weeks) infections due to safety concerns.

2 DOSAGE AND ADMINISTRATION

For single-dose intravenous infusion only.

2.1 Critical Dosing Information

- Instruct patients to maintain proximity to an appropriate healthcare facility, as determined by the healthcare provider, for at least 2 months following ELEVIDYS infusion.
- Prior to ELEVIDYS infusion:
  - Select patients for treatment with ELEVIDYS with anti-AAVrh74 total binding antibody titers <1:400. An FDA-authorized test for the detection of anti-AAVrh74 total binding antibodies is not currently available. Currently available tests may vary in accuracy and design.
  - Avoid ELEVIDYS administration in patients with elevated anti-AAVrh74 total binding antibody titers (≥1:400) [Clinical Pharmacology (12.6)].
  - Due to the increased risk of serious systemic immune response, postpone ELEVIDYS in patients with active or recent (within 4 weeks) infections [see Warnings and Precautions (5.2)].
  - Assess liver function (clinical examination and laboratory testing including aspartate aminotransferase (AST), alanine aminotransferase (ALT), gamma-glutamyl transferase (GGT), albumin, activated partial thromboplastin time (aPTT), international normalized ratio (INR), and total bilirubin) [see Dosage and Administration (2.4), Warnings and Precautions (5.1), Use in Specific Populations (8.6)].
  - Obtain platelet count and troponin-I levels [see Dosage and Administration (2.4), Warnings and Precautions (5.3)].
- Do not re-administer ELEVIDYS.

2.2 Recommended Dose

The recommended dose of ELEVIDYS is 1.33 × 10^14 vector genomes per kilogram (vg/kg) of body weight (or 10 mL/kg body weight) for patients weighing less than 70 kg or 9.31 × 10^15 vg total fixed dose for patients weighing 70 kg or greater.

For the number of vials required, refer to Table 10 [see How Supplied/Storage and Handling (16.1)].

Calculate the dose as follows:

ELEVIDYS dose (in mL) = patient body weight (rounded to the nearest kilogram) x 10

The multiplication factor 10 represents the per kilogram dose (1.33 × 10^14 vg/kg) divided by the amount of vector genome copies per mL of the ELEVIDYS suspension (1.33 × 10^13 vg/mL).

Number of ELEVIDYS vials needed = ELEVIDYS dose (in mL) divided by 10.

Example: Calculation of volume needed for a 19.5 kg patient
19.5 kg rounded to the nearest kilogram = 20 kg
20 kg × 10 = 200 mL

Number of ELEVIDYS vials needed = 200 divided by 10, rounded to the nearest number of vials = 20 vials

Administer corticosteroids to reduce the risk of immune responses to the AAVrh74 vector after administration of ELEVIDYS [see Clinical Pharmacology (12.6)]. Start corticosteroids 1 day prior to ELEVIDYS infusion based on the schedule outlined in Table 1 below. Continue this regimen for a minimum of 60 days after the infusion, unless earlier tapering is clinically indicated.

Table 1: Recommended pre- and post-infusion oral corticosteroid dosing
Baseline corticosteroid dosinga | Peri-ELEVIDYS infusion corticosteroid dose (prednisone equivalent) b | Recommended maximum total daily oral dose (prednisone equivalent) b
Daily or intermittent dose | Start 1 day prior to infusion: 1 mg/kg/day (and continue baseline dose) | 60 mg/day
High dose for 2 days per week | Start 1 day prior to infusion: 1 mg/kg/day taken on days without high-dose corticosteroid treatment (and continue baseline dose) | 60 mg/day
Not on corticosteroids | Start 1 week prior to infusion: 1.5 mg/kg/day | 60 mg/day
a Patient continues to receive this dose
b Corticosteroids other than prednisone and prednisolone have not been studied for use as a peri-ELEVIDYS infusion corticosteroid

Modify oral corticosteroid doses according to Table 2 for patients with liver function abnormalities (e.g., GGT >= 3 times baseline, total bilirubin > ULN) following ELEVIDYS infusion. Consider IV bolus corticosteroids instead of oral corticosteroids for GGT or bilirubin elevations that do not respond after 1 week of increased oral corticosteroids. Consult with a specialist experienced in immunosuppressive therapy for additional interventions as needed.

Obtain prompt consultation with a specialist (e.g., gastroenterologist or hepatologist) if acute serious liver injury or impending acute liver failure is suspected.

Taper the additional peri-ELEVIDYS corticosteroids for patients previously taking corticosteroids at baseline back to baseline dose over 2 weeks, or longer as needed. Taper the peri-ELEVIDYS corticosteroids for patients not previously taking corticosteroids at baseline back to no corticosteroids over 4 weeks, or longer as needed. Do not stop corticosteroids abruptly.

Table 2: Recommended oral corticosteroid regimen dose modification for liver function abnormalities following ELEVIDYS infusiona
Peri-ELEVIDYS infusion corticosteroid dosing | Modified oral corticosteroid dose following ELEVIDYS infusion (prednisone equivalent) b c | Recommended maximum total daily oral dose (prednisone equivalent) b c
Baseline + 1 mg/kg/day | Increase to 2 mg/kg/day (and continue baseline dose) | 120 mg/day
Baseline + 1 mg/kg/day taken on days without high-dose corticosteroid treatment | Increase to 2 mg/kg/day taken on days without high-dose corticosteroid treatment (and continue baseline dose) | 120 mg/day
1.5 mg/kg/day | Increase from 1.5 mg/kg/day to 2.5 mg/kg/day | 120 mg/day
a GGT >= 3 times baseline and/or other clinically significant liver function abnormalities (e.g., total bilirubin > ULN) following infusion.
b Consider IV bolus corticosteroids instead of oral corticosteroids for GGT or bilirubin elevations that do not respond after 1 week of increased oral corticosteroids. Consult with a specialist experienced in immunosuppressive therapy for additional interventions as needed.
c Corticosteroids other than prednisone and prednisolone have not been studied for use as a peri-ELEVIDYS infusion corticosteroid.

2.3 Preparation

General precautions

- Prepare ELEVIDYS using aseptic technique.
- Verify the required dose of ELEVIDYS based on the patient's body weight.
- Confirm that the kit contains sufficient number of vials to prepare the ELEVIDYS infusion for the patient.
- Visually inspect parenteral drug products for particulate matter and discoloration prior to administration, whenever suspension and container permit. ELEVIDYS may contain white to off-white particles.

Recommended supplies and materials:

- 60 mL siliconized polypropylene syringes
- 21-gauge maximum or smaller stainless steel needles

Preparing ELEVIDYS infusion

1. Thaw ELEVIDYS before use.
  - When thawed in the refrigerator, ELEVIDYS vials are stable for up to 14 days in the refrigerator (2°C to 8°C [36º F to 46º F]) when stored in the upright position.
  - Frozen ELEVIDYS vials will thaw in approximately 2 hours when placed at room temperature (up to 25°C [77ºF]) when removed from original packaging.
  - Thawed ELEVIDYS is stable for up to 24 hours at room temperature (up to 25°C [77ºF]).
2. Inspect vials to ensure no ice crystals are present prior to preparation.
3. When thawed, swirl gently.
  - Do not shake.
  - Do not refreeze.
  - Do not place back in the refrigerator.
4. Visually inspect each vial of ELEVIDYS. ELEVIDYS is a clear, colorless liquid that may have some opalescence. ELEVIDYS may contain white to off-white particles.
  - Do not use if the suspension in the vials is cloudy or discolored.
5. Remove the plastic flip-off cap from the vials and disinfect the rubber stopper with a sterilizing agent (e.g., alcohol wipes).
6. Withdraw 10 mL of ELEVIDYS from each vial provided in the customized ELEVIDYS kit (refer to Table 10).
  - Do not use filter needles during preparation of ELEVIDYS.
  - Multiple syringes will be required to withdraw the required volume.
  - Remove air from the syringes and cap the syringes.
7. Maintain syringes at room temperature prior to and during administration.

2.4 Administration

Recommended supplies and materials:

- Syringe infusion pump
- 0.2-micron PES* in-line filter with a large surface area. To avoid the risk of occlusions, the use of smaller pediatric in-line filters (e.g., less than 10 cm^2 surface area) is not recommended.
- PVC* (non-DEHP*) IV infusion tubing, and polyurethane catheter

*PVC = Polyvinyl chloride, DEHP = Di(2-ethylhexyl) phthalate, PES = Polyether sulfone

Administer ELEVIDYS as a single-dose intravenous infusion through a peripheral venous catheter:

ELEVIDYS should be administered in a setting where treatment for infusion-related reactions is immediately available [see Warnings and Precautions (5.4)]. Do not infuse ELEVIDYS at a rate of 10 mL/kg/hour or faster.

Consider application of a topical anesthetic to the infusion site prior to administration of IV insertion.

Recommend inserting a back-up catheter.

1. Flush the intravenous access line with 0.9% Sodium Chloride Injection prior to the ELEVIDYS infusion at the same infusion rate.
2. Administer ELEVIDYS via intravenous infusion using a syringe infusion pump with an in-line 0.2-micron filter at a duration of approximately 1 to 2 hours, or longer at care team discretion, through a peripheral limb vein.
3. Infuse at a rate of less than 10 mL/kg/hour.
  - Do not administer ELEVIDYS as an intravenous push.
  - Do not infuse ELEVIDYS in the same intravenous access line with any other product.
  - Use ELEVIDYS within 12 hours after drawing into syringe. Discard the ELEVIDYS-containing syringe(s) if infusion of the drug has not been completed within the 12-hour timeframe.
4. In the event of an infusion-related reaction during administration [see Warnings and Precautions (5.4)]:
  - Slow or stop the infusion based on patient's clinical presentation.
  - Discontinue infusion for anaphylaxis.
  - Administer treatment as needed to manage infusion-related reaction.
  - ELEVIDYS infusion may be restarted at a lower rate after the infusion-related reaction has resolved at the discretion of the physician, based on severity of patient's clinical presentation.
  - If the ELEVIDYS infusion needs to be stopped and restarted, ELEVIDYS should be infused within 12 hours after drawing into the syringe [see How Supplied/Storage and Handling (16.2)].
5. Flush the intravenous access line with 0.9% Sodium Chloride Injection after the ELEVIDYS infusion.
  - Discard unused ELEVIDYS [see How Supplied/Storage and Handling (16.2)].
  - Dispose of the needle and syringe [see How Supplied/Storage and Handling (16.2)].

Monitoring Post-ELEVIDYS Administration

- Assess liver function (clinical exam, AST, ALT, GGT, albumin, aPTT, INR, and total bilirubin) weekly for the first 3 months. Continue monitoring if clinically indicated, until results are unremarkable (e.g., normal clinical exam, GGT and total bilirubin levels return to near baseline levels) [see Warnings and Precautions (5.1), Specific Populations (8.6)].
- Obtain platelet counts weekly for the first two weeks [see Adverse Reactions (6.1)]. Continue monitoring if clinically indicated.
- Measure troponin-I weekly for the first month [see Warnings and Precautions (5.3)]. Continue monitoring if clinically indicated, until results return to near baseline levels or stabilize.

3 DOSAGE FORMS AND STRENGTHS

ELEVIDYS is a preservative-free, sterile, clear, colorless liquid that may have some opalescence and may contain white to off-white particles.

ELEVIDYS is a suspension for intravenous infusion with a nominal concentration of 1.33 × 10^13 vg/mL.

ELEVIDYS is provided in a customized kit containing ten to seventy 10 mL single-dose vials, with each kit constituting a dosage unit based on the patient's body weight [see How Supplied/Storage and Handling (16.1)].

4 CONTRAINDICATIONS

ELEVIDYS is contraindicated in patients with any deletion in exon 8 and/or exon 9, including a deletion of any portion or the entirety of these exons, in the DMD gene [see Warnings and Precautions (5.5)].

5 WARNINGS AND PRECAUTIONS

5.1 Acute Serious Liver Injury and Acute Liver Failure

Acute serious liver injury marked by elevations of liver enzymes (e.g., GGT, ALT) and total bilirubin and acute liver failure, has occurred with ELEVIDYS. Onset of the liver injury typically begins within 8 weeks after administration of ELEVIDYS. In non-ambulatory patients treated with ELEVIDYS, acute liver failure with fatal outcome has occurred in the clinical and post-marketing settings.

Life-threatening mesenteric vein thrombosis, complicated by bowel ischemia and necrosis, and portal hypertension have been reported following acute liver injury associated with ELEVIDYS in a non-ambulatory patient [see Adverse Reactions (6.2)].

Patients with preexisting liver impairment, chronic hepatic condition, or acute liver disease (e.g., acute hepatic viral infection) may be at higher risk of acute serious liver injury or acute liver failure. Postpone ELEVIDYS administration in patients with acute liver disease until resolved or controlled. Patients with hepatic impairment, acute liver disease, chronic hepatic condition or elevated GGT have not been studied in clinical trials with ELEVIDYS [see Specific Populations (8.6)].

In clinical studies, liver function test increased (including increases in GGT, ALT, AST, or total bilirubin) was commonly reported typically within 8 weeks following ELEVIDYS infusion, with the majority of cases being asymptomatic [see Adverse Reactions (6.1)]. Most cases resolved spontaneously or with systemic corticosteroids and resolved without clinical sequelae within 2 months.

Prior to ELEVIDYS administration, perform liver enzyme test [see Dosage and Administration (2.1)]. Monitor liver function (clinical examination, AST, ALT, GGT, albumin, aPTT, INR, and total bilirubin) weekly for the first 3 months following ELEVIDYS infusion. Continue monitoring if clinically indicated, until results are unremarkable (e.g., normal clinical exam, GGT and total bilirubin levels return to near baseline levels) [see Dosage and Administration (2.4)].

Systemic corticosteroid treatment is recommended for patients before and after ELEVIDYS infusion [see Dosage and Administration (2.2)]. Adjust corticosteroid regimen when indicated [see Dosage and Administration (2.2)]. Obtain prompt consultation with a specialist (e.g., gastroenterologist or hepatologist) if acute serious liver injury or impending acute liver failure is suspected.

5.2 Serious Infections

Increased susceptibility to serious infections may occur due to concomitant administration of corticosteroid regimen and additional immunosuppressants, and ELEVIDYS. Serious respiratory infections, including with fatal outcomes, have occurred in patients taking immunosuppressant corticosteroids required for ELEVIDYS administration [see Adverse Reactions (6.2)].

Monitor patients for signs and symptoms of infection before and after ELEVIDYS administration and treat appropriately. Administer immunizations according to best clinical practices and immunization guidelines prior to initiation of the corticosteroid regimen required before ELEVIDYS infusion [see Drug Interactions (7)].

Avoid administration of ELEVIDYS to patients with active infections.

5.3 Myocarditis

Acute, serious, life-threatening myocarditis and troponin-I elevations have been observed within 24 hours to more than 1 year following ELEVIDYS infusion [see Adverse Reactions (6.1)].

If a patient experiences myocarditis, those with pre-existing left ventricle ejection fraction (LVEF) impairment may be at higher risk of adverse outcomes. Patients with moderate to severe LVEF impairment have not been studied in clinical trials with ELEVIDYS.

Monitor troponin-I before ELEVIDYS infusion and weekly for the first month following infusion [see Dosage and Administration (2.4)]. Continue monitoring if clinically indicated, until results return to near baseline levels or stabilize. More frequent monitoring may be warranted in the presence of cardiac symptoms, such as chest pain or shortness of breath.

Advise patients to contact a physician immediately if they experience cardiac symptoms.

5.4 Infusion-related Reactions

Infusion-related reactions, including hypersensitivity reactions and anaphylaxis, have occurred during or up to several hours following ELEVIDYS administration. Closely monitor patients during and for at least 3 hours after the end of infusion for signs and symptoms of infusion-related reactions including tachycardia, tachypnea, lip swelling, difficulty breathing, nasal flaring, urticaria, flushing, lip pruritus, rash, cheilitis, vomiting, nausea, rigors and pyrexia.

ELEVIDYS should be administered in a setting where treatment for infusion-related reactions is immediately available.

In the event of an infusion-related reaction, administration of ELEVIDYS may be slowed or stopped based on the severity of the patient's clinical presentation. Administer treatment as needed to manage infusion-related reactions based on the severity of patient's signs and symptoms. [see Dosage and Administration (2.4)]. If the infusion was stopped, ELEVIDYS infusion may be restarted at a lower rate once patient's symptoms have resolved, at the discretion of the physician. Discontinue infusion for anaphylaxis.

5.5 Immune-mediated Myositis

Immune-mediated myositis, including serious and life-threatening events, has occurred approximately 1 month following ELEVIDYS infusion [see Adverse Reactions (6)]. Signs and symptoms include severe muscle weakness, including dysphagia, dyspnea, dysphonia, and hypophonia.

These immune reactions may be due to a T-cell based response against specific regions of the micro-dystrophin transgenic protein. Severe to life-threatening immune-mediated myositis has been reported in patients with deletions including portions of exons 1-17 and/or exons 59-71 of the DMD gene. ELEVIDYS is contraindicated in patients with any deletion in exon 8 and/or exon 9, including a deletion of any portion or the entirety of these exons, in the DMD gene due to the increased risk for a severe immune-mediated myositis reaction [see Contraindications (4)].

Regardless of genetic mutation, advise patients to contact a physician immediately if they experience any unexplained increased muscle pain, tenderness, or weakness, including dysphagia, dyspnea, dysphonia, or hypophonia as these may be symptoms of myositis. Consider additional immunomodulatory treatment based on patient's clinical presentation and medical history if these symptoms occur.

5.6 Pre-existing Immunity against AAVrh74

In AAV-vector based gene therapies, preexisting anti-AAV antibodies may impede transgene expression at desired therapeutic levels. Following treatment with ELEVIDYS all patients developed anti-AAVrh74 antibodies. Perform baseline testing for the presence of anti-AAVrh74 total binding antibodies prior to ELEVIDYS administration [see Dosage and Administration (2.1)].

ELEVIDYS administration is not recommended in patients with elevated anti-AAVrh74 total binding antibody titers (≥1:400).

6 ADVERSE REACTIONS

6.1 Clinical Trials Experience

Because clinical trials are conducted under widely varying conditions, adverse reaction rates observed in the clinical trials of a drug cannot be directly compared to rates in the clinical trials of another drug and may not reflect the rates observed in practice.

The safety data described in this section reflect exposure to a one-time intravenous infusion of ELEVIDYS in 156 male patients with a confirmed mutation of the DMD gene in four clinical studies, including one completed open-label study, one ongoing open-label study, and two studies that included a double-blind, placebo-controlled period. Prior to ELEVIDYS infusion, patients in the ELEVIDYS treatment group had a mean age of 6.7 years (range: 3 to 20) and mean weight of 24.6 kg (range: 12.5 to 80.1). 144 patients received the recommended dose of 1.33 × 10^14 vg/kg, and 12 received a lower dose. Table 3 below presents adverse reactions from these four clinical studies.

The most common adverse reactions (incidence ≥5%) across all studies are summarized in Table 3.

Adverse reactions were typically seen within the first 2 weeks (nausea, vomiting, thrombocytopenia, pyrexia), the first month (myocarditis, troponin-I increased) or within the first 2 months (immune-mediated myositis, liver injury). Vomiting may occur as early as on the day of the infusion.

Table 3. Adverse reactions (Incidence ≥5%) following treatment with ELEVIDYS in Clinical Studies
Adverse reactions | ELEVIDYS (N=156) %
Vomiting | 65
Nausea | 43
Liver injurya | 40
Pyrexia | 28
Thrombocytopeniab c | 8
Troponin-I increased d | 8
a Includes: AST increased, ALT increased, GGT increased, GLDH increased, GLDH level abnormal, Hepatotoxicity, Hepatic enzyme increased, Hypertransaminasemia, Liver function test increased, Liver injury, Transaminases increased, Blood bilirubin increased
b Includes: Thrombocytopenia, Platelet count decreased
c Transient, mild, asymptomatic decrease in platelet counts
d Includes: Troponin I increased, Troponin increased, Troponin I abnormal

In clinical trials, immune-mediated myositis was observed in 2 of 6 patients with deletion mutations involving exon 8 and/or 9 in the DMD gene [see Contraindications (4), and Warnings and Precautions (5.5)].

In the double-blind, placebo-controlled trial, Study 3 Part 1, patients 4 to 7 years of age (N=125) received either ELEVIDYS (N=63) at the recommended dose of 1.33 × 10^14 vg/kg or placebo (N=62). Table 4 below presents the most frequent adverse reactions from Study 3 Part 1.

Table 4. Adverse reactions occurring in ELEVIDYS-treated patients and at least twice more frequently than with placebo in Study 3 Part 1
Adverse reactions | ELEVIDYS (N=63) % | Placebo (N=62) %
Vomiting | 64 | 19
Nausea | 40 | 13
Liver injurya | 41 | 8
Pyrexia | 32 | 24
Thrombocytopeniabc | 3 | 0
a Includes: AST increased, ALT increased, GGT increased, GLDH increased, GLDH level abnormal, Hepatotoxicity, Hepatic enzyme increased, Hypertransaminasemia, Liver function test increased, Liver injury, Transaminases increased.
b Includes: platelet count decreased, thrombocytopenia
c Transient, mild, asymptomatic decrease in platelet counts

6.2 Postmarketing Experience

The following adverse reactions have been identified during post-approval use of ELEVIDYS. Because these reactions are reported voluntarily from a population of uncertain size, it is not always possible to reliably estimate their frequency or establish a causal relationship to drug exposure.

Hepatobiliary Disorders: Acute liver injury, acute liver failure, including fatal outcome and life-threatening mesenteric vein thrombosis [see Warnings and Precautions (5.1)]

Infections and Infestations: Bacterial and viral respiratory infections, including fatal outcome [see Warnings and Precautions (5.2)]

Immune System Disorders: Infusion-related reactions, including hypersensitivity reactions and anaphylaxis, have occurred during or up to several hours following ELEVIDYS administration [see Warnings and Precautions (5.4)].

Musculoskeletal and connective tissue disorders: Immune-mediated myositis [see Warnings and Precautions (5.5)].

7 DRUG INTERACTIONS

Prior to initiating the corticosteroid regimen required before ELEVIDYS administration, consider the patient's vaccination status. Patients should, if possible, be brought up to date with all immunizations in agreement with current immunization guidelines. Vaccinations should be completed at least 4 weeks prior to initiation of the corticosteroid regimen.

8 USE IN SPECIFIC POPULATIONS

8.1 Pregnancy

Risk Summary

ELEVIDYS is not intended for use in pregnant women.

In the U.S. general population, the estimated background risks of major birth defects and miscarriage in clinically recognized pregnancies is 2% to 4% and 15% to 20%, respectively.

8.2 Lactation

Risk Summary

There is no information available on the presence of ELEVIDYS in human milk, the effects on the breastfed infant, or the effects on milk production.

8.4 Pediatric Use

The safety and effectiveness of ELEVIDYS for the treatment of Duchenne muscular dystrophy has been established in pediatric patients at least 4 years of age with a confirmed mutation in the DMD gene. The use of ELEVIDYS in pediatric patients was supported by evidence from three adequate and well controlled clinical studies which included 144 pediatric patients aged 4 years of age and older [see Adverse Reactions (6), Clinical Pharmacology (12.2), Clinical Studies (14)].

8.5 Geriatric Use

The safety and efficacy of ELEVIDYS in geriatric patients with DMD have not been studied.

8.6 Hepatic Impairment

The safety and efficacy of ELEVIDYS in patients with hepatic impairment or elevated GGT have not been studied.

Postpone ELEVIDYS administration in patients with acute liver disease until resolved or controlled. Treatment with ELEVIDYS should be carefully considered in patients with preexisting liver impairment or chronic hepatic viral infection. These patients may be at increased risk of acute serious liver injury or acute liver failure [see Warnings and Precautions (5.1)].

In clinical trials, liver function test increase was commonly reported in patients following ELEVIDYS infusion [see Warnings and Precautions (5.1), Adverse Reactions (6.1)].

11 DESCRIPTION

ELEVIDYS (delandistrogene moxeparvovec-rokl) is a recombinant gene therapy designed to deliver the gene encoding the ELEVIDYS micro-dystrophin protein. ELEVIDYS is a non-replicating, recombinant, adeno-associated virus serotype rh74 (AAVrh74) based vector containing the ELEVIDYS micro-dystrophin transgene under the control of the MHCK7 promoter. The genome within the ELEVIDYS AAVrh74 vector contains no viral genes and consequently is incapable of replication or reversion to a replicating form. The micro-dystrophin protein expressed by ELEVIDYS is a shortened version (138 kDa, compared to 427 kDa size of dystrophin expressed in normal muscle cells) that contains selected domains of dystrophin expressed in normal muscle cells.

ELEVIDYS is a preservative-free, sterile, clear, colorless liquid that may have some opalescence and may contain white to off-white particles. ELEVIDYS is a suspension for intravenous infusion with a nominal concentration of 1.33 ×10^13 vg/mL and supplied in a single-dose 10 mL vial. Each vial contains an extractable volume of 10 mL and the following excipients: 200mM sodium chloride, 13 mM tromethamine HCl, 7 mM tromethamine, 1mM magnesium chloride, 0.001% poloxamer 188, with a pH of 8.0 ± 0.3.

12 CLINICAL PHARMACOLOGY

12.1 Mechanism of Action

ELEVIDYS is the recombinant gene therapy product that is comprised of a non-replicating, recombinant, adeno-associated virus (AAV) serotype rh74 (AAVrh74) capsid and a single-stranded DNA expression cassette flanked by inverted terminal repeats (ITRs) derived from AAV2. The cassette contains: 1) an MHCK7 gene regulatory component comprising a creatine kinase 7 promoter and an α-myosin heavy chain enhancer, and 2) the DNA transgene encoding the engineered micro-dystrophin protein.

Vector/Capsid: Clinical and nonclinical studies have demonstrated AAVrh74 serotype transduction in skeletal muscle cells. Additionally, in nonclinical studies, AAVrh74 serotype transduction has been demonstrated in cardiac and diaphragm muscle cells.

Promoter: The MHCK7 promoter/enhancer drives transgene expression and has been shown in animal models to drive transgenic micro-dystrophin protein expression predominantly in skeletal muscle (including diaphragm) and cardiac muscle. In clinical studies, muscle biopsy analyses have confirmed micro-dystrophin expression in skeletal muscle.

Transgene: DMD is caused by a mutation in the DMD gene resulting in lack of functional dystrophin protein. ELEVIDYS carries a transgene encoding a micro-dystrophin protein consisting of selected domains of dystrophin expressed in normal muscle cells.

ELEVIDYS micro-dystrophin has been demonstrated to localize to the sarcolemma.

12.2 Pharmacodynamics

In 92 patients who received ELEVIDYS in clinical studies, micro-dystrophin protein expression from muscle biopsies (gastrocnemius or biceps brachii) was quantified by western blot and localized by immunofluorescence staining (fiber intensity and percentage micro-dystrophin).

Micro-dystrophin expression (expressed as change from baseline) in ELEVIDYS-treated patients as measured by western blot was the primary objective of Study 1 and Study 2, and a key secondary objective for Study 3. Muscle biopsies were obtained at baseline prior to ELEVIDYS infusion and at Week 12 after ELEVIDYS infusion in all patients. The absolute quantity of micro-dystrophin was measured by western blot assay, adjusted by muscle content and expressed as a percent of control (levels of wild-type dystrophin in patients without DMD or Becker muscular dystrophy) in muscle biopsy samples. Study 1 and 2 results of patients receiving 1.33 × 10^14 vg/kg ELEVIDYS are presented in Table 5.

Table 5. Micro-Dystrophin Expression in Study 1 and Study 2 at Week 12 from Baseline (Western Blot Assay)abc
Western blot (% of micro-dystrophin compared to control) | Study 1 Part 1 (n=6) | Study 1 Part 2 (n=21) | Study 2 Ambulatory (n=40)
Mean change from baseline (SD) | 43.4 (48.6) | 40.7 (32.3) | 51.0 (47)
Median change from baseline (Min, Max) | 24.3 (1.6, 116.3) | 40.8 (0.0, 92.0) | 46.9 (1.9, 197.3)
a All patients received 1.33 x 10^14 vg/kg, as measured by ddPCR
b Change from baseline was statistically significant
c Adjusted for muscle content. Control was level of wild-type (normal) dystrophin in normal muscle.

In Study 3 Part 1, muscle biopsies were obtained at Week 12 in 31 patients. For the ELEVIDYS-treated patients, the mean micro-dystrophin expression at Week 12 was 34.3% (N=17, SD: 41.0%), compared to placebo patients of 0% (N=14, SD: 0%).

Assessment of micro-dystrophin levels can be meaningfully influenced by differences in sample processing, analytical technique, reference materials, and quantitation methodologies. Therefore, valid comparisons of micro-dystrophin measurements obtained from different assays cannot be made.

12.3 Pharmacokinetics

Vector Distribution and Vector Shedding

Nonclinical Data

Biodistribution of ELEVIDYS was evaluated in tissue samples collected from healthy mice and DMDmdx mice following intravenous administration in toxicology studies. At 12 weeks following ELEVIDYS administration at dose levels of 1.33 ×10^14 to 4.02 ×10^14 vg/kg, vector DNA was detected in all major organs with the highest quantities detected in the liver, followed by lower levels in the heart, adrenal glands, skeletal muscle, and aorta. ELEVIDYS was also detected at low levels in the spinal cord, sciatic nerve and gonads (testis). Protein expression of micro-dystrophin was highest in cardiac tissue, exceeding physiologic dystrophin expression levels in healthy mice, with lower levels in the skeletal muscle and diaphragm. In some studies, micro-dystrophin was also detected at low levels in the liver.

Clinical Data

Following IV administration, ELEVIDYS vector genome undergoes distribution via systemic circulation and distributes into target muscle tissues followed by elimination in the urine and feces. ELEVIDYS biodistribution and tissue transduction are detected in the target muscle tissue groups and quantified in the gastrocnemius or biceps femoris biopsies obtained from patients with mutations in the DMD gene. Evaluation of ELEVIDYS vector genome exposure in clinical muscle biopsies at Week 12 post-dose expressed as copies per nucleus revealed ELEVIDYS drug distribution and transduction with a mean change from baseline of 2.91 and 3.44 copies per nucleus at the recommended dose of 1.33 × 10^14 vg/kg for Study 1 and Study 2 Cohort 1, respectively.

In Study 2 Cohorts 1-3, the biodistribution and vector shedding of ELEVIDYS in the serum and excreta were quantified, respectively. The mean maximum concentration (Cmax) in the serum was 0.0055 × 10^13 copies/mL and 2.78 × 10^6 copies/mL in the urine, 7.86 × 10^7 copies/mL in the saliva, and 4.87 × 10^7 copies/μg in the feces. The median time to achieve maximum concentration (Tmax) was 5.8 hours post-dose in the serum, followed by 6.7 hours, 6.5 hours and 13 days post-dose in the saliva, urine, and feces, respectively. The median time to achieve first below limit of quantification (BLOQ) sample followed by 2 consecutive BLOQ samples was 55 days post-dose for serum. The median time to achieve complete elimination as the first below limit of detection (BLOD) sample followed by 2 consecutive BLOD samples were 49.8 days, 78 days and 162 days post-dose for saliva, urine and feces, respectively. The estimated elimination half-life of ELEVIDYS vector genome in the serum is approximately 12 hours, and the majority of the drug is expected to be cleared from the serum by 1-week post-dose. In the excreta, the estimated elimination half-life of ELEVIDYS vector genome is approximately 40 hours, 55 hours, and 60 hours in the urine, feces, and saliva, respectively. As an AAV-based gene therapy that consists of a protein capsid containing the transgene DNA genome of interest, ELEVIDYS capsid proteins are broken down through proteasomal degradation following AAV entry into target cells. As such, ELEVIDYS is not likely to exhibit the drug-drug interaction potential mediated by known drug metabolizing enzymes (cytochrome P450-based) and drug transporters.

12.6 Immunogenicity

The observed incidence of anti-AAVrh74 antibodies is highly dependent on the sensitivity and specificity of the assay. Differences in assay methods preclude meaningful comparisons of the incidence of anti-AAVrh74 antibodies in the studies described below with the incidence of anti-AAVrh74 antibodies in other studies.

In ELEVIDYS clinical studies, patients were required to have baseline anti-AAVrh74 total binding antibodies of <1:400, measured using an investigational total binding antibody enzyme-linked immunosorbent assay (ELISA), and only patients with baseline anti-AAVrh74 total binding antibodies <1:400 were enrolled in those studies.

Across clinical studies evaluating a total of 156 patients, elevated anti-AAVrh74 total binding antibodies titers were observed in all patients following a one-time ELEVIDYS infusion. Anti-AAVrh74 total binding antibody titers reached at least 1:3200 in every patient, and the maximum titers exceeded 1:26,214,400 in certain patients. The safety of re-administration of ELEVIDYS or any other AAVrh74 vector-based gene therapy in the presence of high anti-AAVrh74 total binding antibody titer has not been evaluated in humans [see Warnings and Precautions (5.6)].

There is insufficient data to assess whether the observed anti-AAVrh74 antibodies titers have clinically significant effect on pharmacokinetics, pharmacodynamics, safety, and efficacy of ELEVIDYS.

13 NONCLINICAL TOXICOLOGY

13.1 Carcinogenesis, Mutagenesis, Impairment of Fertility

No animal studies have been performed to evaluate the effects of ELEVIDYS on carcinogenicity, mutagenesis, or impairment of fertility.

14 CLINICAL STUDIES

The efficacy of ELEVIDYS was evaluated in two double-blind, placebo-controlled studies (Study 1 [NCT 03769116] and Study 3 [NCT 05096221]) and one open-label study (Study 2 [NCT 04626674]) in which a total of 214 male patients with a confirmed disease-causing mutation in the DMD gene were dosed.

Study 1

Study 1 is a completed multi-center study including:

- Part 1: a 48-week, randomized, double-blind, placebo-controlled period
- Part 2: a 48-week period that began following completion of Part 1. Patients who received placebo during Part 1 were treated with ELEVIDYS, and patients treated with ELEVIDYS during Part 1 received placebo.

The study population consisted of male ambulatory DMD patients (N=41) aged 4 through 7 years with either a confirmed frameshift mutation, or a premature stop codon mutation between exons 18 to 58 in the DMD gene.

Patients were randomized 1:1 to receive either ELEVIDYS (N=20) or placebo (N=21), as a single intravenous infusion via a peripheral limb. Randomization was stratified by age (i.e., aged 4 to 5 years vs. aged 6 to 7 years). In the 4 through 5-year-old subgroup, the mean age, mean weight and mean NSAA total score (range) for the ELEVIDYS-treated patients (n=8) were 4.98 years, 20.1 kg and 20.1 (17-23), and for the placebo patients (n=8) were 5.15 years, 19.8 kg and 20.4 (15-24). In the ELEVIDYS group, eight patients received 1.33 × 10^14 vg/kg of ELEVIDYS, and 12 patients received lower doses. Key demographic and baseline characteristics are presented in Table 6.

Table 6: Key Demographic and Baseline Characteristics (Study 1 Part 1)
Characteristic | All (n=41) | ELEVIDYS (n=20) | Placebo (n=21)
Race (%) Asian/Black or African American/White/Other | 12/0/73/15 | 20/0/65/15 | 5/0/81/14
Ethnicity (%) Hispanic or Latino/ Other | 12/88 | 5/95 | 19/81
Mean age [range] (years) | 6.3 [4.3 to 7.9] | 6.3 [4.5 to 7.9] | 6.2 [4.3 to 7.9]
Mean weight [range] (kg) | 22.4 [15.0 to 34.5] | 23.3 [18.0 to 34.5] | 21.6 [15.0 to 30.0]
Mean NSAA total score [range] | 21.2 [13 to 29] | 19.8 [13 to 26] | 22.6 [15 to 29]
Mean time to rise from floor [range] (seconds) | 4.3 [2.7 to 10.4] | 5.1 [3.2 to 10.4] | 3.6 [2.7 to 4.8]

All patients were on a stable dose of corticosteroids for DMD for at least 12 weeks prior to ELEVIDYS infusion. All randomized patients had baseline anti-AAVrh74 antibody titers <1:400 as determined by an investigational total binding antibody ELISA.

One day prior to treatment with ELEVIDYS or placebo, the patient's background dose of corticosteroid for DMD was increased to at least 1 mg/kg of a corticosteroid (prednisone equivalent) daily and was continued at this level for at least 60 days after the infusion, unless earlier tapering was clinically indicated.

The efficacy outcomes of Study 1 were to evaluate expression of micro-dystrophin in skeletal muscle, and to evaluate the effect of ELEVIDYS on the North Star Ambulatory Assessment (NSAA) total score.

Results of micro-dystrophin measured by western blot are presented in Table 5 [see Clinical Pharmacology (12.2)].

The change in NSAA total score was assessed from baseline to Week 48 after infusion of ELEVIDYS or placebo. The difference between the ELEVIDYS and placebo groups was not statistically significant (p=0.37). The least squares (LS) mean changes in NSAA total score from baseline to Week 48 was 1.7 (standard error [SE]: 0.6) points for the ELEVIDYS group and 0.9 (SE: 0.6) points for the placebo group.

Exploratory subgroup analyses showed that for patients aged 4 through 5 years, the LS mean changes (SE) in NSAA total score from baseline to Week 48 were 4.3 (0.7) points for the ELEVIDYS group, and 1.9 (0.7) points for the placebo group, a numerical advantage for ELEVIDYS. For patients aged 6 through 7 years, the LS mean changes (SE) in NSAA total score from baseline to Week 48 were -0.2 (0.7) points for the ELEVIDYS group and 0.5 (0.7) points for the placebo group, a numerical disadvantage for ELEVIDYS.

Study 2

Study 2 is an ongoing, open-label, multi-center study which includes 5 cohorts of 48 male DMD patients.

Patients in cohorts 1, 2 and 3 have a confirmed frameshift, splice site or premature stop codon mutation anywhere in the DMD gene, while patients in cohort 4 included patients with mutations in the DMD gene starting at or after exon 18. All patients in cohort 5 had mutations that partially or fully overlap with exons 1-17 in the DMD gene. Patients received corticosteroids for DMD before infusion according to Table 1 [see Dosage and Administration (2.2)]. All patients had baseline anti-AAVrh74 antibodies titers ≤1:400 as determined by the investigational total binding antibody ELISA. Patients received a single intravenous infusion of 1.33 × 10^14 vg/kg ELEVIDYS if they weighed less than 70 kg or 9.31 × 10^15 vg/kg total fixed dose if they weighed 70 kg or greater.

Cohorts 1, 2, 4 and 5a enrolled 40 ambulatory patients 3 to 12 years of age, with weights ranging from 12.5 to 50.5 kg, baseline mean NSAA total score of 20.3 (11 to 30), and mean time to rise from floor of 4.7 seconds (2.4 to 9.7). Cohorts 3 and 5b include 8 non-ambulatory patients 10 to 20 years of age, with weights ranging from 36.1 to 80.1 kg. Overall key demographics and key baseline characteristics by Cohort are presented in Table 7.

Table 7: Key Demographic and Baseline Characteristics for Study 2
Characteristics | All (n=48) | Cohort 1 (n=20) | Cohort 2 (n=7) | Cohort 3 a (n=6) | Cohort 4 (n=7) | Cohort 5a (n=6) | Cohort 5ba (n=2)
Race (%) Asian/Black or African American/White/Other | 8/6/77/8 | 5/5/75/15 | 14/0/71/14 | 0/0/100/0 | 14/0/86/0 | 0/33/67/0 | 50/0/50/0
Ethnicity (%) Hispanic or Latino/ Not Hispanic or Latino | 15/85 | 25/75 | 14/86 | 0/100 | 14/86 | 0/100 | 0/100
Mean age [range] (years) | 7.7 [3.2 to 20.2] | 5.8 [4.4 to 7.9] | 10.1 [8.0 to 12.1] | 15.3 [9.9 to 20.2] | 3.5 [3.2 to 3.9] | 6.7 [4.7 to 8.6] | 13.4 [12.3 to 14.6]
Mean weight [range] (kg) | 30.1 [12.5 to 80.1] | 21.2 [15.2 to 33.1] | 37.1 [28.0 to 50.5] | 59.9 [36.1 to 80.1] | 15.2 [12.5 to 16.5] | 32.1 [19.1 to 47.4] | 51.2 [43.4 to 59.0]
Mean NSAA total score [range] | 20.3 [11 to 30] | 22.1 [18 to 26] | 20.7 [17 to 26] | N/A | 12.9 [11 to 17] | 22.5 [18 to 30] | N/A
Mean time to rise from floor [range] (seconds) | 4.7 [2.4 to 9.7] | 4.2 [2.4 to 8.2] | 5.9 [3.8 to 9.7] | N/A | 5.2 [3.8 to 6.7] | 4.6 [2.5 to 7.7] | N/A
Mean Performance of Upper Limb v. 2.0 score [range] | 30.7 [18 to 42] | NA | 38.9 [33 to 42] | 22.2 [18 to 31] | NA | NA | 27.5 [21 to 34]
a NSAA and Time to rise from floor were not evaluated in non-ambulatory patients

The efficacy outcome measure of the study was to evaluate the effect of micro-dystrophin expression as measured by western blot. Results are presented in Table 5 [see Clinical Pharmacology (12.2)].

Study 3

Study 3 is a multi-center, randomized, double-blind, placebo-controlled study in which 125 ambulatory male patients aged 4 through 7 years, with a confirmed frameshift, splice site, premature stop codon, or other disease-causing mutation in the DMD gene starting at or after exon 18, were dosed. Patients with exon 45 (inclusive), or in-frame deletions, in-frame duplications, and variants of uncertain significance (“VUS”), were excluded. Patients received corticosteroids for DMD before infusion according to Table 1 [see Dosage and Administration (2.2)]. All patients had baseline anti-AAVrh74 antibodies titers <1:400 as determined by the investigational total binding antibody ELISA and received a single intravenous infusion of 1.33 × 10^14 vg/kg ELEVIDYS. Key demographic and baseline characteristics are presented in Table 8.

The efficacy outcome measure of the study was to evaluate the effect of ELEVIDYS on physical function as assessed by the NSAA total score. Key secondary outcome measures were to evaluate expression of micro-dystrophin in skeletal muscle, time to rise from floor, and time of 10-meter walk/run. Additional efficacy outcome measures included time of 100-meter walk/run, and time to ascend 4 steps. Results of micro-dystrophin measured by western blot are presented in Table 5 [see Clinical Pharmacology (12.2)].

Table 8: Key Demographic and Baseline Characteristics for Study 3
Characteristic | ELEVIDYS (n=63) | Placebo (n=62)
Race (%) Asian/Black or African American/ White/Multiple/Other/Not Reported | 13/0/78/2/3/5 | 18/3/74/0/2/3
Ethnicity (%) Hispanic or Latino/Not Hispanic or Latino/ Not Reported/Unknown | 24/75/0/2 | 13/86/2/0
Mean age [range] (years) | 6.0 [4.1 to 7.9] | 6.1 [4.0 to 7.9]
Mean weight [range] (kg) | 21.3 [13.5 to 38.5] | 22.4 [14.4 to 41.6]
Mean NSAA total score [range] | 23.10 [14 to 32] | 22.82 [15.5 to 30]
Mean time to rise from floor [range] (seconds) | 3.52 [1.9 to 5.8] | 3.60 [2.3 to 5]
Mean time of 10-meter walk/run [range] (seconds) | 4.82 [3.2 to 6.9] | 4.92 [3.7 to 7]
Mean time of 100-meter walk/run [range] (seconds) | 60.67 [38.0 to 129.2] | 63.01 [38.7 to 118.1]
Mean time to ascend 4 steps [range] (seconds) | 3.17 [1.6 to 7.1] | 3.37 [1.5 to 7.1]

The change in NSAA total score was assessed from baseline to Week 52 after infusion of ELEVIDYS or placebo. The difference between the ELEVIDYS (n=63) and placebo groups (n=61) was not statistically significant (p=0.24). The least squares (LS) mean changes in NSAA total score from baseline to Week 52 was 2.57 (95% confidence interval [CI]: 1.80, 3.34) points for the ELEVIDYS group and 1.92 (95% CI: 1.14, 2.70) points for the placebo group, with a LS mean difference from placebo of 0.65 (95% CI: -0.45, 1.74). Changes of clinical relevance were noted in three secondary efficacy endpoints, including time to rise from the floor, 10-meter walk/run and time to ascend 4 steps.

Table 9: Change from Baseline to Week 52 of Timed Function Tests in Study 3 Part 1
 | ELEVIDYS | Placebo | LS Mean Difference from placebo (95% CI)
Time to rise from the floor (seconds) | n=63 | n=61 | -
LS mean Change (95% CI) | -0.27 (-0.56, 0.02) | 0.37 (0.08, 0.67) | -0.64 (-1.06, -0.23)
Time of 10-meter walk/run (seconds) | n=63 | n=61 | -
LS mean Change (95% CI) | -0.34 (-0.55, -0.14) | 0.08 (-0.13, 0.29) | -0.42 (-0.71, -0.13)
Time of 100-meter walk/run (seconds) | n=59 | n=57 | -
LS mean Change (95% CI) | -6.57 (-10.05, -3.09) | -3.28 (-6.86, 0.29) | -3.29 (-8.28, 1.70)
Time to ascend 4 steps (seconds) | n=62 | n=60 | -
LS mean Change (95% CI) | -0.44 (-0.69, -0.20) | -0.08 (-0.33, 0.17) | -0.36 (-0.71, -0.01)

16 HOW SUPPLIED/STORAGE AND HANDLING

16.1 How Supplied

ELEVIDYS is shipped frozen (≤ -60ºC [-76ºF]) in 10 mL vials.

ELEVIDYS is supplied as a customized kit to meet dosing requirements for each patient [see Dosage and Administration (2.2)]. Each kit contains:

- Ten (10) to seventy (70) single-dose vials of ELEVIDYS
- One alcohol wipe per vial

Each ELEVIDYS pack may contain a maximum of two different drug product lots.

The total number of vials in each kit corresponds to the dosing requirement for the individual patient, based on the patient's body weight, and is specified on the package [see Dosage and Administration (2.2)]. Each kit includes a specified number of ELEVIDYS vials (with a minimum of 10 vials for a patient with 10.0 – 10.4 kg body weight range, and a maximum of 70 vials for a patient with body weight of 69.5 kg and above).

Kit sizes and National Drug Codes (NDC) are provided in Table 10.

Table 10: ELEVIDYS Multi-vial Kits
Patient Weight (kg) | Total Vials per Kit | Total Dose Volume per Kit (mL) | NDC Number
10.0 – 10.4 | 10 | 100 | 60923-501-10
10.5 – 11.4 | 11 | 110 | 60923-502-11
11.5 – 12.4 | 12 | 120 | 60923-503-12
12.5 – 13.4 | 13 | 130 | 60923-504-13
13.5 – 14.4 | 14 | 140 | 60923-505-14
14.5 – 15.4 | 15 | 150 | 60923-506-15
15.5 – 16.4 | 16 | 160 | 60923-507-16
16.5 – 17.4 | 17 | 170 | 60923-508-17
17.5 – 18.4 | 18 | 180 | 60923-509-18
18.5 – 19.4 | 19 | 190 | 60923-510-19
19.5 – 20.4 | 20 | 200 | 60923-511-20
20.5 – 21.4 | 21 | 210 | 60923-512-21
21.5 – 22.4 | 22 | 220 | 60923-513-22
22.5 – 23.4 | 23 | 230 | 60923-514-23
23.5 – 24.4 | 24 | 240 | 60923-515-24
24.5 – 25.4 | 25 | 250 | 60923-516-25
25.5 – 26.4 | 26 | 260 | 60923-517-26
26.5 – 27.4 | 27 | 270 | 60923-518-27
27.5 – 28.4 | 28 | 280 | 60923-519-28
28.5 – 29.4 | 29 | 290 | 60923-520-29
29.5 – 30.4 | 30 | 300 | 60923-521-30
30.5 – 31.4 | 31 | 310 | 60923-522-31
31.5 – 32.4 | 32 | 320 | 60923-523-32
32.5 – 33.4 | 33 | 330 | 60923-524-33
33.5 – 34.4 | 34 | 340 | 60923-525-34
34.5 – 35.4 | 35 | 350 | 60923-526-35
35.5 – 36.4 | 36 | 360 | 60923-527-36
36.5 – 37.4 | 37 | 370 | 60923-528-37
37.5 – 38.4 | 38 | 380 | 60923-529-38
38.5 – 39.4 | 39 | 390 | 60923-530-39
39.5 – 40.4 | 40 | 400 | 60923-531-40
40.5 – 41.4 | 41 | 410 | 60923-532-41
41.5 – 42.4 | 42 | 420 | 60923-533-42
42.5 – 43.4 | 43 | 430 | 60923-534-43
43.5 – 44.4 | 44 | 440 | 60923-535-44
44.5 – 45.4 | 45 | 450 | 60923-536-45
45.5 – 46.4 | 46 | 460 | 60923-537-46
46.5 – 47.4 | 47 | 470 | 60923-538-47
47.5 – 48.4 | 48 | 480 | 60923-539-48
48.5 – 49.4 | 49 | 490 | 60923-540-49
49.5 – 50.4 | 50 | 500 | 60923-541-50
50.5 – 51.4 | 51 | 510 | 60923-542-51
51.5 – 52.4 | 52 | 520 | 60923-543-52
52.5 – 53.4 | 53 | 530 | 60923-544-53
53.5 – 54.4 | 54 | 540 | 60923-545-54
54.5 – 55.4 | 55 | 550 | 60923-546-55
55.5 – 56.4 | 56 | 560 | 60923-547-56
56.5 – 57.4 | 57 | 570 | 60923-548-57
57.5 – 58.4 | 58 | 580 | 60923-549-58
58.5 – 59.4 | 59 | 590 | 60923-550-59
59.5 – 60.4 | 60 | 600 | 60923-551-60
60.5 – 61.4 | 61 | 610 | 60923-552-61
61.5 – 62.4 | 62 | 620 | 60923-553-62
62.5 – 63.4 | 63 | 630 | 60923-554-63
63.5 – 64.4 | 64 | 640 | 60923-555-64
64.5 – 65.4 | 65 | 650 | 60923-556-65
65.5 – 66.4 | 66 | 660 | 60923-557-66
66.5 – 67.4 | 67 | 670 | 60923-558-67
67.5 – 68.4 | 68 | 680 | 60923-559-68
68.5 – 69.4 | 69 | 690 | 60923-560-69
69.5 and above | 70 | 700 | 60923-561-70

A 10 mL single-dose vial carton for ELEVIDYS (NDC 60923-562-01) is not sold individually.

16.2 Storage and Handling

- ELEVIDYS is shipped and delivered at ≤ −60ºC [−76ºF].
- ELEVIDYS can be refrigerated for up to 14 days when stored at 2°C to 8°C (36º F to 46º F) in the upright position.
- Do not refreeze.
- Do not shake.
- Do not place back in the refrigerator once brought to room temperature.
- Follow local guidelines on handling of biological waste.

17 PATIENT COUNSELING INFORMATION

Advise the patient to read the FDA-approved Medication Guide.

Provide a copy of the Medication Guide and review the contents with the patient.

Inform patients or caregivers that:

- ELEVIDYS can increase certain liver enzyme levels and cause acute serious liver injury or acute liver failure, and death. Management of acute serious liver injury may require hospitalization. Patients will receive oral corticosteroid medication before and after infusion with ELEVIDYS. Weekly blood tests will be required to monitor liver enzyme levels for 3 months after treatment. Contact a healthcare provider immediately if the patient's skin and/or whites of the eyes appear yellowish, if the patient misses a dose of corticosteroid or vomits it up, or if the patient experiences a change in mental status [see Warnings and Precautions (5.1)].
- Due to the concomitant administration of corticosteroids, an infection (e.g., cold, flu, gastroenteritis, otitis media, bronchiolitis, pneumonia, etc.) before or after ELEVIDYS infusion could lead to more serious complications, including death. Contact a healthcare provider immediately if symptoms suggestive of infection are observed (e.g., coughing, wheezing, sneezing, runny nose, sore throat, or fever) [see Warnings and Precautions (5.2)].
- Myocarditis (inflammation of the heart) has been observed within days to more than a year following ELEVIDYS infusion. Weekly monitoring of troponin-I for the first month after treatment is required. Contact a healthcare provider immediately if the patient begins to experience chest pain and/or shortness of breath [see Warnings and Precautions (5.3)].
- Infusion-related reactions including hypersensitivity and anaphylaxis have occurred during and after ELEVIDYS infusion. Possible symptoms of infusion-related reactions are fast heart rate, fast breathing, swollen lips, being short of breath, nostrils widening, hives, red and blotchy skin, itchy or inflamed lips, rash, vomiting, nausea, chills and fever. Contact a healthcare provider immediately if the patient experiences such a reaction [see Warnings and Precautions (5.4)].
- Immune-mediated myositis (an immune response affecting muscles) was observed in some patients following ELEVIDYS infusion. Contact a physician immediately if the patient experiences any unexplained increased muscle pain, tenderness, or weakness, including difficulty swallowing, difficulty breathing or difficulty speaking, as these may be symptoms of myositis [see Warnings and Precautions (5.5)].
- Patient's immunizations should be up to date with current immunization guidelines prior to initiation of the corticosteroid regimen required before ELEVIDYS infusion. Vaccinations should be completed at least 4 weeks prior to initiation of the corticosteroid regimen [see Drug Interactions (7)].
- Vector shedding of ELEVIDYS occurs primarily through body waste. Practice proper hand hygiene, such as hand washing, when coming into direct contact with patient body waste. Place potentially contaminated materials that may have the patient's bodily fluids/waste in a sealable bag and dispose into regular trash. These precautions should be followed for one month after ELEVIDYS infusion.

Manufactured for: Sarepta Therapeutics, Inc.
Cambridge, MA 02142 USA
U.S. license number 2308

SAREPTA, SAREPTA THERAPEUTICS and ELEVIDYS are trademarks of Sarepta Therapeutics, Inc.
©2025 Sarepta Therapeutics, Inc.

Elevidys
delandistrogene
moxeparvovec-rokl
suspension for intracenous infusion

MEDICATION GUIDE
ELEVIDYS (Ah-LEV-ah-dis)
(delandistrogene moxeparvovec-rokl)
suspension, for intravenous use

What is the most important information that you/your child should know about ELEVIDYS?

1. Rapid serious liver injury and rapid liver failure. ELEVIDYS can increase certain liver lab test levels and cause rapid serious liver injury, rapid liver failure, and death. Complication of blood clots in the blood vessel in the abdomen that helps carry blood from the intestines to the liver has happened. Patients with preexisting liver problems may be at higher risk.
  - You/your child will receive oral corticosteroid medication before and after ELEVIDYS infusion and will need weekly blood tests to monitor liver function for 3 months or longer after treatment.
  - For at least 2 months following ELEVIDYS infusion, stay close to a healthcare facility that your/your child's doctor recommends.
  - Contact your/your child's doctor immediately if your/your child's skin and/or whites of the eyes appear yellowish or if your/your child misses a dose of corticosteroid or vomits it up.
2. Serious Infection. Because you/your child will be taking corticosteroids as part of ELEVIDYS treatment, this may lower the ability of your/your child's immune system to fight infections and make it easier to get an infection. Getting an infection (like a cold, flu, stomach flu, ear infection, chest infection) before or after ELEVIDYS infusion could lead to more serious health problems, including death. Contact your/your child's doctor right away if you notice any signs of infection such as:
  - coughing
  - wheezing
  - sneezing
  - runny nose
  - sore throat
  - fever
  - Vaccinations should be completed at least 4 weeks before starting the corticosteroids that are part of the ELEVIDYS treatment.
  - ELEVIDYS should not be given if you have/your child has an infection.
3. Inflammation of the heart muscle (Myocarditis). Serious and life-threatening inflammation of the heart muscle has happened following ELEVIDYS infusion. In individuals who develop inflammation of the heart muscle after receiving ELEVIDYS, they may be at a higher risk of serious complications if they already had a heart condition that has affected how well the heart pumps.
  You/Your child will need weekly blood tests for a heart protein that can detect damage to muscle cells in the heart (troponin-I) for the first month after ELEVIDYS infusion. Contact your/your child's doctor right away if you notice:
  - chest pain
  - trouble breathing or shortness of breath
4. Infusion-related reactions. Reactions from the infusion, including serious allergic reactions, may happen during or after ELEVIDYS infusion. Contact your/your child's doctor right away if you notice:
  - fast heart rate
  - fast breathing
  - swollen lips
  - shortness of breath
  - nostrils widening
  - hives
  - red and blotchy skin
  - itchy or inflamed lips
  - rash
  - vomiting
  - nausea
  - chills
  - fever
5. Immune response affecting muscles (Immune-mediated myositis). Immune response affecting muscles, including serious and life-threatening reactions, has happened in patients about 1 month after receiving ELEVIDYS infusion. Contact your/your child's doctor right away if you notice:
  - Unexplained increased muscle pain
  - Tenderness
  - Weakness, including trouble swallowing, breathing or speaking

See “What are the possible side effects of ELEVIDYS?” for more information about side effects.

What is ELEVIDYS?
ELEVIDYS is a prescription gene therapy used to treat ambulatory individuals at least 4 years old with Duchenne muscular dystrophy (DMD) who have a confirmed mutation in the DMD gene.
ELEVIDYS is not recommended for individuals with:

- Preexisting liver problems or liver infection because of the high risk of rapid serious liver injury and rapid liver failure
- Recent vaccination (within 4 weeks of ELEVIDYS treatment)
- Current or recent infections (within 4 weeks of ELEVIDYS treatment)

Who should not take ELEVIDYS?
You/Your child should not receive ELEVIDYS if they have a certain type of genetic mutation, called a deletion, involving any portion of or the entire exon 8 and/or exon 9 in the DMD gene.

Before taking ELEVIDYS, tell your child's doctor about all your child's medical conditions, including if they have:

- preexisting liver problems
- current or recent infection
- recent vaccinations (within 4 weeks)

How should your child receive ELEVIDYS?

- Before receiving ELEVIDYS, you/your child will need to get blood tests to check:
  - the amount of antibodies to ELEVIDYS
  - liver function
  - platelets, which is a kind of blood cell that helps you stop bleeding
  - heart protein
- Your/Your child's healthcare provider will give ELEVIDYS into a vein of the arm through an intravenous (IV) line that may last around 1 to 2 hours or longer.
- Your/Your child's healthcare provider will check on you/your child during and at least 3 hours after the infusion for infusion-related reactions. See “What is the most important information I should know about ELEVIDYS?” If an infusion-related reaction occurs during their ELEVIDYS infusion, your/your child's healthcare provider may decide to give ELEVIDYS more slowly or stop the infusion.

What are the possible side effects of ELEVIDYS?

- ELEVIDYS can cause serious side effects. See “What is the most important information I should know about ELEVIDYS?”
- The most common side effects in individuals treated with ELEVIDYS include:
  - vomiting
  - nausea
  - liver injury
  - fever
  - lower number of platelets, which is a kind of blood cell that helps you stop bleeding
  - higher levels of heart protein that can detect damage to muscle cells in the heart (troponin-I)

Tell your/your child's doctor about any side effects that bother you/your child or that do not go away. These are not all the possible side effects of ELEVIDYS.
Call your doctor for medical advice about side effects. You may report side effects to FDA at 1-800-FDA-1088.
You may also report side effects to Sarepta Therapeutics, Inc. at 1-888-727-3782.

What should you/your child avoid after receiving ELEVIDYS?

- Avoid taking new medications that are known to damage the liver as this may make liver problems worse. Tell your doctor about all the medicines you/your child takes, including prescription and over-the counter medicines, vitamins, and herbal supplements.
- Discuss with your/your child's doctor before receiving a vaccine after ELEVIDYS treatment.
- Avoid missing any dose of corticosteroids. Contact your/your child's doctor immediately if this happens.

See “What is the most important information I should know about ELEVIDYS?”

General information about the safe and effective use of ELEVIDYS.
Medicines are sometimes prescribed for purposes other than those listed in a Medication Guide. You can ask your/your child's pharmacist or doctor for information about ELEVIDYS that is written for health professionals.

What are the ingredients in ELEVIDYS?
Active ingredients: delandistrogene moxeparvovec-rokl
Inactive ingredients: sodium chloride, tromethamine hydrochloride, tromethamine, magnesium chloride, poloxamer 188
Manufactured for: Sarepta Therapeutics, Inc. Cambridge, MA 02142 USA U.S. license number 2308
SAREPTA, SAREPTA THERAPEUTICS and ELEVIDYS are trademarks of Sarepta Therapeutics, Inc.
©2025 Sarepta Therapeutics, Inc.

This Medication Guide has been approved by the U.S. Food and Drug Administration. Revised: 11/2025

Principal Display Panel –Carton Kit Label

delandistrogene moxeparvovec-rokl

ELEVIDYS

1.33 x 10^13 vector genomes/mL

Suspension for Infusion

For Intravenous Use

See enclosed prescribing information for dosage
and administration instructions.

Preservative-free

Discard unused
portion

Single patient use

Store unopened vials at ≤-60°C (-76°F) in
original carton.

Unopened vials can be refrigerated for up to

14 days at 2°C to 8°C (36°F to 46°F).

DO NOT REFREEZE

DO NOT SHAKE

Rx Only

Manufactured for Sarepta Therapeutics, Inc.,
Cambridge, MA 02142 USA

US License No. 2308

SAREPTA

THERAPEUTICS

PACKAGE LABEL

Principal Display Panel -10 mL 10 count Carton Label

NDC: 60923-501-10

delandistrogene
moxeparvovec-rokl

ELEVIDYS

Patient Weight:

10.0 - 10.4 kg

Kit Contents:

10 x 10 mL vials

10 alcohol swabs

PACKAGE LABEL

Principal Display Panel -10 mL 11 count Carton Label

NDC: 60923-502-11

delandistrogene
moxeparvovec-rokl
ELEVIDYS

Patient Weight:

10.5 - 11.4 kg

Kit Contents:

11 x 10 mL vials

11 alcohol swabs

PACKAGE LABEL

Principal Display Panel -10 mL 12 count Carton Label

NDC: 60923-503-12

delandistrogene
moxeparvovec-rokl

ELEVIDYS

Patient Weight:

11.5 - 12.4 kg

Kit Contents:

12 x 10 mL vials

12 alcohol swabs

PACKAGE LABEL

Principal Display Panel -10 mL 13 count Carton Label

NDC: 60923-504-13

delandistrogene
moxeparvovec-rokl
ELEVIDYS

Patient Weight:

12.5 - 13.4 kg

Kit Contents:

13 x 10 mL vials

13 alcohol swabs

PACKAGE LABEL

Principal Display Panel -10 mL 14 count Carton Label

NDC: 60923-505-14

delandistrogene
moxeparvovec-rokl
ELEVIDYS

Patient Weight:

13.5 - 14.4 kg

Kit Contents:

14 x 10 mL vials

14 alcohol swabs

PACKAGE LABEL

Principal Display Panel -10 mL 15 count Carton Label

NDC: 60923-506-15

delandistrogene
moxeparvovec-rokl
ELEVIDYS

Patient Weight:

14.5 - 15.4 kg

Kit Contents:

15 x 10 mL vials

15 alcohol swabs

PACKAGE LABEL

Principal Display Panel -10 mL 16 count Carton Label

NDC: 60923-507-16

delandistrogene
moxeparvovec-rokl
ELEVIDYS

Patient Weight:

15.5 - 16.4 kg

Kit Contents:

16 x 10 mL vials

16 alcohol swabs

PACKAGE LABEL

Principal Display Panel -10 mL 17 count Carton Label

NDC: 60923-508-17

delandistrogene
moxeparvovec-rokl
ELEVIDYS

Patient Weight:

16.5 - 17.4 kg

Kit Contents:

17 x 10 mL vials

17 alcohol swabs

PACKAGE LABEL

Principal Display Panel -10 mL 18 count Carton Label

NDC: 60923-509-18

delandistrogene
moxeparvovec-rokl
ELEVIDYS

Patient Weight:

17.5 - 18.4 kg

Kit Contents:

18 x 10 mL vials

18 alcohol swabs

PACKAGE LABEL

Principal Display Panel -10 mL 19 count Carton Label

NDC: 60923-510-19

delandistrogene
moxeparvovec-rokl
ELEVIDYS

Patient Weight:

18.5 - 19.4 kg

Kit Contents:

19 x 10 mL vials

19 alcohol swabs

PACKAGE LABEL

Principal Display Panel -10 mL 20 count Carton Label

NDC: 60923-511-20

delandistrogene
moxeparvovec-rokl

ELEVIDYS

Patient Weight:

19.5 - 20.4 kg

Kit Contents:

20 x 10 mL vials

20 alcohol swabs

PACKAGE LABEL

Principal Display Panel -10 mL 21 count Carton Label

NDC: 60923-512-21

delandistrogene
moxeparvovec-rokl
ELEVIDYS

Patient Weight:

20.5 - 21.4 kg

Kit Contents:

21 x 10 mL vials

21 alcohol swabs

PACKAGE LABEL

Principal Display Panel -10 mL 22 count Carton Label

NDC: 60923-513-22

delandistrogene
moxeparvovec-rokl
ELEVIDYS

Patient Weight:

21.5 - 22.4 kg

Kit Contents:

22 x 10 mL vials

22 alcohol swabs

PACKAGE LABEL

Principal Display Panel -10 mL 23 count Carton Label

NDC: 60923-514-23

delandistrogene
moxeparvovec-rokl
ELEVIDYS

Patient Weight:

22.5 - 23.4 kg

Kit Contents:

23 x 10 mL vials

23 alcohol swabs

PACKAGE LABEL

Principal Display Panel -10 mL 24 count Carton Label

NDC: 60923-515-24

delandistrogene
moxeparvovec-rokl
ELEVIDYS

Patient Weight:

23.5 - 24.4 kg

Kit Contents:

24 x 10 mL vials

24 alcohol swabs

PACKAGE LABEL

Principal Display Panel -10 mL 25 count Carton Label

NDC: 60923-516-25

delandistrogene
moxeparvovec-rokl
ELEVIDYS

Patient Weight:

24.5 - 25.4 kg

Kit Contents:

25 x 10 mL vials

25 alcohol swabs

PACKAGE LABEL

Principal Display Panel -10 mL 26 count Carton Label

NDC: 60923-517-26

delandistrogene
moxeparvovec-rokl
ELEVIDYS

Patient Weight:

25.5 - 26.4 kg

Kit Contents:

26 x 10 mL vials

26 alcohol swabs

PACKAGE LABEL

Principal Display Panel -10 mL 27 count Carton Label

NDC: 60923-518-27

delandistrogene
moxeparvovec-rokl
ELEVIDYS

Patient Weight:

26.5 - 27.4 kg

Kit Contents:

27 x 10 mL vials

27 alcohol swabs

PACKAGE LABEL

Principal Display Panel -10 mL 28 count Carton Label

NDC: 60923-519-28

delandistrogene
moxeparvovec-rokl
ELEVIDYS

Patient Weight:

27.5 - 28.4 kg

Kit Contents:

28 x 10 mL vials

28 alcohol swabs

PACKAGE LABEL

Principal Display Panel -10 mL 29 count Carton Label

NDC: 60923-520-29

delandistrogene
moxeparvovec-rokl
ELEVIDYS

Patient Weight:

28.5 - 29.4 kg

Kit Contents:

29 x 10 mL vials

29 alcohol swabs

PACKAGE LABEL

Principal Display Panel -10 mL 30 count Carton Label

NDC: 60923-521-30

delandistrogene
moxeparvovec-rokl
ELEVIDYS

Patient Weight:

29.5 - 30.4 kg

Kit Contents:

30 x 10 mL vials

30 alcohol swabs

PACKAGE LABEL

Principal Display Panel -10 mL 31 count Carton Label

NDC: 60923-522-31

delandistrogene
moxeparvovec-rokl
ELEVIDYS

Patient Weight:

30.5 - 31.4 kg

Kit Contents:

31 x 10 mL vials

31 alcohol swabs

PACKAGE LABEL

Principal Display Panel -10 mL 32 count Carton Label

NDC: 60923-523-32

delandistrogene
moxeparvovec-rokl
ELEVIDYS

Patient Weight:

31.5 - 32.4 kg

Kit Contents:

32 x 10 mL vials

32 alcohol swabs

PACKAGE LABEL

Principal Display Panel -10 mL 33 count Carton Label

NDC: 60923-524-33

delandistrogene
moxeparvovec-rokl
ELEVIDYS

Patient Weight:

32.5 - 33.4 kg

Kit Contents:

33 x 10 mL vials

33 alcohol swabs

PACKAGE LABEL

Principal Display Panel -10 mL 34 count Carton Label

NDC: 60923-525-34

delandistrogene
moxeparvovec-rokl
ELEVIDYS

Patient Weight:

33.5 - 34.4 kg

Kit Contents:

34 x 10 mL vials

34 alcohol swabs

PACKAGE LABEL

Principal Display Panel -10 mL 35 count Carton Label

NDC: 60923-526-35

delandistrogene
moxeparvovec-rokl
ELEVIDYS

Patient Weight:

34.5 - 35.4 kg

Kit Contents:

35 x 10 mL vials

35 alcohol swabs

PACKAGE LABEL

Principal Display Panel -10 mL 36 count Carton Label

NDC: 60923-527-36

delandistrogene
moxeparvovec-rokl
ELEVIDYS

Patient Weight:

35.5 - 36.4 kg

Kit Contents:

36 x 10 mL vials

36 alcohol swabs

PACKAGE LABEL

Principal Display Panel -10 mL 37 count Carton Label

NDC: 60923-528-37

delandistrogene
moxeparvovec-rokl
ELEVIDYS

Patient Weight:

36.5 - 37.4 kg

Kit Contents:

37 x 10 mL vials

37 alcohol swabs

PACKAGE LABEL

Principal Display Panel -10 mL 38 count Carton Label

NDC: 60923-529-38

delandistrogene
moxeparvovec-rokl
ELEVIDYS

Patient Weight:

37.5 - 38.4 kg

Kit Contents:

38 x 10 mL vials

38 alcohol swabs

PACKAGE LABEL

Principal Display Panel -10 mL 39 count Carton Label

NDC: 60923-530-39

delandistrogene
moxeparvovec-rokl
ELEVIDYS

Patient Weight:

38.5 - 39.4 kg

Kit Contents:

39 x 10 mL vials

39 alcohol swabs

PACKAGE LABEL

Principal Display Panel -10 mL 40 count Carton Label

NDC: 60923-531-40

delandistrogene
moxeparvovec-rokl
ELEVIDYS

Patient Weight:

39.5 - 40.4 kg

Kit Contents:

40 x 10 mL vials

40 alcohol swabs

PACKAGE LABEL

Principal Display Panel -10 mL 41 count Carton Label

NDC: 60923-532-41

delandistrogene
moxeparvovec-rokl
ELEVIDYS

Patient Weight:

40.5 - 41.4 kg

Kit Contents:

41 x 10 mL vials

41 alcohol swabs

PACKAGE LABEL

Principal Display Panel -10 mL 42 count Carton Label

NDC: 60923-533-42

delandistrogene
moxeparvovec-rokl
ELEVIDYS

Patient Weight:

41.5 - 42.4 kg

Kit Contents:

42 x 10 mL vials

42 alcohol swabs

PACKAGE LABEL

Principal Display Panel -10 mL 43 count Carton Label

NDC: 60923-534-43

delandistrogene
moxeparvovec-rokl
ELEVIDYS

Patient Weight:

42.5 - 43.4 kg

Kit Contents:

43 x 10 mL vials

43 alcohol swabs

PACKAGE LABEL

Principal Display Panel -10 mL 44 count Carton Label

NDC: 60923-535-44

delandistrogene
moxeparvovec-rokl
ELEVIDYS

Patient Weight:

43.5 - 44.4 kg

Kit Contents:

44 x 10 mL vials

44 alcohol swabs

PACKAGE LABEL

Principal Display Panel -10 mL 45 count Carton Label

NDC: 60923-536-45

delandistrogene
moxeparvovec-rokl
ELEVIDYS

Patient Weight:

44.5 - 45.4 kg

Kit Contents:

45 x 10 mL vials

45 alcohol swabs

PACKAGE LABEL

Principal Display Panel -10 mL 46 count Carton Label

NDC: 60923-537-46

delandistrogene
moxeparvovec-rokl
ELEVIDYS

Patient Weight:

45.5 - 46.4 kg

Kit Contents:

46 x 10 mL vials

46 alcohol swabs

PACKAGE LABEL

Principal Display Panel -10 mL 47 count Carton Label

NDC: 60923-538-47

delandistrogene
moxeparvovec-rokl
ELEVIDYS

Patient Weight:

46.5 - 47.4 kg

Kit Contents:

47 x 10 mL vials

47 alcohol swabs

PACKAGE LABEL

Principal Display Panel -10 mL 48 count Carton Label

NDC: 60923-539-48

delandistrogene
moxeparvovec-rokl
ELEVIDYS

Patient Weight:

47.5 - 48.4 kg

Kit Contents:

48 x 10 mL vials

48 alcohol swabs

PACKAGE LABEL

Principal Display Panel -10 mL 49 count Carton Label

NDC: 60923-540-49

delandistrogene
moxeparvovec-rokl
ELEVIDYS

Patient Weight:

48.5 - 49.4 kg

Kit Contents:

49 x 10 mL vials

49 alcohol swabs

PACKAGE LABEL

Principal Display Panel -10 mL 50 count Carton Label

NDC: 60923-541-50

delandistrogene
moxeparvovec-rokl
ELEVIDYS

Patient Weight:

49.5 - 50.4 kg

Kit Contents:

50 x 10 mL vials

50 alcohol swabs

Principal Display Panel –Carton Kit Label

delandistrogene moxeparvovec-rokl

ELEVIDYS

1.33 x 10^13 vector genomes/mL

Suspension for Infusion

For Intravenous Use

See enclosed prescribing information for dosage
and administration instructions.

Preservative-free

Discard unused
portion

Single patient use

Store unopened vials at ≤-60°C (-76°F) in
original carton.

Unopened vials can be refrigerated for up to

14 days at 2°C to 8°C (36°F to 46°F).

DO NOT REFREEZE

DO NOT SHAKE

Rx Only

Manufactured for Sarepta Therapeutics, Inc.,
Cambridge, MA 02142 USA

US License No. 2308

Principal Display Panel –Vial Label

delandistrogene moxeparvovec-rokl

ELEVIDYS

1.33 x 10^13 vector genomes/mL

Suspension for infusion. Single-dose vial 10 mL.
For intravenous use. Store at ≤ -60°C (-76°F).

Do not refreeze. Do not shake.

Mfg. for: Sarepta Therapeutics, Inc.,
Cambridge, MA 02142 USA
US License No. 2308

Rx Only

NDC 60923-562-01

PACKAGE LABEL

Principal Display Panel -10 mL 51 count Carton Label

NDC: 60923-542-51

delandistrogene
moxeparvovec-rokl
ELEVIDYS

Patient Weight:

50.5 - 51.4 kg

Kit Contents:

51 x 10 mL vials

51 alcohol swabs

PACKAGE LABEL

Principal Display Panel -10 mL 52 count Carton Label

NDC: 60923-543-52

delandistrogene
moxeparvovec-rokl
ELEVIDYS

Patient Weight:

51.5 - 52.4 kg

Kit Contents:

52 x 10 mL vials

52 alcohol swabs

PACKAGE LABEL

Principal Display Panel -10 mL 53 count Carton Label

NDC: 60923-544-53

delandistrogene
moxeparvovec-rokl
ELEVIDYS

Patient Weight:

52.5 - 53.4 kg

Kit Contents:

53 x 10 mL vials

53 alcohol swabs

PACKAGE LABEL

Principal Display Panel -10 mL 54 count Carton Label

NDC: 60923-545-54

delandistrogene
moxeparvovec-rokl
ELEVIDYS

Patient Weight:

53.5 - 54.4 kg

Kit Contents:

54 x 10 mL vials

54 alcohol swabs

PACKAGE LABEL

Principal Display Panel -10 mL 55 count Carton Label

NDC: 60923-546-55

delandistrogene
moxeparvovec-rokl
ELEVIDYS

Patient Weight:

54.5 - 55.4 kg

Kit Contents:

55 x 10 mL vials

55 alcohol swabs

PACKAGE LABEL

Principal Display Panel -10 mL 56 count Carton Label

NDC: 60923-547-56

delandistrogene
moxeparvovec-rokl
ELEVIDYS

Patient Weight:

55.5 - 56.4 kg

Kit Contents:

56 x 10 mL vials

56 alcohol swabs

PACKAGE LABEL

Principal Display Panel -10 mL 57 count Carton Label

NDC: 60923-548-57

delandistrogene
moxeparvovec-rokl
ELEVIDYS

Patient Weight:

56.5 - 57.4 kg

Kit Contents:

57 x 10 mL vials

57 alcohol swabs

PACKAGE LABEL

Principal Display Panel -10 mL 58 count Carton Label

NDC: 60923-549-58

delandistrogene
moxeparvovec-rokl
ELEVIDYS

Patient Weight:

57.5 - 58.4 kg

Kit Contents:

58 x 10 mL vials

58 alcohol swabs

PACKAGE LABEL

Principal Display Panel -10 mL 59 count Carton Label

NDC: 60923-550-59

delandistrogene
moxeparvovec-rokl
ELEVIDYS

Patient Weight:

58.5 - 59.4 kg

Kit Contents:

59 x 10 mL vials

59 alcohol swabs

PACKAGE LABEL

Principal Display Panel -10 mL 60 count Carton Label

NDC: 60923-551-60

delandistrogene
moxeparvovec-rokl
ELEVIDYS

Patient Weight:

59.5 - 60.4 kg

Kit Contents:

60 x 10 mL vials

60 alcohol swabs

PACKAGE LABEL

Principal Display Panel -10 mL 61 count Carton Label

NDC: 60923-552-61

delandistrogene
moxeparvovec-rokl
ELEVIDYS

Patient Weight:

60.5 - 61.4 kg

Kit Contents:

61 x 10 mL vials

61 alcohol swabs

PACKAGE LABEL

Principal Display Panel -10 mL 62 count Carton Label

NDC: 60923-553-62

delandistrogene
moxeparvovec-rokl
ELEVIDYS

Patient Weight:

61.5 - 62.4 kg

Kit Contents:

62 x 10 mL vials

62 alcohol swabs

PACKAGE LABEL

Principal Display Panel -10 mL 63 count Carton Label

NDC: 60923-554-63

delandistrogene
moxeparvovec-rokl
ELEVIDYS

Patient Weight:

62.5 - 63.4 kg

Kit Contents:

63 x 10 mL vials

63 alcohol swabs

PACKAGE LABEL

Principal Display Panel -10 mL 64 count Carton Label

NDC: 60923-555-64

delandistrogene
moxeparvovec-rokl
ELEVIDYS

Patient Weight:

63.5 - 64.4 kg

Kit Contents:

64 x 10 mL vials

64 alcohol swabs

PACKAGE LABEL

Principal Display Panel -10 mL 65 count Carton Label

NDC: 60923-556-65

delandistrogene
moxeparvovec-rokl
ELEVIDYS

Patient Weight:

64.5 - 65.4 kg

Kit Contents:

65 x 10 mL vials

65 alcohol swabs

PACKAGE LABEL

Principal Display Panel -10 mL 66 count Carton Label

NDC: 60923-557-66

delandistrogene
moxeparvovec-rokl
ELEVIDYS

Patient Weight:

65.5 - 66.4 kg

Kit Contents:

66 x 10 mL vials

66 alcohol swabs

PACKAGE LABEL

Principal Display Panel -10 mL 67 count Carton Label

NDC: 60923-558-67

delandistrogene
moxeparvovec-rokl
ELEVIDYS

Patient Weight:

66.5 - 67.4 kg

Kit Contents:

67 x 10 mL vials

67 alcohol swabs

PACKAGE LABEL

Principal Display Panel -10 mL 68 count Carton Label

NDC: 60923-559-68

delandistrogene
moxeparvovec-rokl
ELEVIDYS

Patient Weight:

67.5 - 68.4 kg

Kit Contents:

68 x 10 mL vials

68 alcohol swabs

PACKAGE LABEL

Principal Display Panel -10 mL 69 count Carton Label

NDC: 60923-560-69

delandistrogene
moxeparvovec-rokl
ELEVIDYS

Patient Weight:

68.5 - 69.4 kg

Kit Contents:

69 x 10 mL vials

69 alcohol swabs

PACKAGE LABEL

Principal Display Panel -10 mL 70 count Carton Label

NDC: 60923-561-70

delandistrogene
moxeparvovec-rokl
ELEVIDYS

Patient Weight:

69.5 kg and
above

Kit Contents:

70 x 10 mL vials

70 alcohol swabs

Principal Display Panel – 10 mL Vial Label

NDC: 60923-562-01

delandistrogene moxeparvovec-rokl

ELEVIDYS

1.33 x 10^13 vector genomes/mL

Suspension for Infusion

For Intravenous Use

See enclosed prescribing information
for dosage and administration instructions.

Rx Only

Single-dose

1 vial